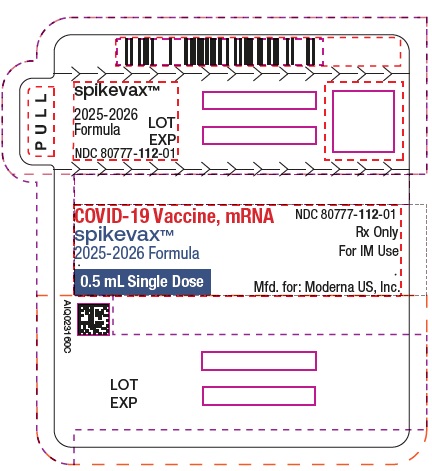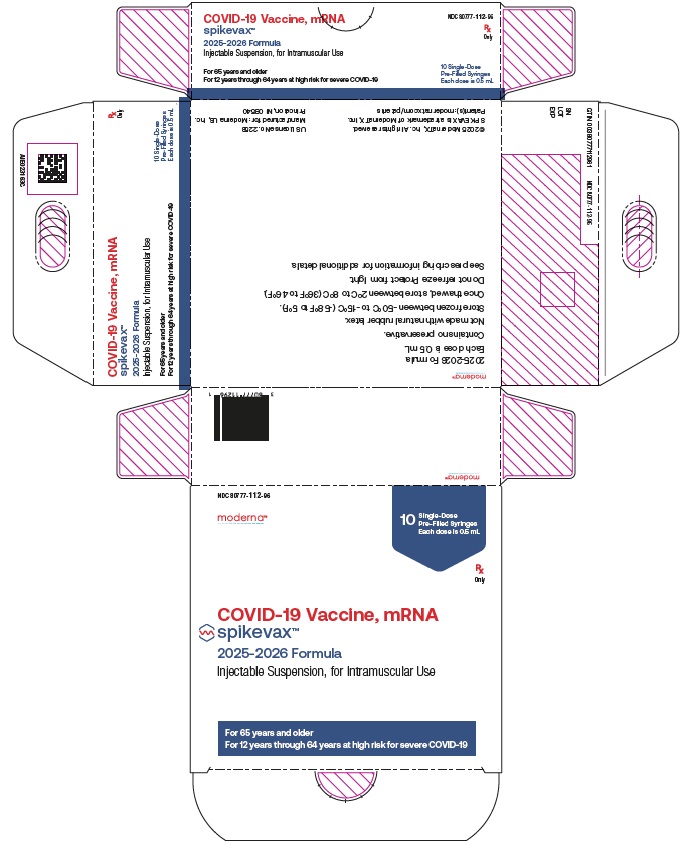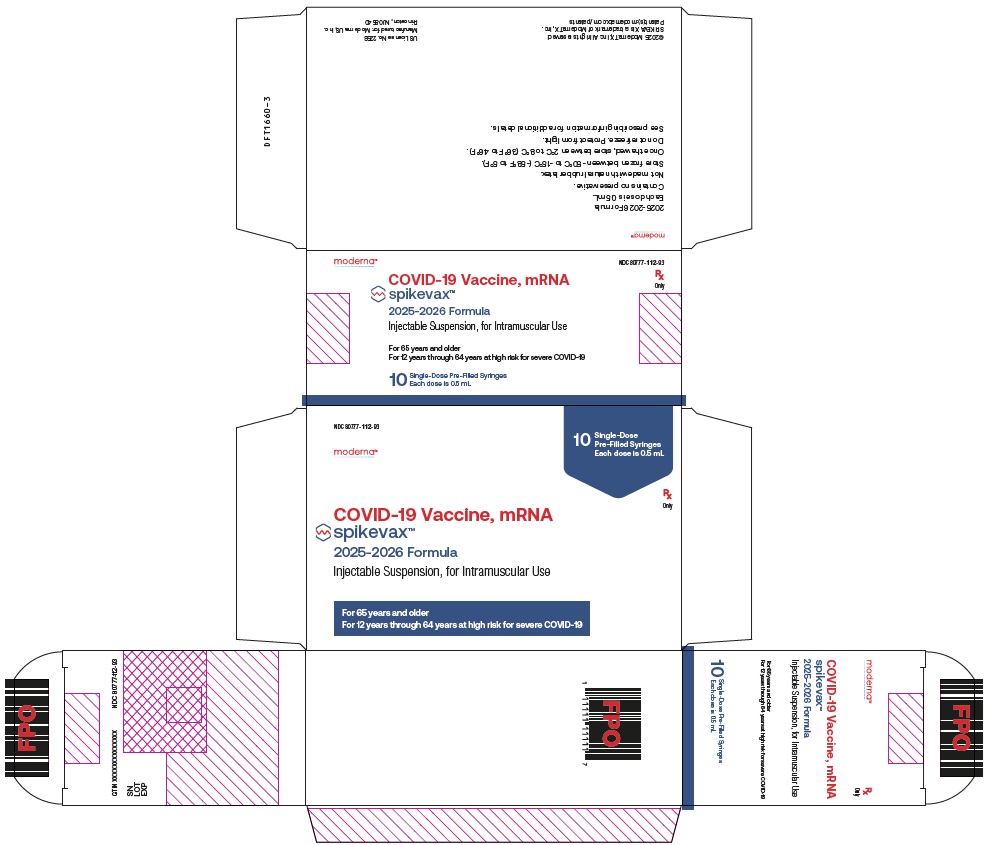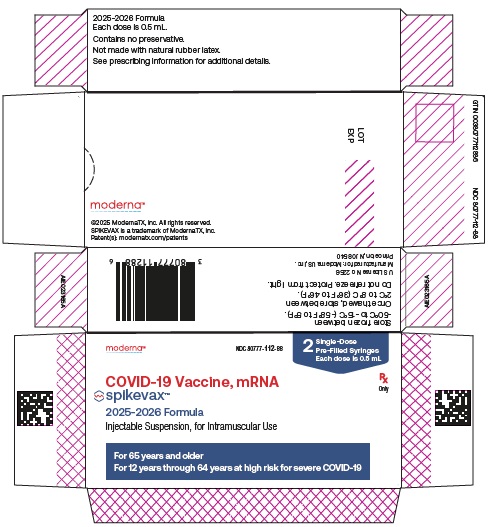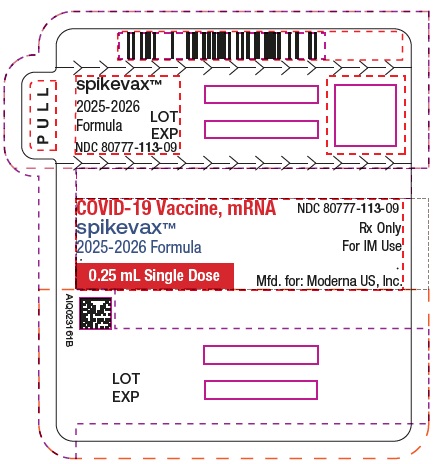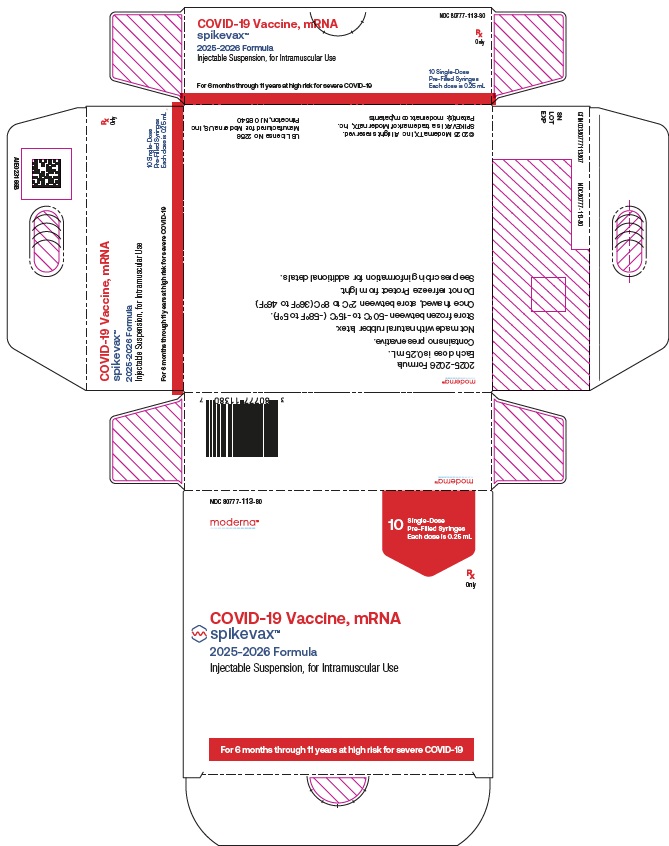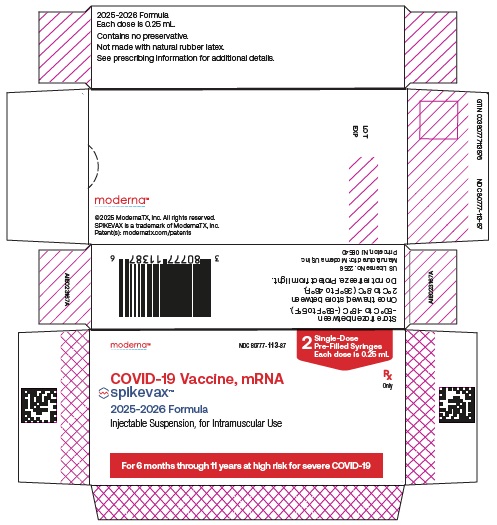 DRUG LABEL: Spikevax
NDC: 80777-110 | Form: INJECTION, SUSPENSION
Manufacturer: Moderna US, Inc.
Category: other | Type: VACCINE LABEL
Date: 20250827

ACTIVE INGREDIENTS: CX-046684 50 ug/0.5 mL

HIGHLIGHTS OF PRESCRIBING INFORMATION

These highlights do not include all the information needed to use SPIKEVAX safely and effectively. See full prescribing information for SPIKEVAX.
SPIKEVAX (COVID-19 Vaccine, mRNA) injectable suspension, for intramuscular use
2025-2026 Formula
Initial U.S. Approval: 2022

RECENT MAJOR CHANGES

Indications and Usage (1)

Dosage and Administration,

Preparation for Administration (2.1)

Dosing and Schedule (2.3)

Warnings and Precautions,

Myocarditis and Pericarditis (5.2)

7/2025

7/2025

7/2025

6/2025

1 INDICATIONS AND USAGE

SPIKEVAX is a vaccine indicated for active immunization to prevent coronavirus disease 2019 (COVID-19) caused by severe acute respiratory syndrome coronavirus 2 (SARS-CoV-2).

SPIKEVAX is approved for use in individuals who are:

- 65 years of age and older, or
- 6 months through 64 years of age with at least one underlying condition that puts them at high risk for severe outcomes from COVID-19. (1)

2 DOSAGE AND ADMINISTRATION

For intramuscular use.

Individuals 6 Months Through 23 Months of Age by Number of Previous Doses of Moderna COVID-19 Vaccine Received (2.3)

Number of Previous Doses of Moderna COVID-19 Vaccine(s)a | SPIKEVAX; Dosing Regimen, Dose and Schedule
0b | 2 doses,c 0.25 mL each; Dose 1: month 0 Dose 2: month 1
1 | Single Dose, 0.25 mL; One month after receipt of a previous dose of Moderna COVID-19 vaccinea
≥2 | Single dose, 0.25 mL; ≥2 months after receipt of the last previous dose of Moderna COVID-19 vaccinea
a Previous dose refers to a dose of any authorized Moderna COVID-19 Vaccine.
b Not previously vaccinated with any COVID-19 vaccine.
c Individuals turning from 23 months to 2 years of age during the vaccination series should receive both doses with SPIKEVAX.

Individuals 2 Years of Age and Older Irrespective of COVID-19 Vaccination Status (2.3)

Age | SPIKEVAX; Dosing Regimen, Dose and Schedule
2 years through; 11 years | Single dose, 0.25 mL
12 years and older | Single dose, 0.5 mL
If previously vaccinated with any COVID-19 vaccine, administer the dose ≥2 months after the last dose of COVID-19 vaccine

3 DOSAGE FORMS AND STRENGTHS

SPIKEVAX is an injectable suspension.

6 months through 11 years of age: A single dose is 0.25 mL. (3)

12 years of age and older: A single dose is 0.5 mL. (3)

4 CONTRAINDICATIONS

Do not administer SPIKEVAX to individuals with a known history of severe allergic reaction (e.g., anaphylaxis) to any component of SPIKEVAX or to individuals who had a severe allergic reaction (e.g., anaphylaxis) following a previous dose of a Moderna COVID-19 vaccine. (4)

5 WARNINGS AND PRECAUTIONS

Analyses of postmarketing data from use of authorized or approved mRNA COVID-19 vaccines, including SPIKEVAX, have demonstrated increased risks of myocarditis and pericarditis, with onset of symptoms typically in the first week following vaccination. The observed risk has been highest in males 12 years through 24 years of age. (5.2)

6 ADVERSE REACTIONS

Most commonly reported adverse reactions following administration of SPIKEVAX or Moderna COVID-19 Vaccine, Bivalent containing the same amount of mRNA as the SPIKEVAX 2025-2026 Formula (≥10%):

- Participants 6 months through 36 months of age: irritability/crying (up to 82.8%), pain at the injection site (up to 77.2%), sleepiness (up to 52.2%), loss of appetite (up to 46.5%), fever (up to 26.8%), erythema (up to 19.2%), swelling at the injection site (up to 19.2%), and axillary (or groin) swelling/tenderness (up to 12.2%). (6)
- Participants 37 months through 11 years of age: pain at the injection site (up to 98.4%), fatigue (up to 73.2%), headache (up to 62.2%), myalgia (up to 35.3%), chills (up to 34.6%), nausea/vomiting (up to 29.3%), axillary (or groin) swelling/tenderness (up to 27.0%), fever (up to 25.8%), erythema (up to 24.1%), swelling at the injection site (up to 22.3%), and arthralgia (up to 21.3%). (6)
- Participants 12 years through 17 years of age: pain at the injection site (up to 90.6%), fatigue (up to 58.1%), headache (up to 56.3%), myalgia (up to 40.1%), chills (up to 30.2%), axillary swelling/tenderness (up to 27.8%), arthralgia (up to 23.9%), nausea/vomiting (up to 17.9%), and swelling at the injection site (up to 13.3%). (6)
- Participants 18 years through 64 years of age: pain at injection site (up to 86.3%), fatigue (up to 62.0%), headache (up to 58.9%), myalgia (up to 49.6%), arthralgia (up to 41.9%), chills (up to 40.3%), axillary swelling/tenderness (up to 24.8%), and nausea/vomiting (up to 16.7%). (6)
- Participants 65 years of age and older: pain at injection site (up to 76.3%), fatigue (up to 58.1%), myalgia (up to 47.4%), headache (up to 42.1%), arthralgia (up to 39.5%), chills (up to 18.4%), and axillary swelling/tenderness (up to 14.3%). (6)

To report SUSPECTED ADVERSE REACTIONS, contact ModernaTX, Inc. at 1-866-663-3762 or VAERS at 1-800-822-7967 or https://vaers.hhs.gov.

FULL PRESCRIBING INFORMATION

1 INDICATIONS AND USAGE

SPIKEVAX is a vaccine indicated for active immunization to prevent coronavirus disease 2019 (COVID-19) caused by severe acute respiratory syndrome coronavirus 2 (SARS-CoV-2).

SPIKEVAX is approved for use in individuals who are:

- 65 years of age and older, or
- 6 months through 64 years of age with at least one underlying condition that puts them at high risk for severe outcomes from COVID-19.

2 DOSAGE AND ADMINISTRATION

For intramuscular use.

2.1 Preparation for Administration

- Verify that the label on the pre-filled syringe states 2025-2026 Formula.
- If pre-filled syringes of SPIKEVAX are frozen, thaw before use following the instructions below.

 | Thaw in Refrigerator; 2°C to 8°C (36°F to 46°F) | Thaw at Room Temperature; 15°C to 25°C (59°F to 77°F)
Carton of 10 syringes | Thaw for 2 hours and 40 minutes | Thaw for 1 hour and 20 minutes
Carton of 2 syringes | Thaw for 1 hour and 40 minutes | Thaw for 40 minutes
One syringe; (removed from carton) | Thaw for 1 hour and 40 minutes | Thaw for 40 minutes

- After thawing, do not refreeze.
- Parenteral drug products should be inspected visually for particulate matter and discoloration prior to administration, whenever solution and container permit.
- SPIKEVAX is a white to off-white suspension. It may contain white or translucent product-related particulates. Do not administer if vaccine is discolored or contains other particulate matter.
- Do not shake.
- With tip cap upright, remove tip cap by twisting counterclockwise until tip cap releases. Remove tip cap in a slow, steady motion. Avoid pulling tip cap while twisting.
- Attach the needle by twisting in a clockwise direction until the needle fits securely on the syringe.

2.2 Administration

Administer SPIKEVAX intramuscularly. Discard after single use.

2.3 Dosing and Schedule

Table 1: Individuals 6 Months Through 23 Months of Age by Number of Previous Doses of Moderna COVID-19 Vaccine Received
Number of Previous Doses of Moderna COVID-19 Vaccine(s)a | SPIKEVAX; Dosing Regimen, Dose and Schedule
0b | 2 doses,c 0.25 mL each; Dose 1: month 0; Dose 2: month 1
1 | Single dose, 0.25 mL; One month after receipt of a previous dose of Moderna COVID-19 vaccinea
≥2 | Single dose, 0.25 mL; ≥2 months after receipt of the last previous dose of Moderna COVID-19 vaccinea
a Previous dose refers to a dose of any authorized Moderna COVID-19 Vaccine.
b Not previously vaccinated with any COVID-19 vaccine.
c Individuals turning from 23 months to 2 years of age during the vaccination series should receive both doses with SPIKEVAX.

Table 2: Individuals 2 Years of Age and Older Irrespective of COVID-19 Vaccination Status
Age | SPIKEVAX; Dosing Regimen, Dose and Schedule
2 years through 11 years | Single dose, 0.25 mL
12 years and older | Single dose, 0.5 mL
If previously vaccinated with any COVID-19 vaccine, administer the dose ≥2 months after the last dose of COVID-19 vaccine

3 DOSAGE FORMS AND STRENGTHS

SPIKEVAX is an injectable suspension.

For individuals 6 months through 11 years of age, a single dose is 0.25 mL.

For individuals 12 years of age and older, a single dose is 0.5 mL.

4 CONTRAINDICATIONS

Do not administer SPIKEVAX to individuals with a known history of severe allergic reaction (e.g., anaphylaxis) to any component of SPIKEVAX [see Description (11)] or to individuals who had a severe allergic reaction (e.g., anaphylaxis) following a previous dose of a Moderna COVID-19 vaccine.

5 WARNINGS AND PRECAUTIONS

5.1 Management of Acute Allergic Reactions

Appropriate medical treatment must be immediately available to manage potential anaphylactic reactions following administration of SPIKEVAX.

5.2 Myocarditis and Pericarditis

Analyses of postmarketing data from use of authorized or approved mRNA COVID-19 vaccines, including SPIKEVAX, have demonstrated increased risks of myocarditis and pericarditis, with onset of symptoms typically in the first week following vaccination. The observed risk has been highest in males 12 years through 24 years of age.

Based on analyses of commercial health insurance claims data from inpatient and outpatient settings, the estimated unadjusted incidence of myocarditis and/or pericarditis during the period 1 through 7 days following administration of the 2023-2024 Formula of mRNA COVID-19 vaccines was approximately 8 cases per million doses in individuals 6 months through 64 years of age and approximately 27 cases per million doses in males 12 years through 24 years of age.

Although some individuals with myocarditis and/or pericarditis following administration of mRNA COVID-19 vaccines have required intensive care support, available data suggest that individuals typically have resolution of symptoms within a few days with conservative management.

Follow-up information on cardiovascular outcomes in hospitalized patients who had been diagnosed with COVID-19 vaccine-associated myocarditis is available from a longitudinal retrospective observational study. Most of these patients had received a two-dose primary series of an mRNA COVID-19 vaccine prior to their diagnosis. In this study, at a median follow-up of approximately 5 months post-vaccination, persistence of abnormal cardiac magnetic resonance imaging (CMR) findings that are a marker for myocardial injury was common. The clinical and prognostic significance of these CMR findings is not known^1 [see Adverse Reactions (6.2)].

Information is not yet available about potential long-term sequelae of myocarditis or pericarditis following administration of mRNA COVID-19 vaccines.

The Centers for Disease Control and Prevention (CDC) has published considerations related to myocarditis and pericarditis after vaccination, including for vaccination of individuals with a history of myocarditis or pericarditis (https://www.cdc.gov/vaccines/covid-19/clinical-considerations/myocarditis.html).

5.3 Syncope

Syncope (fainting) may occur in association with administration of injectable vaccines. Procedures should be in place to avoid injury from fainting.

5.4 Altered Immunocompetence

Immunocompromised persons, including individuals receiving immunosuppressive therapy, may have a diminished immune response to SPIKEVAX [see Use in Specific Populations (8.6)].

5.5 Limitations of Vaccine Effectiveness

SPIKEVAX may not protect all vaccine recipients.

6 ADVERSE REACTIONS

In clinical studies contributing to the safety assessment of SPIKEVAX, participants received a single dose, a 2-dose series one month apart (referred to as primary series) and subsequent doses referred to as booster doses, as described in Table 3 below.

Table 3: Clinical Studies
Study | Age | Dosing Regimen | Vaccine Recipients
Study 1; (NCT04470427) | 18 years of age and older | Primary Series: 2 doses (100 mcg mRNA per dose) of SPIKEVAXa 1 month apart | 15,184
Study 1; (NCT04470427) | 18 years of age and older | First Booster Dose: Single dose (50 mcg mRNA) of SPIKEVAXa | 19,609b
Study 2; (NCT04405076) | 18 years of age and older | First Booster Dose: Single dose (50 mcg mRNA) of SPIKEVAXa | 171
Study 3; (NCT04649151) | 12 years through 17 years of age | Primary Series: 2 doses (100 mcg mRNA per dose) of SPIKEVAXa 1 month apart | 2,486
Study 3; (NCT04649151) | 12 years through 17 years of age | First Booster Dose: Single dose (50 mcg mRNA) of SPIKEVAXa | 1,405
Study 3; (NCT04649151) | 12 years through 17 years of age | Single Dose: 50 mcg mRNA of Moderna COVID-19 Vaccine, Bivalent (Original and Omicron BA.4/BA.5)c | 379
Study 4; (NCT04796896) | 6 years through 11 years of age | Primary Series: 2 doses (50 mcg mRNA per dose) of SPIKEVAXa 1 month apart | 3,708
Study 4; (NCT04796896) | 6 years through 11 years of age | First Booster Dose: Single dose (25 mcg mRNA) of SPIKEVAXa | 2,290
Study 4; (NCT04796896) | 2 years through 5 years of age | Primary Series: 2 doses (25 mcg mRNA per dose) of SPIKEVAXa 1 month apart | 3,671
Study 4; (NCT04796896) | 2 years through 5 years of age | First Booster Dose: Single dose (10 mcg mRNA) of bivalent vaccine (Original and Omicron BA.1)d | 1,514
Study 4; (NCT04796896) | 6 months through 23 months of age | Primary Series: 2 doses (25 mcg mRNA per dose) of SPIKEVAXa 1 month apart | 2,438
Study 4; (NCT04796896) | 6 months through 23 months of age | First Booster Dose: Single dose (10 mcg mRNA) of bivalent vaccine (Original and Omicron BA.1)d | 1,252
Study 5; (NCT04927065) | 18 years of age and older | Second Booster Dose: Single dose (50 mcg mRNA) of Moderna COVID-19 Vaccine, Bivalent (Original and Omicron BA.4/BA.5)c | 511
Study 6; (NCT05436834) | 2 years through 5 years of age | Primary Series: 2 doses (25 mcg mRNA per dose) of bivalent vaccine (Original and Omicron BA.1)d 1 month apart | 261
Study 6; (NCT05436834) | 2 years through 5 years of age | First Booster Dose: Single dose (10 mcg mRNA) of bivalent vaccine (Original and Omicron BA.1)d | 425
Study 6; (NCT05436834) | 2 years through 4 years of age | Single Dose: 25 mcg mRNA of SPIKEVAX (2023-2024 Formula)e | 199
Study 6; (NCT05436834) | 6 months through 23 months of age | Primary Series: 2 doses (25 mcg mRNA per dose) of bivalent vaccine (Original and Omicron BA.1)d 1 month apart | 130
Study 6; (NCT05436834) | 6 months through 23 months of age | Primary Series: 2 doses (25 mcg mRNA per dose) of SPIKEVAX (2023-2024 Formula)e 1 month apart | 399
Study 6; (NCT05436834) | 6 months through 23 months of age | First Booster Dose: Single dose (10 mcg mRNA) of bivalent vaccine (Original and Omicron BA.1)d | 114
a Vaccine encoding the viral spike (S) glycoprotein of SARS-CoV-2 Wuhan-Hu 1 strain (Original).
b Includes 10 participants who received a dose of SPIKEVAX (50 mcg mRNA) without having received a primary series of SPIKEVAX.
c Vaccine encoding the viral spike (S) glycoprotein of SARS-CoV-2 Wuhan-Hu 1 strain (Original) and Omicron variant lineages BA.4 and BA.5 (Omicron BA.4/BA.5).
d Vaccine encoding the viral spike (S) glycoprotein of SARS-CoV-2 Wuhan-Hu 1 strain (Original) and Omicron variant lineage BA.1.
e Vaccine encoding the viral spike (S) glycoprotein of SARS-CoV-2 Omicron variant lineage XBB.1.5.

Most commonly (≥10%) reported adverse reactions following administration of SPIKEVAX, Moderna COVID-19 Vaccine, Bivalent (Original and Omicron BA.4/BA.5) (hereafter referred to as Moderna COVID-19 Vaccine, Bivalent and no longer authorized for use in the U.S.) or bivalent vaccine (Original and Omicron BA.1) (not authorized for use in the U.S.) containing the same amount of mRNA as the SPIKEVAX 2025-2026 Formula:

- Participants 6 months through 36 months of age: irritability/crying (up to 82.8%), pain at the injection site (up to 77.2%), sleepiness (up to 52.2%), loss of appetite (up to 46.5%), fever (up to 26.8%), erythema (up to 19.2%), swelling at the injection site (up to 19.2%), and axillary (or groin) swelling/tenderness (up to 12.2%).
- Participants 37 months through 11 years of age: pain at the injection site (up to 98.4%), fatigue (up to 73.2%), headache (up to 62.2%), myalgia (up to 35.3%), chills (up to 34.6%), nausea/vomiting (up to 29.3%), axillary (or groin) swelling/tenderness (up to 27.0%), fever (up to 25.8%), erythema (up to 24.1%), swelling at the injection site (up to 22.3%), and arthralgia (up to 21.3%).
- Participants 12 years through 17 years of age: pain at the injection site (up to 90.6%), fatigue (up to 58.1%), headache (up to 56.3%), myalgia (up to 40.1%), chills (up to 30.2%), axillary swelling/tenderness (up to 27.8%), arthralgia (up to 23.9%), nausea/vomiting (up to 17.9%), and swelling at the injection site (up to 13.3%).
- Participants 18 years through 64 years of age: pain at injection site (up to 86.3%), fatigue (up to 62.0%), headache (up to 58.9%), myalgia (up to 49.6%), arthralgia (up to 41.9%), chills (up to 40.3%), axillary swelling/tenderness (up to 24.8%), and nausea/vomiting (up to 16.7%).
- Participants 65 years of age and older: pain at injection site (up to 76.3%), fatigue (up to 58.1%), myalgia (up to 47.4%), headache (up to 42.1%), arthralgia (up to 39.5%), chills (up to 18.4%), and axillary swelling/tenderness (up to 14.3%).

6.1 Clinical Trials Experience

Because clinical trials are conducted under widely varying conditions, adverse reaction rates observed in the clinical trials of a vaccine cannot be directly compared with rates in the clinical trials of another vaccine and may not reflect the rates observed in practice.

Adults 18 Years of Age and Older

2-Dose Series (Original Monovalent) in Vaccine-Naïve Adults (Study 1)

Study 1 was a Phase 3 clinical trial with multiple parts to evaluate the safety, reactogenicity, and immunogenicity of SPIKEVAX in participants 18 years of age and older (NCT04470427). The randomized, placebo-controlled, observer-blind phase of the trial was conducted in the United States involving 30,346 participants 18 years of age and older who received at least one dose of SPIKEVAX (100 mcg mRNA; n=15,184) or placebo (n=15,162). Upon issuance of the Emergency Use Authorization (December 18, 2020) for Moderna COVID-19 Vaccine (SPIKEVAX), participants were unblinded in a phased manner over a period of months to offer placebo participants SPIKEVAX. The median duration of follow-up for safety after the second injection during the blinded phase was 4 months. The median duration of follow-up for safety after the second injection including both the blinded phase and the open-label phase was 6 months.

In Study 1, the median age of the population was 52 years (range 18-95); 75.2% of participants were 18 years through 64 years of age and 24.8% were 65 years of age and older. Overall, 52.6% of the participants were male, 47.4% were female, 20.5% were Hispanic or Latino, 79.2% were White, 10.2% were African American, 4.6% were Asian, 0.8% were American Indian or Alaska Native, 0.2% were Native Hawaiian or Pacific Islander, 2.0% were other races, and 2.1% were Multiracial. Demographic characteristics were similar between participants who received SPIKEVAX and those who received placebo.

Solicited Adverse Reactions

Local and systemic adverse reactions and use of antipyretic medication were solicited in an electronic diary for 7 days following each injection (i.e., day of vaccination and the next 6 days) among participants receiving SPIKEVAX (n=15,179) and participants receiving placebo (n=15,159) with at least 1 documented dose. Events that persisted for more than 7 days were followed until resolution. Solicited adverse reactions were reported more frequently among vaccine participants than placebo participants.

The reported number and percentage of the solicited local and systemic adverse reactions by age group and dose are presented in Table 4 and Table 5, respectively.

Table 4: Number and Percentage of Participants with Solicited Local and Systemic Adverse Reactions Starting Within 7 Days* After Each Dose in Participants 18 Years Through 64 Years (Solicited Safety Set, Dose 1 and Dose 2)
 | SPIKEVAX |  | Placeboa
 | Dose 1; (N=11,406); n (%) | Dose 2; (N=11,000); n (%) | Dose 1; (N=11,402); n (%) | Dose 2; (N=10,929); n (%)
Local Adverse Reactions
Pain | 9,908; (86.9) | 9,893; (89.9) | 2,183; (19.1) | 2,048; (18.7)
Pain, Grade 3b | 366; (3.2) | 506; (4.6) | 23; (0.2) | 22; (0.2)
Axillary swelling/tenderness | 1,322; (11.6) | 1,777; (16.2) | 567; (5.0) | 474; (4.3)
Axillary swelling/tenderness, Grade 3b | 37; (0.3) | 47; (0.4) | 13; (0.1) | 12; (0.1)
Swelling (hardness); ≥25 mm | 766; (6.7) | 1,399; (12.7) | 42; (0.4) | 46; (0.4)
Swelling (hardness), Grade 3c | 62; (0.5) | 183; (1.7) | 3; (<0.1) | 5; (<0.1)
Erythema (redness); ≥25 mm | 354; (3.1) | 989; (9.0) | 54; (0.5) | 53; (0.5)
Erythema (redness), Grade 3c | 34; (0.3) | 210; (1.9) | 11; (<0.1) | 12; (0.1)
Systemic Adverse Reactions
Fatigue | 4,385; (38.5) | 7,453; (67.8) | 3,281; (28.8) | 2,701; (24.7)
Fatigue, Grade 3d | 121; (1.1) | 1,178; (10.7) | 83; (0.7) | 88; (0.8)
Fatigue, Grade 4e | 1; (<0.1) | 0; (0) | 0; (0) | 0; (0)
Headache | 4,028; (35.3) | 6,929; (63.0) | 3,303; (29.0) | 2,775; (25.4)
Headache, Grade 3f | 220; (1.9) | 559; (5.1) | 163; (1.4) | 132; (1.2)
Myalgia | 2,700; (23.7) | 6,789; (61.7) | 1,625; (14.3) | 1,425; (13.0)
Myalgia, Grade 3d | 74; (0.6) | 1,116; (10.1) | 38; (0.3) | 42; (0.4)
Arthralgia | 1,892; (16.6) | 5,010; (45.6) | 1,327; (11.6) | 1,180; (10.8)
Arthralgia, Grade 3d | 47; (0.4) | 650; (5.9) | 30; (0.3) | 37; (0.3)
Arthralgia, Grade 4e | 1; (<0.1) | 0; (0) | 0; (0) | 0; (0)
Chills | 1,050; (9.2) | 5,357; (48.7) | 730; (6.4) | 662; (6.1)
Chills, Grade 3g | 17; (0.1) | 164; (1.5) | 8; (<0.1) | 15; (0.1)
Nausea/vomiting | 1,068; (9.4) | 2,355; (21.4) | 908; (8.0) | 807; (7.4)
Nausea/vomiting,; Grade 3h | 6; (<0.1) | 11; (0.1) | 8; (<0.1) | 8; (<0.1)
Fever | 102; (0.9) | 1,909; (17.4) | 37; (0.3) | 38; (0.3)
Fever, Grade 3i | 10; (<0.1) | 185; (1.7) | 1; (<0.1) | 2; (<0.1)
Fever, Grade 4j | 4; (<0.1) | 12; (0.1) | 4; (<0.1) | 2; (<0.1)
Use of antipyretic or pain medication | 2,656; (23.3) | 6,307; (57.3) | 1,523; (13.4) | 1,254; (11.5)
* 7 days included day of vaccination and the subsequent 6 days. Events and use of antipyretic or pain medication were collected in the electronic diary (e-diary).
a Placebo was a saline solution.
b Grade 3 pain and axillary swelling/tenderness: Defined as any use of prescription pain reliever; prevents daily activity.
c Grade 3 swelling and erythema: Defined as >100 mm / >10 cm.
d Grade 3 fatigue, myalgia, arthralgia: Defined as significant; prevents daily activity.
e Grade 4 fatigue, arthralgia: Defined as requires emergency room visit or hospitalization.
f Grade 3 headache: Defined as significant; any use of prescription pain reliever or prevents daily activity.
g Grade 3 chills: Defined as prevents daily activity and requires medical intervention.
h Grade 3 nausea/vomiting: Defined as prevents daily activity; requires outpatient intravenous hydration.
i Grade 3 fever: Defined as ≥39.0° – ≤40.0°C / ≥102.1° – ≤104.0°F.
j Grade 4 fever: Defined as >40.0°C / >104.0°F.

Table 5: Number and Percentage of Participants with Solicited Local and Systemic Adverse Reactions Starting Within 7 Days* After Each Dose in Participants 65 Years and Older (Solicited Safety Set, Dose 1 and Dose 2)
 | SPIKEVAX |  | Placeboa
 | Dose 1; (N=3,760); n (%) | Dose 2; (N=3,691); n (%) | Dose 1; (N=3,749); n (%) | Dose 2; (N=3,649); n (%)
Local Adverse Reactions
Pain | 2,780; (73.9) | 3,071; (83.2) | 482; (12.9) | 438; (12.0)
Pain, Grade 3b | 50; (1.3) | 100; (2.7) | 32; (0.9) | 19; (0.5)
Axillary swelling/tenderness | 231; (6.1) | 315; (8.5) | 155; (4.1) | 97; (2.7)
Axillary swelling/tenderness, Grade 3b | 12; (0.3) | 21; (0.6) | 14; (0.4) | 8; (0.2)
Swelling (hardness); ≥25 mm | 169; (4.5) | 408; (11.1) | 23; (0.6) | 14; (0.4)
Swelling (hardness), Grade 3c | 20; (0.5) | 72; (2.0) | 3; (<0.1) | 7; (0.2)
Erythema (redness); ≥25 mm | 91; (2.4) | 285; (7.7) | 23; (0.6) | 15; (0.4)
Erythema (redness), Grade 3c | 8; (0.2) | 77; (2.1) | 2; (<0.1) | 3; (<0.1)
Systemic Adverse Reactions
Fatigue | 1,251; (33.3) | 2,154; (58.4) | 852; (22.7) | 717; (19.6)
Fatigue, Grade 3d | 30; (0.8) | 255; (6.9) | 22; (0.6) | 20; (0.5)
Headache | 922; (24.5) | 1,708; (46.3) | 723; (19.3) | 652; (17.9)
Headache, Grade 3e | 53; (1.4) | 107; (2.9) | 34; (0.9) | 33; (0.9)
Myalgia | 742; (19.7) | 1,740; (47.2) | 444; (11.9) | 399; (10.9)
Myalgia, Grade 3d | 17; (0.5) | 205; (5.6) | 9; (0.2) | 10; (0.3)
Arthralgia | 618; (16.4) | 1,293; (35.1) | 457; (12.2) | 399; (10.9)
Arthralgia, Grade 3d | 13; (0.3) | 125; (3.4) | 8; (0.2) | 7; (0.2)
Chills | 201; (5.3) | 1,143; (31.0) | 148; (4.0) | 151; (4.1)
Chills, Grade 3f | 7; (0.2) | 27; (0.7) | 6; (0.2) | 2; (<0.1)
Nausea/vomiting | 194; (5.2) | 439; (11.9) | 167; (4.5) | 134; (3.7)
Nausea/vomiting,; Grade 3g | 4; (0.1) | 10; (0.3) | 5; (0.1) | 3; (<0.1)
Nausea/vomiting,; Grade 4h | 0; (0) | 1; (<0.1) | 0; (0) | 0; (0)
Fever | 10; (0.3) | 367; (9.9) | 7; (0.2) | 5; (0.1)
Fever, Grade 3i | 1; (<0.1) | 18; (0.5) | 1; (<0.1) | 0; (0)
Fever, Grade 4j | 0; (0) | 1; (<0.1) | 2; (<0.1) | 1; (<0.1)
Use of antipyretic or pain medication | 673; (17.9) | 1,548; (41.9) | 477; (12.7) | 331; (9.1)
* 7 days included day of vaccination and the subsequent 6 days. Events and use of antipyretic or pain medication were collected in the electronic diary (e-diary).
a Placebo was a saline solution.
b Grade 3 pain and axillary swelling/tenderness: Defined as any use of prescription pain reliever; prevents daily activity.
c Grade 3 swelling and erythema: Defined as >100 mm / >10 cm.
d Grade 3 fatigue, myalgia, arthralgia: Defined as significant; prevents daily activity.
e Grade 3 headache: Defined as significant; any use of prescription pain reliever or prevents daily activity.
f Grade 3 chills: Defined as prevents daily activity and requires medical intervention.
g Grade 3 nausea/vomiting: Defined as prevents daily activity; requires outpatient intravenous hydration.
h Grade 4 nausea/vomiting: Defined as requires emergency room visit or hospitalization for hypotensive shock.
i Grade 3 fever: Defined as ≥39.0° – ≤40.0°C / ≥102.1° – ≤104.0°F.
j Grade 4 fever: Defined as >40.0°C / >104.0°F.

Solicited local and systemic adverse reactions reported following administration of SPIKEVAX had a median duration of 1 to 3 days.

Grade 3 solicited local adverse reactions were more frequently reported after Dose 2 than after Dose 1. Solicited systemic adverse reactions were more frequently reported by vaccine recipients after Dose 2 than after Dose 1.

In Study 1, 2.3% of participants (vaccine=347, placebo=337) had evidence of prior SARS-CoV-2 infection at baseline (immunologic or virologic evidence of prior SARS-CoV-2 infection [defined as positive RT-PCR test and/or positive Elecsys immunoassay result at Day 1]). Overall, among the 347 vaccine participants, there were no notable differences in reactogenicity compared to the 14,750 vaccine participants who had no evidence of prior SARS-CoV-2 infection at baseline (negative RT-PCR test and negative Elecsys immunoassay result at Day 1).

Unsolicited Adverse Events

Participants were monitored for unsolicited adverse events for 28 days following each dose. Serious adverse events and medically attended adverse events were recorded for the entire study duration (2 years). Among the 30,346 participants who had received at least 1 dose of vaccine (N=15,184) or placebo (N=15,162), unsolicited adverse events that occurred within 28 days following any vaccination were reported by 31.3% of participants (n=4,752) who received SPIKEVAX and 28.6% of participants (n=4,338) who received placebo.

During the 28-day follow-up period following any dose, lymphadenopathy-related events were reported by 1.7% of vaccine recipients and 0.8% of placebo recipients. These events included lymphadenopathy, lymphadenitis, lymph node pain, vaccination-site lymphadenopathy, injection-site lymphadenopathy, and axillary mass. This imbalance is consistent with the imbalance observed for solicited axillary swelling/tenderness at the injected arm.

During the 7-day follow-up period of any vaccination, hypersensitivity events of injection site rash or injection site urticaria, likely related to vaccination, were reported by 6 participants in the SPIKEVAX group and none in the placebo group. Delayed injection site reactions that began >7 days after vaccination were reported in 1.4% of vaccine recipients and 0.7% of placebo recipients. Delayed injection site reactions included pain, erythema, and swelling and are likely related to vaccination.

In the blinded portion of the study, there were 8 reports of facial paralysis (including Bell’s palsy) in the SPIKEVAX group, and 3 in the placebo group. In the 28-day follow-up period there were two cases of facial paralysis in the SPIKEVAX group, which occurred on 8 and 22 days, respectively, after vaccination, and one in the placebo group, which occurred 17 days after vaccination. Currently available information on facial paralysis is insufficient to determine a causal relationship with the vaccine.

In the blinded portion of the study, there were 50 reports of herpes zoster in the SPIKEVAX group and 23 in the placebo group. In the 28-day period after any vaccination, there were 22 cases of herpes zoster in the SPIKEVAX group and 15 in the placebo group. Currently available information on herpes zoster infection is insufficient to determine a causal relationship with the vaccine.

There were no other notable patterns or numerical imbalances between treatment groups for specific categories of adverse events (including other neurologic, neuro-inflammatory, and thrombotic events) that would suggest a causal relationship to SPIKEVAX.

Serious Adverse Events

During the blinded phase of the study, serious adverse events were reported by 1.8% (n=268) of participants who received SPIKEVAX and 1.9% (n=292) of participants who received placebo.

There were three serious adverse events of angioedema/facial swelling in the vaccine group in recipients with a history of injection of dermatological fillers. The onset of swelling was reported 1-2 days after the second dose and was likely related to vaccination.

There were no other notable patterns or imbalances between treatment groups for specific categories of serious adverse events (including neurologic, neuro-inflammatory, and thrombotic events) that would suggest a causal relationship to SPIKEVAX.

Single Dose (Original Monovalent) in Vaccine-Experienced Adults (Study 2)

Study 2 was a Phase 2, randomized, observer-blind, placebo-controlled, dose-confirmation study to evaluate the safety, reactogenicity, and immunogenicity of SPIKEVAX in participants 18 years of age and older (NCT04405076). In this study, 198 participants received two doses 1 month apart of SPIKEVAX primary series (100 mcg mRNA per dose). In an open-label phase of the study, 171 of those participants received a single booster dose (50 mcg mRNA) at least 6 months (range 5.8-8.5) after receiving the second dose of the primary series.

Among the 171 booster dose recipients, the median age was 55 years (range 18-87); 77.8% of participants were 18 years through 64 years of age, 22.2% were 65 years of age and older, 39.2% were male, 60.8% were female, 5.8% were Hispanic or Latino, 95.9% were White, 2.9% were African American, 0.6% were Asian, and 0.6% were American Indian or Alaska Native.

Solicited Adverse Reactions

Solicited local and systemic adverse reactions in participants 18 years through 64 years of age starting within 7 days after administration of a booster dose included pain at the injection site (86.0%), fatigue (62.0%), headache (58.9%), myalgia (49.6%), arthralgia (41.9%), chills (40.3%), axillary swelling/tenderness (24.8%), nausea/vomiting (12.4%), fever (7.0%), swelling at the injection site (6.2%), erythema at the injection site (5.4%), and rash (2.3%).

Solicited local and systemic adverse reactions in participants 65 years of age and older starting within 7 days after administration of a booster dose included pain at the injection site (76.3%), fatigue (47.4%), myalgia (47.4%), headache (42.1%), arthralgia (39.5%), chills (18.4%), nausea/vomiting (7.9%), fever (5.4%), axillary swelling/tenderness (5.3%), erythema at the injection site (2.6%), and swelling at the injection site (2.6%).

No Grade 4 adverse reactions were reported. The median duration of solicited local and systemic adverse reactions was 2 to 3 days.

Unsolicited Adverse Events

Overall, the 171 participants who received a booster dose had a median follow-up time of 176 days after the booster dose to the database lock date (November 23, 2021). Through 28 days after the booster dose, unsolicited adverse events were reported by 14.6% of participants (n=25) after the booster dose. There were no unsolicited adverse events not already captured by solicited local and systemic reactions that were considered causally related to SPIKEVAX.

Serious Adverse Events

There were no serious adverse events reported from the booster dose through 28 days after the booster dose. Through the database lock date (November 23, 2021), there were no serious adverse events following the booster dose considered causally related to SPIKEVAX.

Single Dose (Original Monovalent) in Vaccine-Experienced Adults (Study 1)

Study 1 was a Phase 3 clinical trial with multiple parts to evaluate the safety, reactogenicity, and immunogenicity of SPIKEVAX in participants 18 years of age and older (NCT04470427). In the open-label booster dose phase of this study, 19,609 participants received a single booster dose of SPIKEVAX (50 mcg mRNA). Of these participants, 19,599 had previously received a primary series of SPIKEVAX and received a single booster dose at least 6 months (range 5-19) after receiving the second dose of the primary series.

Among the 19,609 booster dose recipients, the median age was 55 years (range 19-96); 69.6% of participants were 18 years through 64 years of age, 30.4% were 65 years of age and older, 52.4% were male, 47.6% were female, 20.2% were Hispanic or Latino, 78.9% were White, 10.6% were African American, 4.1% were Asian, 0.8% were American Indian or Alaska Native, 0.2% were Native Hawaiian or Pacific Islander, 2.0% were other races, and 2.2% were Multiracial. After October 1, 2021, cases of potential myocarditis and/or pericarditis that were identified by the investigator or Applicant were adjudicated by an independent CEAC to determine if they met the CDC definition of confirmed or probable myocarditis and/or pericarditis. In these analyses, the median follow-up time after the booster dose through the cutoff date (April 5, 2022) was 161 days and 3,361 study participants who received the booster dose (17.1%) had at least 6 months of follow-up.

Unsolicited Adverse Events

Participants were monitored for unsolicited adverse events for up to 28 days following the booster dose. As of the cutoff date (April 5, 2022), among the 19,609 participants who had received a booster dose, unsolicited adverse events that occurred within 28 days after the booster were reported by 31.7% of participants (n=6,209). The safety profile for the booster dose of SPIKEVAX was similar to the safety profile of the SPIKEVAX primary series in this population.

Serious Adverse Events

Serious adverse events through 28 days following the booster dose of SPIKEVAX were reported by 0.5% of participants (n=94). Through the cutoff date (April 5, 2022), 2.3% of participants (n=442) reported serious adverse events following the booster dose.

A 42-year-old male experienced probable myocarditis (per CEAC adjudication) with onset of symptoms the same day following receipt of the booster dose of SPIKEVAX. Myocarditis was reported as resolved without sequelae on Day 72. This event was considered related to SPIKEVAX.

There was one serious adverse event of erythema nodosum 8 days after the booster dose in a 73-year-old female. This event was considered causally related to SPIKEVAX and was reported as resolved without treatment on Day 30.

Single Dose (Bivalent Original and Omicron BA.4/BA.5) in Vaccine-Experienced Adults (Study 5)

Study 5 (NCT04927065), a Phase 2/3 open-label study with multiple parts conducted in the United States, evaluated the immunogenicity, safety, and reactogenicity of a second booster dose of Moderna COVID-19 Vaccine, Bivalent (50 mcg mRNA) compared to a second booster dose of SPIKEVAX (50 mcg mRNA) when administered to participants 18 years of age and older who had previously received a primary series and a first booster dose with SPIKEVAX at least 3 months prior. The safety analysis set included 511 participants in the Moderna COVID-19 Vaccine, Bivalent booster dose group and 376 participants in the SPIKEVAX booster dose group.

For the Moderna COVID-19 Vaccine, Bivalent group, the median age of the population was 50 years (range 19-89); 79.5% of participants were 18 years through 64 years of age and 20.5% were 65 years of age and older. Overall, 38.2% were male, 61.8% were female, 11.4% were Hispanic or Latino, 83.4% were White, 11.0% were African American, 2.2% were Asian, 0.2% were American Indian or Alaska Native, 1.2% were other races, and 1.6% were Multiracial. For the SPIKEVAX group, the median age of the population was 61 years (range 20-96); 60.1% of participants were 18 years through 64 years of age and 39.9% were 65 years of age and older. Overall, 49.5% were male, 50.5% were female, 9.8% were Hispanic or Latino, 85.6% were White, 7.4% were African American, 4.3% were Asian, 0.3% were American Indian or Alaska Native, 0.3% were Native Hawaiian or Pacific Islander, 0.5% were other races, and 0.5% were Multiracial.

In these analyses, the median follow-up time after the booster dose through the cutoff date (September 23, 2022) for the Moderna COVID-19 Vaccine, Bivalent recipients was 37 days. The median follow-up time after the booster dose through the cutoff date (July 6, 2022) for the SPIKEVAX recipients was 127 days.

Solicited Adverse Reactions

Local and systemic adverse reactions and use of antipyretic medication were solicited in an electronic diary for 7 days following the injection (i.e., day of vaccination and the next 6 days) among participants receiving Moderna COVID-19 Vaccine, Bivalent and participants receiving SPIKEVAX. Events that persisted for more than 7 days were followed until resolution.

Table 6 and Table 7 present the frequency and severity of reported solicited local and systemic adverse reactions within 7 days following a second booster dose with Moderna COVID-19 Vaccine, Bivalent compared to SPIKEVAX in participants 18 years through 64 years of age and 65 years of age and older.

Table 6: Number and Percentage of Participants 18 Years Through 64 Years of Age with Solicited Local and Systemic Adverse Reactions Starting Within 7 Days* After a Second Booster Dose with Moderna COVID-19 Vaccine, Bivalent Compared to a Second Booster Dose with SPIKEVAX (Solicited Safety Set)†
 | Moderna COVID-19; Vaccine, Bivalent; Booster Dose; N=402-403; n (%) | SPIKEVAX; Booster Dose; N=210; n (%)
Local Adverse Reactions
Pain | 347 (86.3) | 174 (82.9)
Pain, Grade 3a | 19 (4.7) | 4 (1.9)
Axillary swelling/tenderness | 91 (22.6) | 38 (18.1)
Axillary swelling/tenderness, Grade 3a | 1 (0.2) | 4 (1.9)
Swelling (hardness) ≥25 mm | 32 (8.0) | 14 (6.7)
Swelling (hardness), Grade 3b | 2 (0.5) | 2 (1.0)
Erythema (redness) ≥25 mm | 17 (4.2) | 10 (4.8)
Erythema (redness), Grade 3b | 3 (0.7) | 1 (0.5)
Systemic Adverse Reactions
Fatigue | 243 (60.3) | 114 (54.3)
Fatigue, Grade 3c | 14 (3.5) | 7 (3.3)
Headache | 210 (52.2) | 99 (47.1)
Headache, Grade 3d | 11 (2.7) | 1 (0.5)
Myalgia | 197 (49.0) | 89 (42.4)
Myalgia, Grade 3c | 17 (4.2) | 8 (3.8)
Arthralgia | 145 (36.1) | 68 (32.4)
Arthralgia, Grade 3c | 9 (2.2) | 2 (1.0)
Chills | 96 (23.9) | 54 (25.7)
Chills, Grade 3e | 3 (0.7) | 0 (0)
Nausea/vomiting | 67 (16.7) | 27 (12.9)
Nausea/vomiting, Grade 3f | 1 (0.2) | 0 (0)
Fever | 16 (4.0) | 9 (4.3)
Fever, Grade 3g | 1 (0.2) | 0 (0)
Use of antipyretic or pain medicationh | 159 (39.5) | 67 (31.9)
* 7 days included day of vaccination and the subsequent 6 days. Events and use of antipyretic or pain medication were collected in the electronic diary (e-diary). Solicited Safety Set consisted of participants who received a booster dose and contributed solicited adverse reaction data.
† Absence of rows for Grade 4 adverse reactions indicates no events were reported.
N=Number of participants in the Solicited Safety Set who had available data for the solicited adverse reactions.
a Grade 3 pain and axillary swelling/tenderness: Defined as any use of prescription pain reliever; prevents daily activity.
b Grade 3 swelling and erythema: Defined as >100 mm / >10 cm.
c Grade 3 fatigue, myalgia, arthralgia: Defined as significant; prevents daily activity.
d Grade 3 headache: Defined as significant; any use of prescription pain reliever or prevents daily activity.
e Grade 3 chills: Defined as prevents daily activity and requires medical intervention.
f Grade 3 nausea/vomiting: Defined as prevents daily activity; requires outpatient intravenous hydration.
g Grade 3 fever: Defined as ≥39.0° – ≤40.0°C / ≥102.1° – ≤104.0°F.
h Percentage based on participants in the Solicited Safety Set (N=403 for Moderna COVID-19 Vaccine, Bivalent and N=210 for SPIKEVAX).

Table 7: Number and Percentage of Participants 65 Years of Age and Older with Solicited Local and Systemic Adverse Reactions Starting Within 7 Days* After a Second Booster Dose with Moderna COVID-19 Vaccine, Bivalent Compared to a Second Booster Dose with SPIKEVAX (Solicited Safety Set)†
 | Moderna COVID-19; Vaccine, Bivalent; Booster Dose; N=105; n (%) | SPIKEVAX; Booster Dose; N=139-140; n (%)
Local Adverse Reactions
Pain | 71 (67.6) | 94 (67.1)
Pain, Grade 3a | 1 (1.0) | 0 (0)
Axillary swelling/tenderness | 15 (14.3) | 15 (10.7)
Swelling (hardness) ≥25 mm | 8 (7.6) | 8 (5.7)
Swelling (hardness), Grade 3b | 3 (2.9) | 3 (2.1)
Erythema (redness) ≥25 mm | 6 (5.7) | 3 (2.1)
Erythema (redness), Grade 3b | 2 (1.9) | 1 (0.7)
Systemic Adverse Reactions
Fatigue | 61 (58.1) | 65 (46.8)
Fatigue, Grade 3c | 3 (2.9) | 4 (2.9)
Headache | 39 (37.1) | 44 (31.7)
Headache, Grade 3d | 1 (1.0) | 1 (0.7)
Myalgia | 38 (36.2) | 45 (32.4)
Myalgia, Grade 3c | 3 (2.9) | 5 (3.6)
Arthralgia | 32 (30.5) | 42 (30.2)
Arthralgia, Grade 3c | 0 (0) | 1 (0.7)
Chills | 16 (15.2) | 20 (14.4)
Chills, Grade 3e | 1 (1.0) | 1 (0.7)
Nausea/vomiting | 4 (3.8) | 8 (5.8)
Fever | 4 (3.8) | 2 (1.4)
Use of antipyretic or pain medicationf | 38 (36.2) | 40 (28.6)
* 7 days included day of vaccination and the subsequent 6 days. Events and use of antipyretic or pain medication were collected in the electronic diary (e-diary). Solicited Safety Set consisted of participants who received a booster dose and contributed solicited adverse reaction data.
† Absence of rows for Grade 3 or Grade 4 adverse reactions indicates no events were reported.
N=Number of participants in the Solicited Safety Set who had available data for the solicited adverse reactions.
a Grade 3 pain: Defined as any use of prescription pain reliever; prevents daily activity.
b Grade 3 swelling and erythema: Defined as >100 mm / >10 cm.
c Grade 3 fatigue, myalgia, arthralgia: Defined as significant; prevents daily activity.
d Grade 3 headache: Defined as significant; any use of prescription pain reliever or prevents daily activity.
e Grade 3 chills: Defined as prevents daily activity and requires medical intervention.
f Percentage based on participants in the Solicited Safety Set (N=105 for Moderna COVID-19 Vaccine, Bivalent and N=140 for SPIKEVAX).

The median duration of solicited local and systemic adverse reactions was 3 days in participants who received either vaccine booster dose.

Unsolicited Adverse Events

Participants were monitored for unsolicited adverse events for up to 28 days following the booster dose. Serious adverse events and medically attended adverse events were recorded for the entire study duration. As of September 23, 2022, among participants who had received a booster dose of Moderna COVID-19 Vaccine, Bivalent (n=511), unsolicited adverse events that occurred within 28 days following vaccination were reported by 22.7% of participants (n=116). As of July 6, 2022, among participants who had received a booster dose of SPIKEVAX (n=376), unsolicited adverse events that occurred within 28 days following vaccination were reported by 21.3% of participants (n=80). In these analyses, 99.6% of study participants in the Moderna COVID-19 Vaccine, Bivalent group had at least 28 days of follow-up after the booster dose to the cutoff date (September 23, 2022) and 100.0% of participants in the SPIKEVAX group had at least 28 days of follow-up after the booster dose to the cutoff date (July 6, 2022). There were no notable differences in specific categories of adverse events that were reported between the vaccine groups.

Serious Adverse Events

As of the cutoff date (September 23, 2022), the median duration of follow-up was 37 days among Moderna COVID-19 Vaccine, Bivalent booster dose recipients. Serious adverse events were reported by 0.6% of participants (n=3) who received Moderna COVID-19 Vaccine, Bivalent. As of the cutoff date (July 6, 2022), the median duration of follow-up was 127 days among the SPIKEVAX booster dose recipients. Serious adverse events were reported by 2.7% of participants (n=10) who received SPIKEVAX. None of the events in either vaccine group were considered to be related to vaccine.

Adolescents 12 Years Through 17 Years of Age

2-Dose Series (Original Monovalent) in Vaccine-Naïve Adolescents (Study 3)

The safety of SPIKEVAX was evaluated in a Phase 3 clinical trial with multiple parts. The randomized, placebo-controlled, observer-blind clinical trial was conducted in the United States involving 3,726 participants 12 years through 17 years of age who received at least one dose of SPIKEVAX (100 mcg mRNA; n=2,486) or placebo (n=1,240) (Study 3, NCT04649151). Participants started to enter an open-label, observational phase after May 10, 2021. After October 1, 2021, cases of potential myocarditis and/or pericarditis that were identified by the investigator or Applicant were adjudicated by an independent Cardiac Event Adjudication Committee (CEAC) to determine if they met the CDC definition of confirmed or probable myocarditis and/or pericarditis. A safety analysis was conducted in participants who received SPIKEVAX (n=2,486) with a cutoff date of January 31, 2022. In these analyses, the median duration of follow-up including both the blinded and open-label phases was 312 days after Dose 2 and 95.7% of study participants had at least 6 months of follow-up after Dose 2.

Overall, 51.4% were male, 48.6% were female, 11.6% were Hispanic or Latino, 83.8% were White, 3.4% were African American, 6.0% were Asian, 0.5% were American Indian or Alaska Native, <0.1% were Native Hawaiian or Pacific Islander, 1.0% were other races, and 4.5% were Multiracial. Demographic characteristics were similar among participants who received SPIKEVAX and those who received placebo.

Solicited Adverse Reactions

Local and systemic adverse reactions and use of antipyretic medication were solicited in an electronic diary for 7 days following each injection (i.e., day of vaccination and the next 6 days) among participants receiving SPIKEVAX (n=2,485) and participants receiving placebo (n=1,240) with at least 1 documented dose. Events that persisted for more than 7 days were followed until resolution. Solicited adverse reactions were reported more frequently among vaccine participants than placebo participants.

The reported number and percentage of the solicited local and systemic adverse reactions in participants 12 years through 17 years of age by dose are presented in Table 8.

Table 8: Number and Percentage of Participants with Solicited Local and Systemic Adverse Reactions Starting Within 7 Days* After Each Dose in Participants 12 Years Through 17 Years (Solicited Safety Set, Dose 1 and Dose 2)†
 | SPIKEVAX |  | Placeboa
 | Dose 1; N=2,480-2,482; n (%) | Dose 2; N=2,477-2,478; n (%) | Dose 1; N=1,238; n (%) | Dose 2; N=1,219-1,220; n (%)
Local Adverse Reactions
Pain | 2,310; (93.1) | 2,290; (92.4) | 431; (34.8) | 370; (30.3)
Pain, Grade 3b | 133; (5.4) | 126; (5.1) | 1; (<0.1) | 3; (0.2)
Axillary swelling/tenderness | 576; (23.2) | 519; (21.0) | 101; (8.2) | 61; (5.0)
Axillary swelling/tenderness, Grade 3b | 11; (0.4) | 7; (0.3) | 0; (0) | 0; (0)
Swelling (hardness); ≥25 mm | 401; (16.2) | 508; (20.5) | 12; (1.0) | 12; (1.0)
Swelling (hardness), Grade 3c | 27; (1.1) | 56; (2.3) | 0; (0) | 0; (0)
Erythema (redness); ≥25 mm | 329; (13.3) | 484; (19.5) | 8; (0.6) | 11; (0.9)
Erythema (redness), Grade 3c | 22; (0.9) | 72; (2.9) | 0; (0) | 0; (0)
Systemic Adverse Reactions
Fatigue | 1,188; (47.9) | 1,679; (67.8) | 453; (36.6) | 353; (28.9)
Fatigue, Grade 3d | 33; (1.3) | 188; (7.6) | 18; (1.5) | 10; (0.8)
Headache | 1,106; (44.6) | 1,739; (70.2) | 477; (38.5) | 371; (30.4)
Headache, Grade 3e | 56; (2.3) | 112; (4.5) | 17; (1.4) | 14; (1.1)
Headache, Grade 4f | 0; (0) | 1; (<0.1) | 0; (0) | 0; (0)
Myalgia | 670; (27.0) | 1,155; (46.6) | 205; (16.6) | 153; (12.5)
Myalgia, Grade 3d | 24; (1.0) | 129; (5.2) | 10; (0.8) | 3; (0.2)
Arthralgia | 371; (15.0) | 716; (28.9) | 143; (11.6) | 113; (9.3)
Arthralgia, Grade 3d | 15; (0.6) | 57; (2.3) | 5; (0.4) | 2; (0.2)
Chills | 456; (18.4) | 1,066; (43.0) | 138; (11.1) | 97; (8.0)
Chills, Grade 3g | 4; (0.2) | 11; (0.4) | 1; (<0.1) | 0; (0)
Nausea/vomiting | 281; (11.3) | 591; (23.9) | 109; (8.8) | 106; (8.7)
Nausea/vomiting,; Grade 3h | 2; (<0.1) | 2; (<0.1) | 0; (0) | 0; (0)
Nausea/vomiting, Grade 4i | 0; (0) | 1; (<0.1) | 0; (0) | 0; (0)
Fever | 57; (2.3) | 298; (12.0) | 11; (0.9) | 12; (1.0)
Fever, Grade 3j | 9; (0.4) | 48; (1.9) | 1; (<0.1) | 1; (<0.1)
Fever, Grade 4k | 0; (0) | 1; (<0.1) | 0; (0) | 1; (<0.1)
Use of antipyretic or pain medicationl | 748; (30.1) | 1,242; (50.1) | 118; (9.5) | 108; (8.9)
* 7 days included day of vaccination and the subsequent 6 days. Events and use of antipyretic or pain medication were collected in the electronic diary (e-diary).
† Absence of rows for Grade 4 adverse reactions indicates no events were reported.
N=Number of participants in the Solicited Safety Set who had available data for the solicited adverse reactions.
a Placebo was a saline solution.
b Grade 3 pain and axillary swelling/tenderness: Defined as any use of prescription pain reliever; prevents daily activity.
c Grade 3 swelling and erythema: Defined as >100 mm / >10 cm.
d Grade 3 fatigue, myalgia, arthralgia: Defined as significant; prevents daily activity.
e Grade 3 headache: Defined as significant; any use of prescription pain reliever or prevents daily activity.
f Grade 4 headache: Defined as requires emergency room visit or hospitalization.
g Grade 3 chills: Defined as prevents daily activity and requires medical intervention.
h Grade 3 nausea/vomiting: Defined as prevents daily activity, requires outpatient intravenous hydration.
i Grade 4 nausea/vomiting: Defined as requires emergency room visit or hospitalization for hypotensive shock.
j Grade 3 fever: Defined as ≥39.0° – ≤40.0°C / ≥102.1° – ≤104.0°F.
k Grade 4 fever: Defined as >40.0°C / >104.0°F.
l Percentage based on participants in the Solicited Safety Set (2,482 post-Dose 1 and 2,478 post-Dose 2 for SPIKEVAX; 1,238 post-Dose 1 and 1,220 post-Dose 2 for placebo).

Solicited local and systemic adverse reactions reported following administration of SPIKEVAX had a median duration of 2 to 3 days.

In ages 12 years through 17 years, 5.8% of participants (vaccine=147, placebo=70) had evidence of prior SARS-CoV-2 infection at baseline (immunologic or virologic evidence of prior SARS-CoV-2 infection [defined as positive RT-PCR test and/or positive Elecsys immunoassay result at Day 1]). An assessment of reactogenicity among participants with evidence of prior SARS-CoV-2 infection compared to those with no evidence of infection at baseline (negative RT-PCR test and negative Elecsys immunoassay result at Day 1) was conducted. Table 9 presents the number and percentage of the solicited local and systemic adverse reactions in SPIKEVAX participants starting within 7 days after each dose by SARS-CoV-2 status.

Table 9: Number and Percentage of Participants 12 Years Through 17 Years Who Received SPIKEVAX with Solicited Local and Systemic Adverse Reactions Starting Within 7 Days* After Each Dose by SARS-CoV-2 Status (Solicited Safety Set, Dose 1 and Dose 2)†
 | Baseline SARS-CoV-2; Positive |  | Baseline SARS-CoV-2; Negative
 | Dose 1; N=147; n (%) | Dose 2; N=146; n (%) | Dose 1; N=2,165-2,167; n (%) | Dose 2; N=2,165-2,166; n (%)
Local Adverse Reactions
Pain | 128; (87.1) | 124; (84.9) | 2,027; (93.5) | 2,009; (92.8)
Pain, Grade 3a | 9; (6.1) | 7; (4.8) | 113; (5.2) | 114; (5.3)
Axillary swelling/tenderness | 58; (39.5) | 25; (17.1) | 485; (22.4) | 465; (21.5)
Axillary swelling/tenderness, Grade 3a | 1; (0.7) | 0; (0) | 10; (0.5) | 7; (0.3)
Swelling (hardness); ≥25 mm | 24; (16.3) | 22; (15.1) | 359; (16.6) | 448; (20.7)
Swelling (hardness), Grade 3b | 4; (2.7) | 2; (1.4) | 21; (1.0) | 50; (2.3)
Erythema (redness); ≥25 mm | 20; (13.6) | 18; (12.3) | 303; (14.0) | 432; (19.9)
Erythema (redness), Grade 3b | 1; (0.7) | 3; (2.1) | 20; (0.9) | 62; (2.9)
Systemic Adverse Reactions
Fatigue | 103; (70.1) | 94; (64.4) | 1,006; (46.4) | 1,471; (67.9)
Fatigue, Grade 3c | 4; (2.7) | 5; (3.4) | 27; (1.2) | 173; (8.0)
Headache | 103; (70.1) | 90; (61.6) | 941; (43.5) | 1,528; (70.5)
Headache, Grade 3d | 11; (7.5) | 7; (4.8) | 44; (2.0) | 96; (4.4)
Headache, Grade 4e | 0; (0) | 0; (0) | 0; (0) | 1; (<0.1)
Myalgia | 63; (42.9) | 63; (43.2) | 559; (25.8) | 1,019; (47.1)
Myalgia, Grade 3c | 3; (2.0) | 2; (1.4) | 19; (0.9) | 117; (5.4)
Arthralgia | 36; (24.5) | 39; (26.7) | 306; (14.1) | 634; (29.3)
Arthralgia, Grade 3c | 2; (1.4) | 0; (0) | 12; (0.6) | 52; (2.4)
Chills | 72; (49.0) | 63; (43.2) | 364; (16.8) | 935; (43.2)
Chills, Grade 3f | 0; (0) | 0; (0) | 4; (0.2) | 10; (0.5)
Nausea/vomiting | 30; (20.4) | 29; (19.9) | 237; (10.9) | 523; (24.2)
Nausea/vomiting,; Grade 3g | 0; (0) | 0; (0) | 2; (<0.1) | 2; (<0.1)
Nausea/vomiting,; Grade 4h | 0; (0) | 1; (0.7) | 0; (0) | 0; (0)
Fever | 28; (19.0) | 20; (13.7) | 28; (1.3) | 258; (11.9)
Fever, Grade 3i | 4; (2.7) | 2; (1.4) | 4; (0.2) | 42; (1.9)
Fever, Grade 4j | 0; (0) | 0; (0) | 0; (0) | 1; (<0.1)
* 7 days included day of vaccination and the subsequent 6 days. Events were collected in the electronic diary (e-diary).
† Absence of rows for Grade 4 adverse reactions indicates no events were reported.
N=Number of participants in the Solicited Safety Set who had available data for the solicited adverse reactions.
a Grade 3 pain and axillary swelling/tenderness: Defined as any use of prescription pain reliever; prevents daily activity.
b Grade 3 swelling and erythema: Defined as >100 mm / >10 cm.
c Grade 3 fatigue, myalgia, arthralgia: Defined as significant; prevents daily activity.
d Grade 3 headache: Defined as significant; any use of prescription pain reliever or prevents daily activity.
e Grade 4 headache: Defined as requires emergency room visit or hospitalization.
f Grade 3 chills: Defined as prevents daily activity and requires medical intervention.
g Grade 3 nausea/vomiting: Defined as prevents daily activity, requires outpatient intravenous hydration.
h Grade 4 nausea/vomiting: Defined as requires emergency room visit or hospitalization for hypotensive shock.
i Grade 3 fever: Defined as ≥39.0° – ≤40.0°C / ≥102.1° – ≤104.0°F.
j Grade 4 fever: Defined as >40.0°C / >104.0°F.

Unsolicited Adverse Events

Participants were monitored for unsolicited adverse events for 28 days following each dose. Serious adverse events and medically attended adverse events were recorded for the entire study duration. Among the 3,726 participants who had received at least 1 dose of vaccine (n=2,486) or placebo (n=1,240), unsolicited adverse events that occurred within 28 days following any vaccination were reported by 23.4% of participants (n=582) who received SPIKEVAX and 19.1% of participants (n=237) who received placebo.

In the open-label portion of the study, a 14-year-old male experienced probable myocarditis with onset of symptoms 1 day after Dose 2 of SPIKEVAX. Symptoms resolved after 8 days and no sequelae were observed at 5 months. This event was considered related to SPIKEVAX and was subsequently adjudicated by the CEAC as probable myocarditis. There were no cases of myocarditis among placebo recipients.

During the 28-day follow-up period following any dose, lymphadenopathy-related events were reported by 6.0% of vaccine recipients and 0.6% of placebo recipients. These events included lymphadenopathy, vaccination-site lymphadenopathy, and injection-site lymphadenopathy which were plausibly related to vaccination. This imbalance is consistent with the imbalance observed for solicited axillary swelling/tenderness in the injected arm.

During the 28-day follow-up period following any dose, hypersensitivity events of injection site rash or injection site urticaria, likely related to vaccination, were reported by 0.3% of participants in the SPIKEVAX group and <0.1% in the placebo group. Delayed injection site reactions that began >7 days after vaccination were reported in 1.5% of vaccine recipients and in <0.1% of placebo recipients. Delayed injection site reactions included pain, erythema, and swelling and are likely related to vaccination.

There were no other notable patterns or numerical imbalances between treatment groups for specific categories of adverse events (including other neurologic, neuro-inflammatory, and thrombotic events) that would suggest a causal relationship to SPIKEVAX.

Serious Adverse Events

During the blinded portion of the study, serious adverse events were reported by 0.4% (n=9) of participants who received SPIKEVAX and 0.2% (n=3) of participants who received placebo. In the open-label phase, an additional 12 SPIKEVAX recipients reported serious adverse events. There were no serious adverse events considered causally related to the vaccine.

There were no notable patterns or imbalances between treatment groups for specific categories of serious adverse events (including neurologic, neuro-inflammatory, and thrombotic events) that would suggest a causal relationship to SPIKEVAX.

Single Dose (Original Monovalent) in Vaccine-Experienced Adolescents (Study 3)

Safety data for a booster dose of SPIKEVAX in adolescents were collected in a Phase 3 clinical trial with multiple parts. The open-label booster portion of the study included 1,405 participants who were 12 years through 17 years of age at the time of first dose of the primary series and who received a booster dose of SPIKEVAX (50 mcg mRNA) at least 5 months (range 2.1-16.9) after the second dose of the primary series (Study 3, NCT04649151). Overall, 51.5% were male, 48.5% were female, 13.4% were Hispanic or Latino, 84.9% were White, 3.1% were African American, 4.9% were Asian, 0.5% were American Indian or Alaska Native, <0.1% were Native Hawaiian or Pacific Islander, 0.7% were other races, and 5.2% were Multiracial. The median duration of follow-up for safety after the booster dose was 204 days.

Solicited Adverse Reactions

Local and systemic adverse reactions and use of antipyretic medication were solicited in an electronic diary for 7 days following the injection (i.e., day of vaccination and the next 6 days) among participants receiving SPIKEVAX as a booster dose. Events that persisted for more than 7 days were followed until resolution.

Table 10 presents the frequency and severity of reported solicited local and systemic adverse reactions among SPIKEVAX booster dose recipients 12 years through 17 years of age within 7 days of a booster vaccination.

Table 10: Number and Percentage of Adolescents 12 Years Through 17 Years of Age with Solicited Local and Systemic Adverse Reactions Starting Within 7 Days* After the SPIKEVAX Booster Dose (Solicited Safety Set)†
 | SPIKEVAX; Booster Dose; N=1,335-1,351; n (%)
Local Adverse Reactions
Pain | 1,224 (90.6)
Pain, Grade 3a | 44 (3.3)
Axillary swelling/tenderness | 375 (27.8)
Axillary swelling/tenderness, Grade 3a | 5 (0.4)
Swelling (hardness) ≥25 mm | 180 (13.3)
Swelling (hardness), Grade 3b | 10 (0.7)
Erythema (redness) ≥25 mm | 121 (9.0)
Erythema (redness), Grade 3b | 10 (0.7)
Systemic Adverse Reactions
Fatigue | 784 (58.1)
Fatigue, Grade 3c | 54 (4.0)
Headache | 760 (56.3)
Headache, Grade 3d | 29 (2.1)
Myalgia | 542 (40.1)
Myalgia, Grade 3c | 49 (3.6)
Arthralgia | 322 (23.9)
Arthralgia, Grade 3c | 18 (1.3)
Chills | 408 (30.2)
Chills, Grade 3e | 7 (0.5)
Nausea/vomiting | 241 (17.9)
Nausea/vomiting, Grade 3f | 2 (0.1)
Fever | 81 (6.1)
Fever, Grade 3g | 8 (0.6)
Use of antipyretic or pain medicationh | 526 (38.9)
* 7 days included day of vaccination and the subsequent 6 days. Events and use of antipyretic or pain medication were collected in the electronic diary (e-diary).
† Absence of rows for Grade 4 adverse reactions indicates no events were reported.
N=Number of participants in the Solicited Safety Set who had available data for the solicited adverse reactions.
a Grade 3 pain and axillary swelling/tenderness: Defined as any use of prescription pain reliever; prevents daily activity.
b Grade 3 swelling and erythema: Defined as >100 mm / >10 cm.
c Grade 3 fatigue, myalgia, arthralgia: Defined as significant; prevents daily activity.
d Grade 3 headache: Defined as significant; any use of prescription pain reliever or prevents daily activity.
e Grade 3 chills: Defined as prevents daily activity and requires medical intervention.
f Grade 3 nausea/vomiting: Defined as prevents daily activity; requires outpatient intravenous hydration.
g Grade 3 fever: Defined as ≥39.0° – ≤40.0°C / ≥102.1° – ≤104.0°F.
h Percentage based on participants in the Solicited Safety Set (N=1,351).

In participants who received a booster dose, the median duration of solicited local and systemic adverse reactions was 2 to 3 days.

Unsolicited Adverse Events

Participants were monitored for unsolicited adverse events for up to 28 days following the booster dose. Serious adverse events and medically attended adverse events were recorded for the entire study duration. As of August 15, 2022, among the 1,405 participants who had received a booster dose of SPIKEVAX, unsolicited adverse events that occurred within 28 days following vaccination were reported by 14.9% of participants (n=209). In these analyses, 85.7% of study participants had at least 6 months of follow-up after the booster dose. Overall, there were no notable differences in the safety profiles observed between participants who had received a booster dose of SPIKEVAX and those who had received a primary series.

Serious Adverse Events

Through the cutoff date of August 15, 2022, with a median follow-up duration of 204 days after the booster dose, there were no serious adverse events considered causally related to the vaccine.

Single Dose (Bivalent Original and Omicron BA.4/BA.5) in Vaccine-Naïve Adolescents with Evidence of Prior SARS-CoV-2 Infection (Study 3)

Safety data for a single dose of Moderna COVID-19 Vaccine, Bivalent in adolescents were collected in a Phase 3 clinical trial with multiple parts. The open-label single dose portion of the study conducted in the United States and the Dominican Republic included 379 participants 12 years through 17 years of age who were COVID-19 vaccine-naïve and received a single 50 mcg dose of Moderna COVID-19 Vaccine, Bivalent (Study 3, NCT04649151). Overall, 52.8% were male, 47.2% were female, 94.5% were Hispanic or Latino, 10.3% were White, 32.2% were African American or Black, 56.7% were other races, and 0.8% were Multiracial. Of the 379 participants, 99.7% had evidence of prior SARS-CoV-2 infection at baseline (immunologic or virologic evidence of prior SARS-CoV-2 infection [defined as positive RT-PCR test and/or positive Elecsys immunoassay result at Day 1]). The median duration of follow-up for safety after vaccination was 35 days.

Solicited Adverse Reactions

Local and systemic adverse reactions and use of antipyretic medication were solicited in an electronic diary for 7 days following the injection (i.e., day of vaccination and the next 6 days) among participants receiving a single dose of Moderna COVID-19 Vaccine, Bivalent. Events that persisted for more than 7 days were followed until resolution.

Table 11 presents the frequency and severity of reported solicited local and systemic adverse reactions among Moderna COVID-19 Vaccine, Bivalent single dose recipients 12 years through 17 years of age within 7 days of vaccination.

Table 11: Number and Percentage of Adolescents 12 Years Through 17 Years of Age with Solicited Local and Systemic Adverse Reactions Starting Within 7 Days* After a Single Dose of Moderna COVID-19 Vaccine, Bivalent (Solicited Safety Set)†
 | Moderna COVID-19 Vaccine, Bivalent; Single Dose; N=377-378; n (%)
Local Adverse Reactions
Pain | 161 (42.6)
Pain, Grade 3a | 4 (1.1)
Axillary swelling/tenderness | 43 (11.4)
Axillary swelling/tenderness, Grade 3a | 1 (0.3)
Swelling (hardness) ≥25 mm | 10 (2.6)
Swelling (hardness), Grade 3b | 3 (0.8)
Erythema (redness) ≥25 mm | 11 (2.9)
Erythema (redness), Grade 3b | 6 (1.6)
Systemic Adverse Reactions
Fatigue | 46 (12.2)
Headache | 104 (27.6)
Headache, Grade 3c | 5 (1.3)
Myalgia | 59 (15.6)
Myalgia, Grade 3d | 1 (0.3)
Arthralgia | 37 (9.8)
Arthralgia, Grade 3d | 1 (0.3)
Chills | 20 (5.3)
Chills, Grade 3e | 1 (0.3)
Nausea/vomiting | 18 (4.8)
Fever | 30 (7.9)
Fever, Grade 3f | 10 (2.6)
Fever, Grade 4g | 1 (0.3)
Use of antipyretic or pain medicationh | 76 (20.1)
* 7 days included day of vaccination and the subsequent 6 days. Events and use of antipyretic or pain medication were collected in the electronic diary (e-diary).
† Absence of rows for Grade 3 or Grade 4 adverse reactions indicates no events were reported.
N=Number of participants in the Solicited Safety Set who had available data for the solicited adverse reactions.
a Grade 3 pain and axillary swelling/tenderness: Defined as any use of prescription pain reliever; prevents daily activity.
b Grade 3 swelling and erythema: Defined as >100 mm / >10 cm.
c Grade 3 headache: Defined as significant; any use of prescription pain reliever or prevents daily activity.
d Grade 3 myalgia and arthralgia: Defined as significant; prevents daily activity.
e Grade 3 chills: Defined as prevents daily activity and requires medical intervention.
f Grade 3 fever: Defined as ≥39.0° – ≤40.0°C / ≥102.1° – ≤104.0°F.
g Grade 4 fever: Defined as >40.0°C / >104.0°F.
h Percentage based on participants in the Solicited Safety Set (N=378).

The median duration of solicited local and systemic adverse reactions was 2 days.

Unsolicited Adverse Events

Participants were monitored for unsolicited adverse events for up to 28 days following vaccination. Serious adverse events and medically attended adverse events were recorded for the entire study duration. As of June 5, 2023, among the 379 participants who had received a single dose of Moderna COVID-19 Vaccine, Bivalent, unsolicited adverse events that occurred within 28 days following vaccination were reported by 12.9% of participants (n=49). In these analyses, 68.9% of study participants had at least 28 days of follow-up after vaccination. There were no unsolicited adverse events not already captured by solicited local and systemic reactions that were considered causally related to SPIKEVAX.

Serious Adverse Events

Through the cutoff date of June 5, 2023, with a median follow-up duration of 35 days after vaccination, serious adverse events were reported by 0.8% of participants (n=3). None of these events were considered to be related to vaccine.

Children 2 Years Through 11 Years of Age

2-Dose Series (Original Monovalent) in Vaccine-Naïve Children 6 Years Through 11 Years of Age (Study 4)

The safety of SPIKEVAX was evaluated in a Phase 2/3 clinical trial with multiple parts. The study included a randomized, placebo-controlled, observer-blind phase conducted in the United States and Canada involving 4,002 participants 6 years through 11 years of age who received at least one dose of SPIKEVAX (50 mcg mRNA; n=3,007) or placebo (n=995) (Study 4, NCT04796896). Participants started to enter an open-label, observational phase after November 1, 2021, in which placebo recipients were offered SPIKEVAX. A safety analysis was conducted in participants who received SPIKEVAX (n=3,708). In these analyses, the median duration of follow-up including both the blinded and open-label phases was 260 days after Dose 2 and 97.4% of study participants had at least 6 months of follow-up after Dose 2.

Overall, 50.8% were male, 49.2% were female, 18.5% were Hispanic or Latino, 65.6% were White, 10.1% were Black or African American, 9.9% were Asian, 0.4% were American Indian or Alaska Native, <0.1% were Native Hawaiian or Pacific Islander, 2.1% were other races, and 10.7% were Multiracial. Demographic characteristics were similar among participants who received SPIKEVAX and those who received placebo.

Solicited Adverse Reactions

Local and systemic adverse reactions and use of antipyretic medication were solicited in an electronic diary for 7 days following each injection (i.e., day of vaccination and the next 6 days) among participants receiving SPIKEVAX (n=3,005) and participants receiving placebo (n=994) with at least 1 documented dose. Events that persisted for more than 7 days were followed until resolution. Solicited adverse reactions were reported more frequently among vaccine participants than placebo participants.

The reported number and percentage of the solicited local and systemic adverse reactions in participants 6 years through 11 years of age by dose are presented in Table 12.

Table 12: Number and Percentage of Participants With Solicited Local and Systemic Adverse Reactions Starting Within 7 Days* After Each Dose in Participants 6 Years Through 11 Years (Solicited Safety Set, Dose 1 and Dose 2)†
 | SPIKEVAX |  | Placeboa
 | Dose 1; (N=3,003); n (%) | Dose 2; (N=2,993); n (%) | Dose 1; (N=993); n (%) | Dose 2; (N=970); n (%)
Local Adverse Reactions
Pain | 2,794; (93.0) | 2,839; (94.9) | 466; (46.9) | 479; (49.4)
Pain, Grade 3b | 28; (0.9) | 81; (2.7) | 0; (0) | 2; (0.2)
Axillary (or groin) swelling/tenderness | 464; (15.5) | 539; (18.0) | 84; (8.5) | 65; (6.7)
Axillary (or groin) swelling/tenderness, Grade 3b | 3; (<0.1) | 3; (0.1) | 1; (0.1) | 2; (0.2)
Swelling (hardness); ≥25 mm | 353; (11.8) | 507; (16.9) | 11; (1.1) | 12; (1.2)
Swelling (hardness), Grade 3: >100 mm | 19; (0.6) | 20; (0.7) | 1; (0.1) | 0; (0)
Erythema (redness); ≥25 mm | 350; (11.7) | 561; (18.7) | 13; (1.3) | 9; (0.9)
Erythema (redness), Grade 3: >100 mm | 16; (0.5) | 33; (1.1) | 1; (0.1) | 1; (0.1)
Systemic Adverse Reactions
Fatigue | 1,298; (43.2) | 1,927; (64.4) | 335; (33.7) | 335; (34.5)
Fatigue, Grade 3c | 32; (1.1) | 191; (6.4) | 8; (0.8) | 8; (0.8)
Headache | 938; (31.2) | 1,626; (54.3) | 307; (30.9) | 275; (28.4)
Headache, Grade 3c | 18; (0.6) | 119; (4.0) | 4; (0.4) | 8; (0.8)
Myalgia | 438; (14.6) | 844; (28.2) | 96; (9.7) | 104; (10.7)
Myalgia, Grade 3c | 11; (0.4) | 71; (2.4) | 1; (0.1) | 1; (0.1)
Arthralgia | 260; (8.7) | 484; (16.2) | 75; (7.6) | 84; (8.7)
Arthralgia, Grade 3c | 3; (<0.1) | 25; (0.8) | 1; (0.1) | 0; (0)
Chills | 309; (10.3) | 906; (30.3) | 67; (6.7) | 73; (7.5)
Chills, Grade 3d | 3; (<0.1) | 19; (0.6) | 0; (0) | 0; (0)
Nausea/vomiting | 327; (10.9) | 717; (24.0) | 107; (10.8) | 97; (10.0)
Nausea/vomiting,; Grade 3b | 5; (0.2) | 19; (0.6) | 0; (0) | 0; (0)
Fever; ≥38.0°C / ≥100.4°F | 98; (3.3) | 717; (24.0) | 15; (1.5) | 18; (1.9)
Fever,; Grade 3: 39.0° - 40.0°C / 102.1° - 104.0°F | 17; (0.6) | 114; (3.8) | 2; (0.2) | 2; (0.2)
Use of antipyretic or pain medication | 730; (24.3) | 1,429; (47.7) | 95; (9.6) | 93; (9.6)
* 7 days included day of vaccination and the subsequent 6 days. Events and use of antipyretic or pain medication were collected in the electronic diary (e-diary).
† No Grade 4 adverse reactions were reported.
a Placebo was a saline solution.
b Grade 3 pain, axillary (or groin) swelling/tenderness, nausea/vomiting: Defined as prevents daily activity.
c Grade 3 fatigue, headache, myalgia, arthralgia: Defined as significant; prevents daily activity.
d Grade 3 chills: Defined as prevents daily activity and requires medical intervention.

Solicited local and systemic adverse reactions reported following administration of SPIKEVAX had a median duration of 2 to 3 days.

An assessment of reactogenicity among participants with evidence of prior SARS-CoV-2 infection (immunologic or virologic evidence of prior SARS-CoV-2 infection [defined as positive RT-PCR test and/or positive Elecsys immunoassay result at Day 1]) compared to those with no evidence of infection at baseline (negative RT-PCR test and negative Elecsys immunoassay result at Day 1) was conducted. In ages 6 years through 11 years, 8.6% of participants (vaccine=257, placebo=87) had evidence of prior SARS-CoV-2 infection at baseline. Fever (temperature ≥38°C) and headache were reported in a greater proportion of baseline SARS-CoV-2 positive vaccine participants compared to baseline SARS-CoV-2 negative vaccine participants. There were no notable differences in other solicited adverse reactions.

Unsolicited Adverse Events

Participants were monitored for unsolicited adverse events for 28 days following each dose. Serious adverse events and medically attended adverse events were recorded for the entire study duration. Among the 4,002 participants who had received at least 1 dose of vaccine (n=3,007) or placebo (n=995), unsolicited adverse events that occurred within 28 days following any vaccination were reported by 26.1% of participants (n=785) who received SPIKEVAX and 20.8% of participants (n=207) who received placebo. A 7-year-old female experienced a moderate, nonserious event of alopecia areata 27 days after receiving Dose 1. The participant received Dose 2. The event was considered related to the vaccine and was ongoing when the participant discontinued from the study at Day 255 due to withdrawal of consent.

There were no notable patterns or numerical imbalances between treatment groups for specific categories of adverse events that would suggest a causal relationship to SPIKEVAX.

Serious Adverse Events

During the blinded portion of the study, serious adverse events were reported by 0.3% of participants (n=8) who received SPIKEVAX and 0.1% of participants (n=1) who received placebo. In the open-label phase, an additional 17 SPIKEVAX recipients reported serious adverse events. There were no serious adverse events considered causally related to the vaccine.

2-Dose Series (Original Monovalent) in Vaccine-Naïve Infants and Children 2 Years Through 5 Years of Age (Study 4)

The safety of SPIKEVAX was evaluated in a Phase 2/3 clinical trial with multiple parts. The study included a randomized, placebo-controlled, observer-blind phase conducted in the United States and Canada involving 6,698 participants 6 months through 5 years of age who received at least one dose of SPIKEVAX (25 mcg mRNA; n=5,025) or placebo (n=1,673) (Study 4, NCT04796896). Participants started to enter an open-label, observational phase after June 17, 2022, in which placebo recipients were unblinded and offered SPIKEVAX. A safety analysis was conducted in 3,671 participants 2 years through 5 years of age who received SPIKEVAX. In these analyses, the median duration of follow-up including both the blinded and open-label phases for participants 2 years through 5 years of age was 330 days after Dose 2 and 84.9% of study participants had at least 6 months of follow-up after Dose 2.

For participants 2 years through 5 years of age, 50.8% were male, 49.2% were female, 14.1% were Hispanic or Latino, 76.5% were White, 4.5% were Black or African American, 6.0% were Asian, 0.3% were American Indian or Alaska Native, 0.2% were Native Hawaiian or Pacific Islander, 1.5% were other races, and 10.5% were Multiracial. Demographic characteristics were similar among participants who received SPIKEVAX and those who received placebo.

Solicited Adverse Reactions

Local and systemic adverse reactions and use of antipyretic medication were solicited in an electronic diary for 7 days following each injection (i.e., day of vaccination and the next 6 days) among participants receiving SPIKEVAX and participants receiving placebo with at least 1 documented dose (for participants 24 months to 36 months, vaccine=983, placebo=340; for participants 37 months to 5 years, vaccine=2,031, placebo=658). Events that persisted for more than 7 days were followed until resolution. Solicited adverse reactions were reported more frequently among vaccine participants than placebo participants.

The reported number and percentage of the solicited local and systemic adverse reactions by dose in participants 24 months through 36 months of age are presented in Table 13 and participants 37 months to 5 years of age are presented in Table 14.

Table 13: Number and Percentage of Participants With Solicited Local and Systemic Adverse Reactions Starting Within 7 Days* After Each Dose in Participants 24 Months Through 36 Months (Solicited Safety Set, Dose 1 and Dose 2)†
 | SPIKEVAX |  | Placeboa
 | Dose 1; (N=941); n (%) | Dose 2; (N=972); n (%) | Dose 1; (N=322); n (%) | Dose 2; (N=338); n (%)
Local Adverse Reactions
Pain | 500; (53.3) | 663; (68.2) | 119; (37.0) | 149; (44.2)
Pain, Grade 3b | 3; (0.3) | 5; (0.5) | 0; (0) | 0; (0)
Axillary (or groin) swelling/tenderness | 49; (5.2) | 85; (8.7) | 18; (5.6) | 15; (4.5)
Axillary (or groin) swelling/tenderness, Grade 3b | 0; (0) | 1; (0.1) | 0; (0) | 0; (0)
Erythema (redness); ≥5 mm | 94; (10.0) | 118; (12.1) | 13; (4.0) | 11; (3.3)
Erythema (redness),; Grade 3: >50 mm | 6; (0.6) | 9; (0.9) | 2; (0.6) | 0; (0)
Swelling (hardness); ≥5 mm | 77; (8.2) | 112; (11.5) | 11; (3.4) | 8; (2.4)
Swelling (hardness),; Grade 3: >50 mm | 5; (0.5) | 8; (0.8) | 2; (0.6) | 0; (0)
Systemic Adverse Reactions
Irritability/crying | 511; (54.5) | 532; (54.7) | 163; (51.1) | 153; (45.5)
Irritability/crying,; Grade 3c | 12; (1.3) | 10; (1.0) | 5; (1.6) | 3; (0.9)
Sleepiness | 284; (30.3) | 352; (36.2) | 92; (28.8) | 90; (26.8)
Sleepiness, Grade 3d | 2; (0.2) | 1; (0.1) | 0; (0) | 0; (0)
Loss of appetite | 225; (24.0) | 300; (30.9) | 71; (22.3) | 69; (20.5)
Loss of appetite,; Grade 3e | 7; (0.7) | 8; (0.8) | 2; (0.6) | 0; (0)
Fever; ≥38.0°C / ≥100.4°F | 108; (11.5) | 187; (19.2) | 26; (8.1) | 37; (10.9)
Fever,; Grade 3: 39.6° - 40.0°C /; 103.2° - 104.0°F | 4; (0.4) | 15; (1.5) | 4; (1.2) | 0; (0)
Fever,; Grade 4: >40.0°C / >104.0°F | 4; (0.4) | 3; (0.3) | 1; (0.3) | 0; (0)
Use of antipyretic or pain medication | 193; (20.5) | 294; (30.2) | 60; (18.6) | 63; (18.6)
* 7 days included day of vaccination and the subsequent 6 days. Events and use of antipyretic or pain medication were collected in the electronic diary (e-diary).
† Absence of rows for Grade 3 or Grade 4 adverse reactions indicates no events were reported.
N=Number of participants in the Solicited Safety Set who had available data for the solicited adverse reactions. Included 29 individuals younger than 2 years of age randomized in the 2 years through 5 years of age group stratum (18 in the SPIKEVAX group and 11 in the placebo group). All of these 29 individuals had e-diary for 6 months through 36 months age group.
a Placebo was a saline solution.
b Grade 3 pain, axillary (or groin) swelling/tenderness: Defined as prevents daily activity.
c Grade 3 irritability/crying: Defined as lasting >3 hours or inconsolable.
d Grade 3 sleepiness: Defined as sleeps most of the time, hard to arouse.
e Grade 3 loss of appetite: Defined as missed >2 feeds/meals completely or refuses most feeds/meals.

Table 14: Number and Percentage of Participants With Solicited Local and Systemic Adverse Reactions Starting Within 7 Days* After Each Dose in Participants 37 Months Through 5 Years (Solicited Safety Set, Dose 1 and Dose 2)†
 | SPIKEVAX |  | Placeboa
 | Dose 1; (N=2,014); n (%) | Dose 2; (N= 2,005); n (%) | Dose 1; (N=649); n (%) | Dose 2; (N= 636); n (%)
Local Adverse Reactions
Pain | 1,313; (65.2) | 1,464; (73.0) | 263; (40.5) | 253; (39.8)
Pain, Grade 3b | 1; (<0.1) | 6; (0.3) | 0; (0) | 0; (0)
Axillary (or groin) swelling/tenderness | 157; (7.8) | 186; (9.3) | 38; (5.9) | 18; (2.8)
Erythema (redness); ≥25 mm | 72; (3.6) | 147; (7.3) | 1; (0.2) | 6; (0.9)
Erythema (redness),; Grade 3: >100 mm | 6; (0.3) | 4; (0.2) | 1; (0.2) | 0; (0)
Swelling (hardness); ≥25 mm | 60; (3.0) | 135; (6.7) | 6; (0.9) | 5; (0.8)
Swelling (hardness),; Grade 3: >100 mm | 5; (0.2) | 6; (0.3) | 0; (0) | 0; (0)
Systemic Adverse Reactions
Fatigue | 807; (40.1) | 962; (48.0) | 236; (36.4) | 187; (29.4)
Fatigue, Grade 3b | 21; (1.0) | 45; (2.2) | 11; (1.7) | 9; (1.4)
Headache | 232; (11.5) | 313; (15.6) | 78; (12.0) | 52; (8.2)
Headache, Grade 3b | 5; (0.2) | 8; (0.4) | 2; (0.3) | 1; (0.2)
Fever; ≥38.0°C / ≥100.4°F | 154; (7.6) | 316; (15.8) | 33; (5.1) | 28; (4.4)
Fever,; Grade 3: 39.0° - 40.0°C /; 102.1° - 104.0°F | 23; (1.1) | 58; (2.9) | 4; (0.6) | 2; (0.3)
Fever,; Grade 4: >40.0°C / >104.0°F | 0; (0) | 2; (<0.1) | 1; (0.2) | 0; (0)
Myalgia | 200; (9.9) | 312; (15.6) | 59; (9.1) | 48; (7.5)
Myalgia, Grade 3b | 5; (0.2) | 9; (0.4) | 2; (0.3) | 3; (0.5)
Chills | 129; (6.4) | 246; (12.3) | 40; (6.2) | 31; (4.9)
Chills, Grade 3b | 1; (<0.1) | 4; (0.2) | 0; (0) | 2; (0.3)
Nausea/vomiting | 137; (6.8) | 195; (9.7) | 50; (7.7) | 32; (5.0)
Nausea/vomiting,; Grade 3b | 7; (0.3) | 7; (0.3) | 2; (0.3) | 0; (0)
Arthralgia | 124; (6.2) | 170; (8.5) | 32; (4.9) | 29; (4.6)
Arthralgia, Grade 3b | 2; (<0.1) | 3; (0.1) | 1; (0.2) | 0; (0)
Use of antipyretic or pain medication | 305; (15.1) | 517; (25.8) | 62; (9.6) | 43; (6.8)
* 7 days included day of vaccination and the subsequent 6 days. Events and use of antipyretic or pain medication were collected in the electronic diary (e-diary).
† Absence of rows for Grade 3 or Grade 4 adverse reactions indicates no events were reported.
a Placebo was a saline solution.
b Grade 3 pain, fatigue, headache, myalgia, arthralgia, chills, nausea/vomiting: Defined as prevents daily activity.

Solicited local and systemic adverse reactions reported following administration of SPIKEVAX had a median duration of 2 days for participants 2 years through 5 years of age.

Solicited Adverse Reactions Among Participants with Evidence of Prior SARS-CoV-2 Infection

An assessment of reactogenicity among participants with evidence of prior SARS-CoV-2 infection (immunologic or virologic evidence of prior SARS-CoV-2 infection [defined as positive RT-PCR test and/or positive Elecsys immunoassay result at Day 1]) compared to those with no evidence of infection at baseline (negative RT-PCR test and negative Elecsys immunoassay result at Day 1) was conducted. In the 2 years through 5 years of age cohort, 8.6% of participants (vaccine=267, placebo=82) had evidence of prior SARS-CoV-2 infection at baseline. Fever (temperature ≥38°C) was reported in a greater proportion of baseline SARS-CoV-2 positive vaccine participants compared to baseline SARS-CoV-2 negative vaccine participants. There were no notable differences in other solicited adverse reactions.

Unsolicited Adverse Events

Participants were monitored for unsolicited adverse events for up to 28 days following each dose. Serious adverse events and medically attended adverse events were recorded for the entire study duration. In the blinded phase, among participants 2 years through 5 years of age who had received at least 1 dose of vaccine or placebo (vaccine=3,031, placebo=1,007), unsolicited adverse events that occurred within 28 days following each vaccination were reported by 35.9% of participants (n=1,087) who received SPIKEVAX and 32.3% of participants (n=325) who received placebo. In these analyses, 95.2% of study participants had at least 28 days of follow-up after Dose 2. A 3-year-old male participant experienced mild erythema multiforme (bilateral arms) 3 days after receiving Dose 2 which resolved the next day without treatment. The event was considered related to the vaccine.

Serious Adverse Events

During the blinded part of the study, serious adverse events were reported by 0.6% of participants (n=19) who received vaccine and 0.3% of participants (n=3) who received placebo who were 2 years through 5 years of age. In the open-label phase, an additional 21 SPIKEVAX recipients reported serious adverse events. None of the events were considered related to vaccine.

There were no notable patterns or imbalances between treatment groups for specific categories of serious adverse events that would suggest a causal relationship to SPIKEVAX.

Single Dose (Monovalent Omicron XBB.1.5) in Vaccine-Naïve Children 2 Years Through 4 Years of Age (Study 6)

Safety data for a single dose of SPIKEVAX (2023-2024 Formula) in individuals 2 years through 4 years of age were collected in an ongoing Phase 3 open-label clinical trial with multiple parts (Study 6, NCT05436834). The single dose phase of the study conducted in the United States, Panama, and the Dominican Republic involved 199 participants 2 years through 4 years of age who were COVID-19 vaccine-naïve and received a single 25 mcg dose of SPIKEVAX (2023-2024 Formula). Overall, 50.3% were male, 49.7% were female, 69.3% were Hispanic or Latino, 24.1% were White, 33.2% were Black or African American, 0.5% were American Indian or Alaska Native, 36.7% were other races, and 5.5% were Multiracial. In these analyses, the median duration of follow-up after vaccination was 92 days and 99.5% of study participants had at least 3 months of follow-up.

Solicited Adverse Reactions

Local and systemic adverse reactions and use of antipyretic medication were solicited in an electronic diary for 7 days following the injection (i.e., day of vaccination and the next 6 days) among participants receiving SPIKEVAX (2023-2024 Formula). Events that persisted for more than 7 days were followed until resolution.

Table 15 presents the frequency and severity of reported solicited local and systemic adverse reactions among SPIKEVAX (2023-2024 Formula) single dose recipients 2 years through 4 years of age within 7 days of vaccination.

Table 15: Number and Percentage of Participants 2 Years Through 4 Years of Age With Solicited Local and Systemic Adverse Reactions Starting Within 7 Days* After a Single Dose of SPIKEVAX (2023-2024 Formula) (Solicited Safety Set)†
 | SPIKEVAX (2023-2024 Formula) Single Dose (N=199) n (%)
Local Adverse Reactions
Pain | 55 (27.6)
Pain, Grade 3a | 2 (1.0)
Erythema (redness) ≥5 mm | 7 (3.5)
Swelling (hardness) ≥5 mm | 7 (3.5)
Axillary (or groin) swelling/tenderness | 14 (7.0)
Axillary (or groin) swelling/tenderness, Grade 3a | 3 (1.5)
Systemic Adverse Reactions
Irritability/crying | 24 (12.1)
Irritability/crying, Grade 3b | 2 (1.0)
Sleepiness | 25 (12.6)
Sleepiness, Grade 3c | 2 (1.0)
Loss of appetite | 17 (8.5)
Loss of appetite, Grade 3d | 1 (0.5)
Fever ≥38.0°C / ≥100.4°F | 17 (8.5)
Fever, Grade 3: 39.6° - 40.0°C / 103.2° - 104.0°F | 2 (1.0)
Use of antipyretic or pain medication | 34 (17.1)
* 7 days included day of vaccination and the subsequent 6 days. Events and use of antipyretic or pain medication were collected in the electronic diary (e-diary).
† Absence of rows for Grade 3 or Grade 4 adverse reactions indicates no events were reported.
a Grade 3 pain, axillary (groin) swelling/tenderness: Defined as prevents daily activity.
b Grade 3 irritability/crying: Defined as lasting >3 hours or inconsolable.
c Grade 3 sleepiness: Defined as sleeps most of the time, hard to arouse.
d Grade 3 loss of appetite: Defined as missed >2 feeds/meals completely or refuses most feeds/meals.

The median duration of solicited local and systemic adverse reactions was 1 day in participants 2 years through 4 years of age.

Unsolicited Adverse Events

Participants were monitored for unsolicited adverse events for up to 28 days following vaccination. Serious adverse events and medically attended adverse events were recorded for the entire study duration. Among participants 2 years through 4 years of age who had received a single dose of SPIKEVAX (2023-2024 Formula), unsolicited adverse events that occurred within 28 days following vaccination were reported by 19.6% of participants (n=39). In these analyses, all study participants had at least 28 days of follow-up after vaccination. There were no unsolicited adverse events assessed as related to SPIKEVAX (2023-2024 Formula).

Serious Adverse Events

Through the end of this part of the study for participants 2 years through 4 years of age, with a median follow-up duration of 92 days after vaccination, no serious adverse events were reported.

2-Dose Series (Bivalent Original and Omicron BA.1) in Vaccine-Naive Children 2 Years Through 5 Years of Age (Study 6)

Safety data for bivalent vaccine (Original and Omicron BA.1) in individuals 6 months through 5 years of age were collected in an ongoing Phase 3 open-label clinical trial with multiple parts. The study included a phase conducted in the United States involving 391 participants 6 months through 5 years of age who received at least one dose of bivalent vaccine (Original and Omicron BA.1) (25 mcg mRNA) (Study 6, NCT05436834). A safety analysis was conducted in 261 participants 2 years through 5 years of age who received bivalent vaccine (Original and Omicron BA.1). In this analysis, 52.5% were male, 47.5% were female, 18.4% were Hispanic or Latino, 54.4% were White, 37.5% were Black or African American, 0.8% were Asian, 1.5% were American Indian or Alaska Native, 0.4% were other races, and 5.4% were Multiracial. The median duration of follow-up was 358 days after Dose 2 and 92.7% of study participants had at least 6 months of follow-up after Dose 2.

Unsolicited Adverse Events

Participants were monitored for unsolicited adverse events for up to 28 days following each dose. Serious adverse events and medically attended adverse events were recorded for the entire study duration. Among participants 2 years through 5 years of age who had received at least 1 dose of vaccine (n=261), unsolicited adverse events that occurred within 28 days following each vaccination were reported by 30.7% of participants (n=80). In these analyses, 96.6% of study participants had at least 28 days of follow-up after Dose 2.

Serious Adverse Events

Through the end of the open-label phase, serious adverse events were reported by 0.8% of participants 2 years through 5 years of age who received vaccine (n=2). None of the events were considered related to vaccine.

Single Dose (Original Monovalent) in Vaccine-Experienced Children 6 Years Through 11 Years of Age (Study 4)

Safety data for a booster dose of SPIKEVAX in individuals 6 years through 11 years of age were collected in a Phase 2/3 clinical trial with multiple parts. The open-label booster phase of the study involved 2,290 participants 6 years through 11 years of age who received a booster dose of SPIKEVAX (25 mcg mRNA) at least 6 months after the second dose of the primary series (Study 4, NCT04796896). Overall, 52.6% were male, 47.4% were female, 16.9% were Hispanic or Latino, 65.6% were White, 11.1% were Black or African American, 8.2% were Asian, 0.5% were American Indian or Alaska Native, 0.1% were Native Hawaiian or Pacific Islander, 2.1% were other races, and 11.5% were Multiracial. The median duration of follow-up for safety after the booster dose was 368 days and 96.9% had at least 6 months of follow-up.

Solicited Adverse Reactions

Local and systemic adverse reactions and use of antipyretic medication were solicited in an electronic diary for 7 days following the injection (i.e., day of vaccination and the next 6 days) among participants receiving SPIKEVAX. Events that persisted for more than 7 days were followed until resolution.

Table 16 presents the frequency and severity of reported solicited local and systemic adverse reactions among SPIKEVAX booster dose recipients 6 years through 11 years of age within 7 days of a booster vaccination.

Table 16: Number and Percentage of Participants 6 Years Through 11 Years of Age With Solicited Local and Systemic Adverse Reactions Starting Within 7 Days* After the SPIKEVAX Booster Dose (Solicited Safety Set)†
 | SPIKEVAX; Booster Dose; (N=2,259); n (%)
Local Adverse Reactions
Pain | 2,010 (89.1)
Pain, Grade 3a | 27 (1.2)
Axillary (or groin) swelling/tenderness | 570 (25.3)
Axillary (or groin) swelling/tenderness, Grade 3a | 6 (0.3)
Swelling (hardness) ≥25 mm | 218 (9.7)
Swelling (hardness), Grade 3: >100 mm | 7 (0.3)
Erythema (redness) ≥25 mm | 213 (9.4)
Erythema (redness), Grade 3: >100 mm | 7 (0.3)
Systemic Adverse Reactions
Fatigue | 1,018 (45.1)
Fatigue, Grade 3b | 56 (2.5)
Headache | 799 (35.4)
Headache, Grade 3b | 30 (1.3)
Myalgia | 434 (19.2)
Myalgia, Grade 3b | 23 (1.0)
Arthralgia | 253 (11.2)
Arthralgia, Grade 3b | 14 (0.6)
Chills | 281 (12.5)
Chills, Grade 3c | 5 (0.2)
Nausea/vomiting | 272 (12.1)
Nausea/vomiting, Grade 3a | 11 (0.5)
Fever ≥38.0°C / ≥100.4°F | 151 (6.7)
Fever, Grade 3: 39.0° - 40.0°C / 102.1° - 104.0°F | 23 (1.0)
Fever, Grade 4: >40° C / >104.0°F | 1 (<0.1)
Use of antipyretic or pain medication | 738 (32.7)
* 7 days included day of vaccination and the subsequent 6 days. Events and use of antipyretic or pain medication were collected in the electronic diary (e-diary).
† Absence of rows for Grade 4 adverse reactions indicates no events were reported.
a Grade 3 pain, axillary (or groin) swelling/tenderness, nausea/vomiting: Defined as prevents daily activity.
b Grade 3 fatigue, headache, myalgia, arthralgia: Defined as significant; prevents daily activity.
c Grade 3 chills: Defined as prevents daily activity and requires medical intervention.

In participants who received a booster dose, the median duration of solicited local and systemic adverse reactions was 2 days.

Unsolicited Adverse Events

Participants were monitored for unsolicited adverse events for up to 28 days following the booster dose. Serious adverse events and medically attended adverse events were recorded for the entire study duration. Among the 2,290 participants who had received a booster dose of SPIKEVAX, unsolicited adverse events that occurred within 28 days following vaccination were reported by 10.0% of participants (n=229). In these analyses, 96.9% of study participants had at least 6 months of follow-up after the booster dose. A nonserious event of serum sickness-like reaction with onset 10 days following administration of a booster dose was reported in an 8-year-old male participant. This event was mild and assessed as related to vaccination. After initiation of treatment with antihistamines and steroids, symptoms resolved and the event was considered resolved 47 days after onset.

Serious Adverse Events

Through the end of the open-label booster phase of this study, serious adverse events were reported by 0.4% of participants (n=10) who received a booster dose. None of the events were considered causally related to the vaccine.

Single Dose (Bivalent Original and Omicron BA.1) in Vaccine-Experienced Children 2 Years Through 5 Years of Age (Study 6)

Safety data for a booster dose of bivalent vaccine (Original and Omicron BA.1) in individuals 6 months through 5 years of age were collected in an ongoing Phase 3 open-label clinical trial with multiple parts (Study 6, NCT05436834). The booster phase of the study conducted in the United States involved 539 participants 6 months through 5 years of age who received a booster dose of bivalent vaccine (Original and Omicron BA.1) (10 mcg mRNA) at least 4 months (range 4-12; median 8 months) after the second dose of the SPIKEVAX primary series. A safety analysis was conducted in 425 participants 2 years through 5 years of age. In this analysis, 52.7% were male, 47.3% were female, 12.2% were Hispanic or Latino, 81.4% were White, 3.8% were Black or African American, 4.7% were Asian, 0.2% were Native Hawaiian or Pacific Islander, and 8.9% were Multiracial. The median duration of follow-up after the booster dose was 184 days and 97.2% of study participants had at least 6 months of follow-up.

Solicited Adverse Reactions

Solicited local and systemic adverse reactions in participants 24 months through 36 months of age (n=145) starting within 7 days after administration of a booster dose included irritability/crying (51.3%), pain at the injection site (36.6%), sleepiness (23.5%), loss of appetite (18.3%), swelling at the injection site (7.6%), erythema at the injection site (6.9%), fever (6.9%), and axillary (or groin) swelling/tenderness (3.4%).

Solicited local and systemic adverse reactions in participants 37 months through 5 years of age (n=281) starting within 7 days after administration of a booster dose included pain at the injection site (54.8%), fatigue (32.1%), headache (14.2%), myalgia (12.4%), arthralgia (9.1%), axillary (or groin) swelling/tenderness (8.2%), nausea/vomiting (8.0%), fever (6.0%), chills (5.8%), erythema at the injection site (4.3%), and swelling at the injection site (3.6%).

No Grade 4 adverse reactions were reported. In participants 2 years through 5 years of age who received a booster dose, the median duration of solicited local and systemic adverse reactions was 1 day.

Unsolicited Adverse Events

Participants were monitored for unsolicited adverse events for up to 28 days following the booster dose. Serious adverse events and medically attended adverse events were recorded for the entire study duration. Among participants 2 years through 5 years of age who received a booster dose of bivalent vaccine (Original and Omicron BA.1), unsolicited adverse events that occurred within 28 days following vaccination were reported by 18.4% of participants (n=78). In these analyses, 99.8% of study participants had at least 28 days of follow-up after the booster dose.

Serious Adverse Events

Through the end of this part of the study, serious adverse events were reported by 0.9% of participants 2 years through 5 years of age who received a booster dose (n=4). None of the events were considered causally related to the vaccine.

Single Dose (Bivalent Original and Omicron BA.1) in Vaccine-Experienced Children 2 Years Through 5 Years of Age (Study 4)

Safety data for a booster dose of bivalent vaccine (Original and Omicron BA.1) were collected in participants 6 months through 5 years of age in a Phase 2/3 clinical trial with multiple parts. The open-label booster portion of the study involved 1,514 participants 2 years through 5 years of age who received a booster dose of bivalent vaccine (Original and Omicron BA.1) (10 mcg mRNA) at least 6 months (range 3-18 months; median 12 months) after the second dose of the SPIKEVAX primary series (Study 4, NCT04796896). Safety data included medically attended adverse events and serious adverse events collected for the duration of the study. In this analysis, 51.2% were male, 48.8% were female, 12.7% were Hispanic or Latino, 75.8% were White, 5.2% were African American, 5.1% were Asian, 0.5% were American Indian or Alaska Native, 0.1% were Native Hawaiian or Pacific Islander, 1.0% were other races, and 11.9% were Multiracial. The median duration of follow-up for safety after the booster dose was 184 days and 95.6% had at least 6 months of follow-up.

Through the end of this part of the study, serious adverse events were reported by 0.9% of participants 2 years through 5 years of age who received a booster dose (n=13). None of the events were considered causally related to the vaccine.

Infants and Children 6 Months Through 23 Months of Age

2-Dose Series (Original Monovalent) in Vaccine-Naïve Infants and Children 6 Months Through 23 Months of Age (Study 4)

The safety of SPIKEVAX was evaluated in a Phase 2/3 clinical trial with multiple parts. The study included a randomized, placebo-controlled, observer-blind phase conducted in the United States and Canada involving 6,698 participants 6 months through 5 years of age who received at least one dose of SPIKEVAX (25 mcg mRNA; n=5,025) or placebo (n=1,673) (Study 4, NCT04796896). Participants started to enter an open-label, observational phase after June 17, 2022, in which placebo recipients were unblinded and offered SPIKEVAX. A safety analysis was conducted in 2,438 participants 6 months through 23 months of age who received SPIKEVAX. In these analyses, the median duration of follow-up including both the blinded and open-label phases for participants 6 months through 23 months of age was 314 days after Dose 2 and 80.7% of study participants had at least 6 months of follow-up after Dose 2.

For participants 6 months through 23 months of age, 50.3% were male, 49.7% were female, 13.2% were Hispanic or Latino, 78.6% were White, 3.0% were Black or African American, 5.0% were Asian, 0.3% were American Indian or Alaska Native, 1.5% were other races, and 10.9% were Multiracial. Demographic characteristics were similar among participants who received SPIKEVAX and those who received placebo.

Solicited Adverse Reactions

Local and systemic adverse reactions and use of antipyretic medication were solicited in an electronic diary for 7 days following each injection (i.e., day of vaccination and the next 6 days) among participants receiving SPIKEVAX and participants receiving placebo with at least 1 documented dose (vaccine=1,991, placebo=664). Events that persisted for more than 7 days were followed until resolution. Solicited adverse reactions were reported more frequently among vaccine participants than placebo participants.

The reported number and percentage of the solicited local and systemic adverse reactions by dose in participants 6 months through 23 months of age are presented in Table 17.

Table 17: Number and Percentage of Participants With Solicited Local and Systemic Adverse Reactions Starting Within 7 Days* After Each Dose in Participants 6 Months Through 23 Months (Solicited Safety Set, Dose 1 and Dose 2)†
 | SPIKEVAX |  | Placeboa
 | Dose 1; (N= 1,982); n (%) | Dose 2; (N=1,975); n (%) | Dose 1; (N= 661); n (%) | Dose 2; (N=646); n (%)
Local Adverse Reactions
Pain | 722; (36.5) | 893; (45.2) | 196; (29.7) | 169; (26.2)
Pain, Grade 3b | 0; (0) | 1; (<0.1) | 0; (0) | 0; (0)
Axillary (or groin) swelling/tenderness | 116; (5.9) | 173; (8.8) | 31; (4.7) | 31; (4.8)
Erythema (redness); ≥5 mm | 171; (8.6) | 270; (13.7) | 25; (3.8) | 25; (3.9)
Erythema (redness); Grade 3: >50 mm | 6; (0.3) | 17; (0.9) | 2; (0.3) | 0; (0)
Swelling (hardness); ≥5 mm | 166; (8.4) | 293; (14.8) | 20; (3.0) | 16; (2.5)
Swelling (hardness); Grade 3: >50 mm | 6; (0.3) | 17; (0.9) | 0; (0) | 0; (0)
Systemic Adverse Reactions
Irritability/crying | 1,325; (67.3) | 1,270; (64.5) | 412; (62.5) | 382; (59.2)
Irritability/crying,; Grade 3c | 25; (1.3) | 31; (1.6) | 7; (1.1) | 5; (0.8)
Sleepiness | 723; (36.7) | 702; (35.7) | 243; (36.9) | 227; (35.2)
Sleepiness, Grade 3d | 4; (0.2) | 3; (0.2) | 1; (0.2) | 1; (0.2)
Loss of appetite | 579; (29.4) | 625; (31.8) | 177; (26.9) | 171; (26.5)
Loss of appetite,; Grade 3e | 13; (0.7) | 18; (0.9) | 1; (0.2) | 2; (0.3)
Fever; >38.0°C / ≥100.4°F | 204; (10.3) | 280; (14.2) | 58; (8.8) | 54; (8.4)
Fever,; Grade 3: 39.6° - 40.0°C / 103.2° - 104.0°F | 12; (0.6) | 9; (0.5) | 3; (0.5) | 7; (1.1)
Fever,; Grade 4: >40.0°C / >104.0°F | 1; (<0.1) | 5; (0.3) | 1; (0.2) | 0; (0)
Use of antipyretic or pain medication | 527; (26.6) | 648; (32.8) | 161; (24.4) | 134; (20.7)
* 7 days included day of vaccination and the subsequent 6 days. Events and use of antipyretic or pain medication were collected in the electronic diary (e-diary).
† Absence of rows for Grade 3 or Grade 4 adverse reactions indicates no events were reported.
N=Included 6 individuals aged 2 years through 4 years randomized in the 6 months through 23 months of age group stratum (all in the SPIKEVAX group).
a Placebo was a saline solution.
b Grade 3 pain: Defined as prevents daily activity.
c Grade 3 irritability/crying: Defined as lasting >3 hours or inconsolable.
d Grade 3 sleepiness: Defined as sleeps most of the time, hard to arouse.
e Grade 3 loss of appetite: Defined as missed >2 feeds/meals completely or refuses most feeds/meals.

Solicited local and systemic adverse reactions reported following administration of SPIKEVAX had a median duration of 2 to 4 days for participants 6 months through 23 months of age.

Solicited Adverse Reactions Among Participants with Evidence of Prior SARS-CoV-2 Infection

An assessment of reactogenicity among participants with evidence of prior SARS-CoV-2 infection (immunologic or virologic evidence of prior SARS-CoV-2 infection [defined as positive RT-PCR test and/or positive Elecsys immunoassay result at Day 1]) compared to those with no evidence of infection at baseline (negative RT-PCR test and negative Elecsys immunoassay result at Day 1) was conducted. In the 6 months through 23 months of age cohort, 6.8% of participants (vaccine=133, placebo=47) had evidence of prior SARS-CoV-2 infection at baseline. Fever (temperature ≥38°C) was reported in a greater proportion of baseline SARS-CoV-2 positive vaccine participants compared to baseline SARS-CoV-2 negative vaccine participants. There were no notable differences in other solicited adverse reactions.

Unsolicited Adverse Events

Participants were monitored for unsolicited adverse events for up to 28 days following each dose. Serious adverse events and medically attended adverse events were recorded for the entire study duration. In the blinded phase, among participants 6 months through 23 months of age who had received at least 1 dose of vaccine or placebo (vaccine=1,994, placebo=666), unsolicited adverse events that occurred within 28 days following each vaccination were reported by 44.3% of participants (n=883) who received SPIKEVAX and 42.5% of participants (n=283) who received placebo. In these analyses, 96.2% of study participants had at least 28 days of follow-up after Dose 2.

There were no notable patterns or numerical imbalances between treatment groups for specific categories of adverse events that would suggest a causal relationship to SPIKEVAX.

Serious Adverse Events

During the blinded part of the study, serious adverse events were reported by 1.6% of participants (n=31) who received vaccine and 0.9% of participants (n=6) who received placebo who were 6 months through 23 months of age. In the open-label phase, an additional 18 SPIKEVAX recipients reported serious adverse events. Two serious adverse events were considered related to vaccination: a 1-year-old female experienced serious adverse events of a Grade 3 fever 6 hours after Dose 1; and a febrile convulsion 1 day after Dose 1.

2-Dose Series (Monovalent Omicron XBB.1.5) in Vaccine-Naïve Infants and Children 6 Months Through 23 Months of Age (Study 6)

Safety data for a 2-dose series of SPIKEVAX (2023-2024 Formula) in individuals 6 months through 23 months of age were collected in an ongoing Phase 3 open-label clinical trial with multiple parts (Study 6, NCT05436834). The 2-dose series phase of the study conducted in the United States, Panama, and the Dominican Republic involved 399 participants 6 months through 23 months of age who were COVID-19 vaccine-naïve and received 2 doses of SPIKEVAX (2023-2024 Formula) (25 mcg mRNA). Overall, 52.1% were male, 47.9% were female, 84.7 % were Hispanic or Latino, 10.3% were White, 25.1% were Black or African American, 0.3% were American Indian or Alaska Native, 56.4% were other races, and 7.3% were Multiracial. In these analyses, the median duration of follow-up after Dose 2 was 59 days and 95.7% of study participants had at least 28 days of follow-up after Dose 2.

Solicited Adverse Reactions

Local and systemic adverse reactions and use of antipyretic medication were solicited in an electronic diary for 7 days following each injection (i.e., day of vaccination and the next 6 days) among participants receiving SPIKEVAX (2023-2024 Formula) with at least 1 documented dose. Events that persisted for more than 7 days were followed until resolution.

The reported number and percentage of the solicited local and systemic adverse reactions by dose in participants 6 months through 23 months of age are presented in Table 18.

Table 18: Number and Percentage of Participants With Solicited Local and Systemic Adverse Reactions Starting Within 7 Days* After Each Dose of SPIKEVAX (2023-2025 Formula) in Participants 6 Months Through 23 Months (Solicited Safety Set, Dose 1 and Dose 2)†
 | SPIKEVAX; (2023-2024 Formula)
 | Dose 1; (N=399); n (%) | Dose 2; (N=386); n (%)
Local Adverse Reactions
Pain | 55 (13.8) | 43 (11.1)
Pain, Grade 3a | 0 (0) | 2 (0.5)
Erythema (redness) ≥5 mm | 13 (3.3) | 12 (3.1)
Erythema (redness) Grade 3: >50 mm | 1 (0.3) | 2 (0.5)
Axillary (or groin) swelling/tenderness | 12 (3.0) | 10 (2.6)
Axillary (or groin) swelling/tenderness, Grade 3a | 0 (0) | 1 (0.3)
Swelling (hardness) ≥5 mm | 10 (2.5) | 5 (1.3)
Swelling (hardness) Grade 3: >50 mm | 0 (0) | 1 (0.3)
Systemic Adverse Reactions
Irritability/crying | 69 (17.3) | 50 (13.0)
Irritability/crying, Grade 3b | 1 (0.3) | 1 (0.3)
Loss of appetite | 48 (12.0) | 36 (9.3)
Loss of appetite, Grade 3d | 6 (1.5) | 7 (1.8)
Sleepiness | 41 (10.3) | 27 (7.0)
Sleepiness, Grade 3c | 2 (0.5) | 1 (0.3)
Fever ≥38.0°C / ≥100.4°F | 36 (9.0) | 44 (11.4)
Fever, Grade 3: 39.6° - 40.0°C / 103.2° - 104.0°F | 2 (0.5) | 3 (0.8)
Use of antipyretic or pain medication | 87 (21.8) | 88 (22.8)
* 7 days included day of vaccination and the subsequent 6 days. Events and use of antipyretic or pain medication were collected in the electronic diary (e-diary).
† Absence of rows for Grade 3 or Grade 4 adverse reactions indicates no events were reported.
a Grade 3 pain and axillary (or groin) swelling/tenderness: Defined as prevents daily activity.
b Grade 3 irritability/crying: Defined as lasting >3 hours or inconsolable.
c Grade 3 sleepiness: Defined as sleeps most of the time, hard to arouse.
d Grade 3 loss of appetite: Defined as missed >2 feeds/meals completely or refuses most feeds/meals.

Solicited local and systemic adverse reactions reported following administration of SPIKEVAX (2023-2024 Formula) had a median duration of 1 day for participants 6 months through 23 months of age.

Unsolicited Adverse Events

Participants were monitored for unsolicited adverse events for up to 28 days following each dose. Serious adverse events and medically attended adverse events were recorded for the entire study duration. Among participants 6 months through 23 months of age who had received at least 1 dose of vaccine (n=399), unsolicited adverse events that occurred within 28 days following each vaccination were reported by 51.9% of participants (n=207). In these analyses, 95.7% of study participants had at least 28 days of follow-up after Dose 2.

Serious Adverse Events

Through the end of this part of the study, serious adverse events were reported by 3.3% of participants 6 months through 23 months of age who received vaccine (n=13). None of the events were considered related to vaccine.

2-Dose Series (Bivalent Original and Omicron BA.1) in Vaccine-Naive Infants and Children 6 Months Through 23 Months of Age (Study 6)

Safety data for bivalent vaccine (Original and Omicron BA.1) in individuals 6 months through 5 years of age were collected in an ongoing Phase 3 open-label clinical trial with multiple parts. The study included a phase conducted in the United States involving 391 participants 6 months through 5 years of age who received at least one dose of bivalent vaccine (Original and Omicron BA.1) (25 mcg mRNA) (Study 6, NCT05436834). A safety analysis was conducted in 130 participants 6 months through 23 months of age who received SPIKEVAX. In this analysis, 50.0% were male, 50.0% were female, 10.0% were Hispanic or Latino, 63.1% were White, 26.9% were Black or African American, 3.1% were Asian, 0.8% were American Indian or Alaska Native, 0.8% were Native Hawaiian or Pacific Islander, 0.8% were other races, and 4.6% were Multiracial. The median duration of follow-up was 358 days after Dose 2 and 90.8% of study participants had at least 6 months of follow-up after Dose 2.

Unsolicited Adverse Events

Participants were monitored for unsolicited adverse events for up to 28 days following each dose. Serious adverse events and medically attended adverse events were recorded for the entire study duration. Among participants 6 months through 23 months of age who had received at least 1 dose of vaccine (n=130), unsolicited adverse events that occurred within 28 days following each vaccination were reported by 44.6% of participants (n=58). In these analyses, 95.4% of study participants had at least 28 days of follow-up after Dose 2. An 11-month-old female participant experienced a nonserious event of Henoch-Schönlein purpura 3 days after receiving Dose 2. There were no symptoms other than rash. The event was considered related to vaccine, and it resolved without treatment 8 days later.

Serious Adverse Events

Through the end of the open-label phase, serious adverse events were reported by 6.2% of participants 6 months through 23 months of age who received vaccine (n=8). None of the events were considered related to vaccine.

Single Dose (Bivalent Original and Omicron BA.1) in Vaccine-Experienced Infants and Children 6 Months Through 23 Months of Age (Study 6)

Safety data for a booster dose of bivalent vaccine (Original and Omicron BA.1) in individuals 6 months through 5 years of age were collected in an ongoing Phase 3 open-label clinical trial with multiple parts (Study 6, NCT05436834). The booster phase of the study conducted in the United States involved 539 participants 6 months through 5 years of age who received a booster dose of bivalent vaccine (Original and Omicron BA.1) (10 mcg mRNA) at least 4 months (range 4-10; median 7 months) after the second dose of the SPIKEVAX primary series. A safety analysis was conducted in 114 participants 6 months through 23 months of age. In this analysis, 45.6% were male, 54.4% were female, 6.1% were Hispanic or Latino, 79.8% were White, 0.9% were Black or African American, 5.3% were Asian, and 13.2% were Multiracial. The median duration of follow-up after the booster dose was 183 days and 97.4% of study participants had at least 6 months of follow-up.

Solicited Adverse Reactions

Solicited local and systemic adverse reactions in participants 6 months through 23 months of age (n=114) starting within 7 days after administration of a booster dose included irritability/crying (54.9%), pain at the injection site (32.5%), loss of appetite (27.4%), sleepiness (17.7%), erythema at the injection site (11.4%), fever (11.4%), swelling at the injection site (8.8%), and axillary (or groin) swelling/tenderness (5.3%).

No Grade 4 adverse reactions were reported. In participants 6 months through 23 months of age who received a booster dose, the median duration of solicited local and systemic adverse reactions was 1 to 3 days.

Unsolicited Adverse Events

Participants were monitored for unsolicited adverse events for up to 28 days following the booster dose. Serious adverse events and medically attended adverse events were recorded for the entire study duration.

Among participants 6 months through 23 months of age who had a booster dose of bivalent vaccine (Original and Omicron BA.1), unsolicited adverse events that occurred within 28 days following vaccination were reported by 29.8% of participants (n=34). In these analyses, 99.1% of study participants had at least 28 days of follow-up after the booster dose.

Serious Adverse Events

Through the end of the booster phase of the study, serious adverse events were reported by 4.4% of participants 6 months through 23 months of age who received a booster dose (n=5). None of the events were considered causally related to the vaccine.

Single Dose (Bivalent Original and Omicron BA.1) in Vaccine-Experienced Infants and Children 6 Months Through 23 Months of Age (Study 4)

Safety data for a booster dose of bivalent vaccine (Original and Omicron BA.1) were collected in participants 6 months through 5 years of age in a Phase 2/3 clinical trial with multiple parts. The open-label booster portion of the study involved 1,252 participants 6 months through 23 months of age who received a booster dose of bivalent vaccine (Original and Omicron BA.1) (10 mcg mRNA) at least 6 months (range 2-20 months; median 11 months) after the second dose of the SPIKEVAX primary series (Study 4, NCT04796896). Safety data included medically attended adverse events and serious adverse events collected for the duration of the study. In this analysis, 50.3% were male, 49.7% were female, 12.2% were Hispanic or Latino, 78.6% were White, 3.7% were African American, 3.8% were Asian, 0.3% were American Indian or Alaska Native, 1.2% were other races, and 11.9% were Multiracial. The median duration of follow-up for safety after the booster dose was 184 days and 96.7% had at least 6 months of follow-up.

Through the end of this part of the study, serious adverse events were reported by 0.8% of participants 6 months through 23 months of age who received a booster dose (n=10). None of the events were considered causally related to the vaccine.

6.2 Postmarketing Experience

The following adverse reactions have been identified during postmarketing use of SPIKEVAX, Moderna COVID-19 Vaccine, or Moderna COVID-19 Vaccine, Bivalent. Because these reactions are reported voluntarily, it is not always possible to reliably estimate their frequency or establish a causal relationship to vaccine exposure.

Cardiac Disorders: myocarditis, pericarditis
Immune System Disorders: anaphylaxis, urticaria
Nervous System Disorders: syncope, febrile seizures

Cardiovascular Outcomes in Patients Diagnosed with mRNA COVID-19 Vaccine-associated Myocarditis

In a longitudinal retrospective observational cohort study across 38 hospitals in the U.S., information on cardiovascular outcomes was collected on 333 patients 5 years through 29 years of age who had been diagnosed with COVID-19 vaccine-associated myocarditis. Among these patients, 322 were confirmed to have received an mRNA COVID-19 vaccine encoding the S glycoprotein of the Original SARS-CoV-2. Of 331 patients, 278 had onset of symptoms following the second dose of a primary series, 33 following the first dose of a primary series, and 20 following a first booster dose.^1

Among 307 patients who had been diagnosed with COVID-19 vaccine-associated myocarditis for whom follow-up information was available, 89 reported cardiac symptoms at a median follow-up of 91 days (interquartile range 25-186 days) post-vaccination.^1

Initial gadolinium-enhanced cardiac magnetic resonance imaging (CMR) was performed on 216 patients, of whom 177 had late gadolinium enhancement (LGE), a marker of myocardial injury. Among 161 patients who had LGE on initial CMR and who had a follow-up gadolinium-enhanced CMR at a median follow-up of 159 days (interquartile range 78-253 days), 98 had persistence of LGE. Overall, the severity of LGE decreased during follow-up. The clinical and prognostic significance of these CMR findings is not known.^1

Limitations of this study include potential selection bias towards patients with more severe myocarditis who are more likely to be hospitalized and have CMR, variability in diagnostic testing, and variability in follow-up.^1

8 USE IN SPECIFIC POPULATIONS

8.1 Pregnancy

Risk Summary

All pregnancies have a risk of birth defect, loss, or other adverse outcomes. In the U.S. general population, the estimated background risk of major birth defects and miscarriage in clinically recognized pregnancies is 2% to 4% and 15% to 20%, respectively. Available data on SPIKEVAX administered to pregnant women are insufficient to inform vaccine-associated risks in pregnancy.

A developmental toxicity study was performed in female rats administered the equivalent of a single primary series dose of SPIKEVAX twice prior to mating and twice during gestation. The study revealed no evidence of harm to the fetus due to the vaccine (see Animal Data).

Data

Animal Data

In a developmental toxicity study, 0.2 mL of a vaccine formulation containing the same quantity of nucleoside-modified messenger ribonucleic acid (mRNA) (100 mcg) and other ingredients included in a single primary series dose of SPIKEVAX for individuals 12 years of age and older was administered to female rats by the intramuscular route on four occasions: 28 and 14 days prior to mating, and on gestation days 1 and 13. No vaccine-related fetal malformations or variations and no adverse effect on postnatal development were observed in the study.

Clinical Considerations

Disease-Associated Maternal and/or Embryo/Fetal Risk

Pregnant individuals infected with SARS-CoV-2 are at increased risk of severe COVID-19 compared with non-pregnant individuals.

8.2 Lactation

Risk Summary

It is not known whether SPIKEVAX is excreted in human milk. Data are not available to assess the effects of SPIKEVAX on the breastfed infant or on milk production/excretion. The developmental and health benefits of breastfeeding should be considered along with the mother’s clinical need for SPIKEVAX and any potential adverse effects on the breastfed infant from SPIKEVAX or from the underlying maternal condition. For preventive vaccines, the underlying maternal condition is susceptibility to disease prevented by the vaccine.

8.4 Pediatric Use

Safety and effectiveness of SPIKEVAX in individuals 6 months through 17 years of age with at least one high risk factor for severe COVID-19 outcomes is based on safety and effectiveness data in this age group and in adults [see Adverse Reactions (6) and Clinical Studies (14)]. Safety and effectiveness of SPIKEVAX have not been established in individuals less than 6 months of age.

In addition to the Centers for Disease Control and Prevention published list of medical conditions which place individuals at higher risk of experiencing severe outcomes of COVID-19 (https://www.cdc.gov/covid/hcp/clinical-care/underlying-conditions.html), prematurity has been associated with COVID-19-related hospitalizations in children 6 months through 23 months of age.^2

8.5 Geriatric Use

Clinical studies of SPIKEVAX and Moderna COVID-19 Vaccine, Bivalent included approximately 7,800 participants 65 years of age and older and 1,400 participants 75 years of age and older [see Adverse Reactions (6.1) and Clinical Studies (14.1)].

Some local and systemic adverse reactions were reported in a lower proportion of participants 65 years of age and older compared to participants 18 years through 64 years of age [see Adverse Reactions (6.1)].

Vaccine effectiveness was similar between participants 65 years of age and older and participants 18 years through 64 years [see Clinical Studies (14.1)].

8.6 Immunocompromised Individuals

The Centers for Disease Control and Prevention has published considerations related to COVID-19 vaccination for individuals who are moderately to severely immunocompromised (https://www.cdc.gov/vaccines/covid-19/clinical-considerations/covid-19-vaccines-us.html).

11 DESCRIPTION

SPIKEVAX (COVID-19 Vaccine, mRNA) is a sterile white to off-white injectable suspension for intramuscular use.

Each 0.5 mL dose of SPIKEVAX (2025-2026 Formula) contains 50 mcg nucleoside-modified messenger RNA (mRNA) encoding the pre-fusion stabilized Spike glycoprotein (S) of the SARS-CoV-2 Omicron variant sublineage LP.8.1. Each dose also contains the following ingredients: a total lipid content of 1.01 mg (SM-102, polyethylene glycol [PEG] 2000 dimyristoyl glycerol [DMG], cholesterol, and 1,2-distearoyl-sn-glycero-3-phosphocholine [DSPC]), 0.25 mg tromethamine, 1.2 mg tromethamine hydrochloride, 0.021 mg acetic acid, 0.10 mg sodium acetate trihydrate, and 43.5 mg sucrose.

Each 0.25 mL dose of SPIKEVAX (2025-2026 Formula) contains 25 mcg nucleoside-modified messenger RNA (mRNA) encoding the pre-fusion stabilized Spike glycoprotein (S) of the SARS-CoV-2 Omicron variant sublineage LP.8.1. Each dose also contains the following ingredients: a total lipid content of 0.50 mg (SM-102, polyethylene glycol [PEG] 2000 dimyristoyl glycerol [DMG], cholesterol, and 1,2-distearoyl-sn-glycero-3-phosphocholine [DSPC]), 0.13 mg tromethamine, 0.62 mg tromethamine hydrochloride, 0.011 mg acetic acid, 0.049 mg sodium acetate trihydrate, and 21.8 mg sucrose.

SPIKEVAX does not contain a preservative.

The rubber tip cap and plunger used for the single-dose syringes are not made with natural rubber latex.

12 CLINICAL PHARMACOLOGY

12.1 Mechanism of Action

The nucleoside-modified mRNA in SPIKEVAX is formulated in lipid particles, which enable delivery of the nucleoside-modified mRNA into host cells to allow expression of the SARS-CoV-2 S antigen. The vaccine elicits an immune response to the S antigen, which protects against COVID-19.

13 NONCLINICAL TOXICOLOGY

13.1 Carcinogenesis, Mutagenesis, Impairment of Fertility

SPIKEVAX has not been evaluated for carcinogenic, mutagenic potential, or impairment of male fertility in animals. A developmental toxicity study was conducted in female rats that received a vaccine formulation containing nucleoside-modified messenger ribonucleic acid (mRNA) (100 mcg) and other ingredients included in a single human dose of SPIKEVAX. No impact on female fertility was reported (see Use in Specific Populations [8.1]).

14 CLINICAL STUDIES

14.1 Adults 18 Years of Age and Older

Efficacy of 2-Dose Series (Original Monovalent) in Vaccine-Naïve Adults

Study 1 was a Phase 3 clinical trial with multiple parts. The randomized, placebo-controlled, observer-blind phase evaluated the efficacy, safety, and immunogenicity of SPIKEVAX in participants 18 years of age and older in the United States. Randomization was stratified by age and health risk: 18 to <65 years of age without comorbidities (not at risk for progression to severe COVID-19), 18 to <65 years of age with comorbidities (at risk for progression to severe COVID-19), and 65 years of age and older with or without comorbidities. Participants who were immunocompromised and those with a known history of SARS-CoV-2 infection were excluded from the study. Participants with no known history of SARS-CoV-2 infection but with positive laboratory results indicative of infection at study entry were included. The study allowed for the inclusion of participants with stable pre-existing medical conditions, defined as disease not requiring significant change in therapy or hospitalization for worsening disease during the 3 months before enrollment, as well as participants with stable human immunodeficiency virus (HIV) infection. A total of 30,415 participants were randomized equally to receive 2 doses of SPIKEVAX or saline placebo 1 month apart. Participants were followed for efficacy and safety until 2 years after the second dose.

The primary efficacy analysis population (referred to as the Per-Protocol Set) included 28,451 participants who received two doses (at 0 and 1 month) of either SPIKEVAX (100 mcg mRNA per dose; n=14,287) or placebo (n=14,164), and had a negative baseline SARS-CoV-2 status. In the Per-Protocol Set, 47.5% of participants were female, 19.7% were Hispanic or Latino; 79.7% were White, 9.7% were African American, 4.7% were Asian, and 2.0% were other races. The median age of participants was 53 years (range 18-95) and 25.4% of participants were 65 years of age and older. Of the study participants in the Per-Protocol Set, 22.8% were at increased risk of severe COVID-19 due to at least one pre-existing medical condition (chronic lung disease, significant cardiac disease, severe obesity, diabetes, liver disease, or HIV infection) regardless of age. There were no notable differences in demographics or pre-existing medical conditions between participants who received SPIKEVAX and those who received placebo.

The population for the vaccine efficacy analysis included participants 18 years of age and older who were enrolled from July 27, 2020, and followed for the development of COVID-19 through the data cutoff of March 26, 2021, or the Participant Decision Visit for treatment unblinding, whichever was earlier. The median length of follow-up for participants in the blinded placebo-controlled phase of the study was 4 months following Dose 2.

COVID-19 was defined based on the following criteria: The participant must have experienced at least two of the following systemic symptoms: fever (≥38ºC / ≥100.4ºF), chills, myalgia, headache, sore throat, new olfactory and taste disorder(s); or the participant must have experienced at least one of the following respiratory signs/symptoms: cough, shortness of breath or difficulty breathing, or clinical or radiographical evidence of pneumonia; and the participant must have at least one NP swab, nasal swab, or saliva sample (or respiratory sample, if hospitalized) positive for SARS-CoV-2 by RT-PCR. COVID-19 cases were adjudicated by a Clinical Adjudication Committee.

There were 55 COVID-19 cases in the SPIKEVAX group and 744 cases in the placebo group, with a vaccine efficacy of 93.2% (95% confidence interval of 91.0% to 94.8%) (Table 19).

SARS-CoV-2 identified in the majority of COVID-19 cases in this study were sequenced to be the B.1.2 variant. Additional SARS-CoV-2 variants identified in this study included B.1.427/B.1.429 (Epsilon), P.1 (Gamma), and P.2 (Zeta). Representation of identified variants among cases in the vaccine versus placebo recipients did not suggest decreased vaccine effectiveness against these variants.

Table 19: Vaccine Efficacy Against COVID-19* in Participants 18 Years of Age and Older Starting 14 Days After Dose 2 per Adjudication Committee Assessments – Per-Protocol Set
Age; Subgroup; (Years) | SPIKEVAXa |  |  | Placebob |  |  | % Vaccine Efficacy (95% CI)c
Age; Subgroup; (Years) | Participants (N) | COVID-19; Cases; (n) | Incidence Rate of COVID-19; per 1,000 Person-Years | Participants; (N) | COVID-19; Cases; (n) | Incidence Rate of COVID-19; per 1,000 Person-Years | % Vaccine Efficacy (95% CI)c
All participants | 14,287 | 55 | 9.6 | 14,164 | 744 | 136.6 | 93.2; (91.0, 94.8)
18 to <65 | 10,661 | 46 | 10.7 | 10,569 | 644 | 159.0 | 93.4; (91.1, 95.1)
≥65 | 3,626 | 9 | 6.2 | 3,595 | 100 | 71.7 | 91.5; (83.2, 95.7)
* COVID-19: symptomatic COVID-19 requiring positive RT-PCR result and at least two systemic symptoms (fever [≥38ºC /
≥100.4ºF], chills, myalgia, headache, sore throat, new olfactory and taste disorder[s]) or one respiratory symptom (cough, shortness of breath or difficulty breathing, or clinical or radiographical evidence of pneumonia). Cases starting 14 days after Dose 2.
a SPIKEVAX dosing was a two-dose series (100 mcg mRNA per dose) 1 month apart.
b Placebo dosing was a two-dose series (saline solution) 1 month apart.
c VE and 95% CI from the stratified Cox proportional hazard model.

Severe COVID-19 was defined based on confirmed COVID-19 as per the primary efficacy endpoint case definition, plus any of the following: Clinical signs indicative of severe systemic illness, respiratory rate ≥30 per minute, heart rate ≥125 beats per minute, SpO2 ≤93% on room air at sea level or PaO2/FIO2 <300 mm Hg; or respiratory failure or ARDS (defined as needing high-flow oxygen, non-invasive or mechanical ventilation, or ECMO), evidence of shock (systolic blood pressure <90 mmHg, diastolic BP <60 mmHg or requiring vasopressors); or significant acute renal, hepatic, or neurologic dysfunction; or admission to an intensive care unit or death.

Among all participants in the Per-Protocol Set analysis, which included COVID-19 cases confirmed by an adjudication committee, 2 cases of severe COVID-19 were reported in the SPIKEVAX group compared with 106 cases reported in the placebo group, with a vaccine efficacy of 98.2% (95% confidence interval of 92.8% to 99.6%) (Table 20).

Table 20: Vaccine Efficacy Against Severe COVID-19* in Participants 18 Years of Age and Older Starting 14 Days After Dose 2 per Adjudication Committee Assessments – Per-Protocol Set
SPIKEVAXa |  |  | Placebob |  |  | % Vaccine Efficacy (95% CI)c
Participants; (N) | Severe COVID-19; Cases (n) | Incidence Rate of COVID-19; per 1,000 Person-Years | Participants; (N) | Severe COVID-19; Cases (n) | Incidence Rate of COVID-19; per 1,000 Person-Years | % Vaccine Efficacy (95% CI)c
14,287 | 2 | 0.3 | 14,164 | 106 | 19.1 | 98.2; (92.8, 99.6)
* Severe COVID-19: symptomatic COVID-19 requiring positive RT-PCR result and at least two systemic symptoms or one respiratory symptom, plus any of the following: Clinical signs indicative of severe systemic illness, respiratory rate ≥30 per minute, heart rate ≥125 beats per minute, SpO2 ≤93% on room air at sea level or PaO2/FIO2 <300 mm Hg; or respiratory failure or ARDS (defined as needing high-flow oxygen, non-invasive or mechanical ventilation, or ECMO), evidence of shock (systolic blood pressure <90 mmHg, diastolic BP <60 mmHg or requiring vasopressors); or significant acute renal, hepatic, or neurologic dysfunction; or admission to an intensive care unit or death. Cases starting 14 days after Dose 2.
a SPIKEVAX dosing was a two-dose series (100 mcg mRNA per dose) 1 month apart.
b Placebo dosing was a two-dose series (saline solution) 1 month apart.
c VE and 95% CI from the stratified Cox proportional hazard model.

In an exploratory analysis, occurrence of asymptomatic SARS-CoV-2 infection was assessed among participants in the Per-Protocol Set (enrolled from July 27, 2020, and followed maximally through March 26, 2021). Asymptomatic SARS-CoV-2 infection was defined as having a positive scheduled serology test based on binding antibody against SARS-CoV-2 nucleocapsid protein as measured by the Roche Elecsys immunoassay (N-serology) and/or a positive RT-PCR test for SARS-CoV-2, in the absence of any reported COVID-19 symptoms included as part of the primary efficacy endpoint case definition (described above) or symptoms included in the secondary COVID-19 endpoint case definition (fever >38°C / ≥100.4°F, chills, cough, shortness of breath or difficulty breathing, fatigue, muscle aches, body aches, headache, new loss of taste or smell, sore throat, congestion or runny nose, nausea, vomiting, or diarrhea) at any time during the study. To assess for asymptomatic infection starting 14 days after Dose 2, all participants had scheduled blood draws for N-serology collected at the 1-month post-Dose 2 visit and the 6-month post-Dose 2 visit (if still blinded to treatment arm), and scheduled N-serology and nasopharyngeal swab for RT-PCR collection at the Participant Decision Visit for treatment unblinding.

In the Per-Protocol Set, 14,287 participants in the SPIKEVAX group and 14,164 participants in the placebo group had N-serology and/or RT-PCR results available from one or more of the pre-specified timepoints listed above. Among these participants, there were 180 cases of asymptomatic SARS-CoV-2 infection in the SPIKEVAX group compared with 399 cases in the placebo group. Limitations of this analysis include the infrequently scheduled assessments for serology and PCR testing, which may not have captured all cases of asymptomatic infections which occurred during the study.

Immunogenicity of a Single Dose (Original Monovalent) in Vaccine-Experienced Adults

Effectiveness of a booster dose of SPIKEVAX was based on assessment of neutralizing antibody geometric mean concentration (GMC) against a pseudovirus expressing the original SARS-CoV-2 Spike protein (D614G). Immunogenicity analyses compared the GMC following the booster dose to the GMC following the primary series.

In the open-label booster dose phase of Study 1, the primary immunogenicity analysis population included 682 participants 18 years of age and older who received a single booster dose of SPIKEVAX (50 mcg mRNA) at least 6 months after completion of the primary series of SPIKEVAX (two doses of 100 mcg mRNA 1 month apart). Participants had no serologic or virologic evidence of SARS-CoV-2 infection prior to the first primary series dose and prior to the booster dose. Among participants assessed for immunogenicity, the median age at the time of booster dose was 59 years (range 19-87); 61.3% of participants were 18 years through 64 years of age, 38.7% were 65 years of age and older, 52.9% were male, 47.1% were female, 30.4% were Hispanic or Latino; 70.8% were White, 19.6% were African American, 2.5% were Asian, 1.3% were American Indian or Alaska Native, 0.4% were Native Hawaiian or Pacific Islander, 3.1% were other races, and 1.3% were Multiracial.

The primary immunogenicity analyses of the GMC ratio and difference in seroresponse rates following the booster dose compared to after the primary series met the pre-defined success criteria. Seroresponse for a participant was defined as achieving a ≥4-fold rise of neutralizing antibody concentration from baseline (before the first dose of the primary series). These analyses are summarized in Table 21.

Table 21: Comparison of Geometric Mean Concentration and Seroresponse Rate Against a Pseudovirus Expressing the Original SARS-CoV-2 Spike Protein (D614G) at 28 Days After a Booster Dose of SPIKEVAX vs 28 Days After Completion of the Primary Series of SPIKEVAX, Participants 18 Years of Age and Older, Per-Protocol Immunogenicity Set – Pre-booster SARS-CoV-2 Negative*
Booster Dosea; N=636; GMC; (95% CI)b | Primary Seriesc; N=680; GMC; (95% CI)b | GMC Ratio; (Study 1 Booster Dose/; Study 1 Primary Series)d | Met Success Criteria
7759.3; (7258.7, 8294.4) | 1111.3; (1041.7, 1185.5) | 7.0; (6.5, 7.5) | Yese
Booster Dosea; Seroresponsed; N1=634; %; (95% CI)f | Primary Seriesd; Seroresponsed; N1=680; %; (95% CI)f | Difference in Seroresponse Rate; (Study 1 Booster Dose-; Study 1 Primary Series); %; (95% CI)g | Met Success Criterion
100; (99.4, 100.0) | 98.8; (97.7, 99.5) | 0.9; (0.1, 1.8) | Yesh
N=Number of subjects with non-missing data at the corresponding timepoint.
N1=Number of participants with non-missing data at pre-vaccination baseline and 28 days post-Booster Dose in the booster dose group or 28 days post-Dose 2 in the primary series group.
* Per-Protocol Immunogenicity Set – Pre-booster SARS-CoV-2 Negative included all subjects who had both baseline (or Booster Dose Day 1) and post-vaccination immunogenicity samples, did not have evidence of prior SARS-CoV-2 infection at baseline and Booster Dose Day 1, did not have a major protocol deviation that impacted immune response, and had post-injection immunogenicity assessment at timepoint of primary interest (Booster Dose Day 29 for booster dose and Day 57 for primary series).
a SPIKEVAX dosing was a single booster dose (50 mcg mRNA).
b 95% CI is calculated based on the t-distribution of the log-transformed values for GMC, then back transformed to the original scale for presentation.
c SPIKEVAX dosing was a two-dose series (100 mcg mRNA per dose) 1 month apart.
d The log-transformed antibody levels are analyzed using paired t-test method with the group variable and 95% CI is calculated based on the t-distribution of the mean of paired difference in the log-transformed values, then back transformed to the original scale for presentation.
e Success criteria are met if the lower limit of the 2-sided 95% CI for the GMC ratio is ≥0.67 and the point estimate of the GMC ratio is >1.0.
f Seroresponse at a subject level is defined as a change from below the lowest limit of quantification (LLOQ) to equal or above 4 x LLOQ, or at least a 4-fold rise if baseline (Pre-vaccination [Dose 1]) is equal to or above the LLOQ. 95% CI is calculated using the Clopper-Pearson method.
g Difference in seroresponse rate and 95% CI are calculated using adjusted Wald method for the paired binary data. The number of subjects included in the comparison could be different from N1.
h Success criterion is met if the lower limit of the 2-sided 95% CI for the percentage difference is >-10%.
Note: Geometric mean concentration (GMC) was determined using a SARS-CoV-2 Spike-Pseudotyped Virus Neutralization Assay. Quantification of SARS-CoV-2 neutralizing antibodies utilizes SARS-CoV-2 Reporter Virus Particles which express GFP for quantitative measurement of infection by counting the number of green fluorescent cells (assay readout [count] is Foci Forming Units [FFUs]). The serum antibody concentration (Ab[C]) of the neutralizing antibodies was determined by interpolating the mean of the replicate FFU values off the fitted reference standard curve (AU/mL).

A descriptive analysis evaluated seroresponse rates using pre-booster neutralizing antibody concentration. The booster dose seroresponse rate, with seroresponse defined as at least a 4-fold rise relative to the pre-booster concentration, was 98.4%. The difference in seroresponse rates in this post-hoc analysis was -0.8% (95% CI: -2.1%, 0.5%).

Immunogenicity of a Single Dose (Bivalent Original and Omicron BA.4/BA.5) in Vaccine-Experienced Adults

Study 5 was a Phase 2/3 open-label study with multiple parts which evaluated the immunogenicity of a second booster dose of Moderna COVID-19 Vaccine, Bivalent (50 mcg mRNA) compared to a second booster dose of SPIKEVAX (50 mcg mRNA) when administered to participants 18 years of age and older who had previously received a primary series and a first booster dose with SPIKEVAX at least 3 months prior. The primary immunogenicity analysis population included 209 participants who received a booster dose of Moderna COVID-19 Vaccine, Bivalent and 259 participants who received a booster dose of SPIKEVAX. Participants included in the analysis population had no serologic or virologic evidence of SARS-CoV-2 infection prior to the second booster dose.

Among participants assessed for immunogenicity for the Moderna COVID-19 Vaccine, Bivalent group, the median age was 51 years (range 21-84); 74.6% of participants were 18 years through 64 years of age, 25.4% were 65 years of age and older, 35.4% were male, 64.6% were female, 9.6% were Hispanic or Latino, 89.0% were White, 5.3% were African American, 3.3% were Asian, 0.5% were American Indian or Alaska Native, 0.5% were other races, and 1.0% were Multiracial. Among participants assessed for immunogenicity for the SPIKEVAX group, the median age was 63 years (range 21-96); 53.7% of participants were 18 years through 64 years of age, 46.3% were 65 years of age and older, 48.3% of participants were male, 51.7% were female, 8.5% were Hispanic or Latino, 90.0% were White, 4.2% were African American, 4.2% were Asian, and 0.4% were other races. The median time between the first booster dose and the second booster dose was 288 days in the Moderna COVID-19 Vaccine, Bivalent group and 133 days in the SPIKEVAX group.

In Study 5, the neutralizing antibody titers (50% inhibitory dose [ID50]) against a pseudovirus expressing the original SARS-CoV-2 Spike protein (D614G) and a pseudovirus expressing the Omicron BA.4/BA.5 Spike protein were evaluated. Primary immunogenicity analyses compared the ID50 GMTs and seroresponse rates 28 days following a second booster dose with Moderna COVID-19 Vaccine, Bivalent to those following a second booster dose with SPIKEVAX. Analyses of GMTs met predefined success criteria for superiority against Omicron BA.4/BA.5 and noninferiority against the Original strain. The analysis of seroresponse against Omicron BA.4/BA.5 met the criterion for noninferiority: Lower limit of the 2-sided 95% CI for the percentage difference in seroresponse rate (Moderna COVID-19 Vaccine, Bivalent minus SPIKEVAX) >-10%. Table 22 presents the analyses of ID50 GMTs. Table 23 presents the analyses of differences in seroresponse rates (the proportion achieving a ≥4-fold rise in ID50 from pre-second booster) against both the Original strain and Omicron BA.4/BA.5.

Table 22: Neutralizing Antibody Titers (ID50) at 28 Days After a Second Booster Dose with Moderna COVID-19 Vaccine, Bivalent or SPIKEVAX in Participants 18 Years and Older – Per-Protocol Immunogenicity SARS-CoV-2 Negative Set*
Assaya | Moderna COVID-19 Vaccine, Bivalentb; N=209; GMTc; (95% CI) | SPIKEVAXd; N=259; GMTc; (95% CI) | GMT Ratioc; (Moderna COVID-19 Vaccine, Bivalent / SPIKEVAX); (95% CI)c | Met Success Criteria
Omicron BA.4/BA.5 | 2747.3; (2399.2, 3145.9) | 436.7; (389.1, 490.0) | 6.3; (5.3, 7.5) | Yese
Original SARS-CoV-2 (D614G) | 9555.8; (8593.6, 10625.7) | 4882.2; (4457.7, 5347.1) | 2.0; (1.7, 2.3) | Yesf
* Per-Protocol Immunogenicity SARS-CoV-2 Negative Set included all subjects who received the planned dose of study vaccine per schedule, had pre-booster and Day 29 neutralizing antibody data, had no major protocol deviations that impact key or critical data, had no history of HIV infection, and had no serologic or virologic evidence of SARS-CoV-2 infection prior to the second booster dose.
a SARS-CoV-2 50% inhibitory dose (ID50) neutralization titers were determined using a SARS-CoV-2 Spike-Pseudotyped Virus Neutralization Assay. Quantification of SARS-CoV-2 neutralizing antibodies utilizes lentivirus particles expressing SARS-CoV-2 Spike protein on their surface and contains a firefly luciferase (Luc) reporter gene for quantitative measurements of infection by relative luminescence units (RLU). Neutralization is measured as the serum dilution at which RLU is reduced by 50% (ID50) relative to mean RLU in virus control wells but after subtraction of mean RLU in cell control wells.
b Moderna COVID-19 Vaccine, Bivalent dosing was a single booster (50 mcg mRNA).
c The log-transformed antibody levels are analyzed using an analysis of covariance (ANCOVA) model with the treatment variable as fixed effect, adjusting for age group (<65, ≥65 years) and pre-booster antibody titer level (in log 10 scale). The treatment variable corresponds to each individual study arm dose. The resulted least square (LS) means, difference of LS means, and confidence intervals are back transformed to the original scale for presentation.
d SPIKEVAX dosing was a single booster dose (50 mcg mRNA).
e Superiority is declared if the lower limit of the 2-sided 95% CI for the GMT ratio is >1.
f Noninferiority is declared if the lower limit of the 2-sided 95% CI for the GMT ratio is >0.667.
Note: Antibody values < the lower limit of quantitation (LLOQ) are replaced by 0.5 × LLOQ. Values > the upper limit of quantitation (ULOQ) are replaced by the ULOQ if actual values are not available.

Table 23: Analyses of Seroresponse Rates at 28 Days After a Second Booster Dose with Moderna COVID-19 Vaccine, Bivalent or SPIKEVAX in Participants 18 Years and Older – Per-Protocol Immunogenicity SARS-CoV-2 Negative Set*
Assay | Moderna COVID-19 Vaccine, Bivalenta; Seroresponseb; N=209; %c; (95% CI)d | SPIKEVAXe; Seroresponseb; N=259; %c; (95% CI)d | Difference in Seroresponse Rate; (Moderna COVID-19 Vaccine, Bivalent-SPIKEVAX); % (95% CI)f
Omicron BA.4/BA.5 | 90.9; (86.2, 94.4) | 37.8; (31.9, 44.0) | 53.9 (46.7, 61.2)
Original SARS-CoV-2 (D614G) | 80.4; (74.3, 85.5) | 42.9; (36.7, 49.1) | 37.3 (29.0, 45.6)
N=number of participants with non-missing data at corresponding timepoint.
* Per-Protocol Immunogenicity SARS-CoV-2 Negative Set included all subjects who received the planned dose of study vaccine per schedule, had pre-booster and Day 29 neutralizing antibody data, had no major protocol deviations that impact key or critical data, had no history of HIV infection, and had no serologic or virologic evidence of SARS-CoV-2 infection prior to the second booster dose.
a Moderna COVID-19 Vaccine, Bivalent dosing was a single booster dose (50 mcg mRNA).
b For assessment of seroresponse rates, baseline was pre-second booster dose; seroresponse was defined as a change from below the LLOQ to equal or above 4 x LLOQ if participant pre-second booster dose baseline was below the LLOQ, or at least a 4-fold rise if baseline is equal to or above the LLOQ.
c Proportion of participants who met seroresponse definition.
d 95% CI is calculated using the Clopper-Pearson method.
e SPIKEVAX dosing was a single booster dose (50 mcg mRNA).
f Common risk difference and 95% CI is calculated using the stratified Miettinen-Nurminen method to adjust for age group (<65, ≥65 years).

In subgroup analyses, neutralizing antibodies against a pseudovirus expressing the original SARS-CoV-2 Spike protein (D614G) and a pseudovirus expressing the Omicron BA.4/BA.5 Spike protein were similar in participants 65 years of age and older compared to participants 18 years through 64 years of age. The seroresponse rate observed at Day 29 was similar between age groups.

14.2 Adolescents 12 Years Through 17 Years of Age

Effectiveness of 2-Dose Series (Original Monovalent) in Vaccine-Naïve Adolescents

Study 3 was a Phase 3 clinical trial with multiple parts. The randomized, placebo-controlled, observer-blind phase evaluated the safety, reactogenicity, and effectiveness of SPIKEVAX in participants ages 12 years through 17 years in the United States. Participants with a known history of SARS-CoV-2 infection were excluded from the study. A total of 3,733 participants were randomized 2:1 to receive 2 doses of SPIKEVAX (100 mcg mRNA per dose) or saline placebo 1 month apart. Among participants assessed for immunogenicity, 52.4% of participants were male, 47.6% were female, 7.6% were Hispanic or Latino; 83.5% were White, 1.2% were African American, 4.4% were Asian, 0.3% were Native Hawaiian or Pacific Islander, 2.1% were other races, and 5.6% were Multiracial.

Effectiveness in individuals 12 years through 17 years of age is based on a comparison of immune responses in this age group to adults 18 years through 25 years of age.

In Study 3, an analysis was conducted of SARS-CoV-2 50% neutralizing titers and seroresponse rates 28 days after Dose 2 in a subset of participants 12 years through 17 years of age in Study 3 and participants 18 years through 25 years of age in Study 1 who had no immunologic or virologic evidence of prior SARS-CoV-2 at baseline. Noninferior immune responses as assessed by geometric mean 50% neutralizing titers and seroresponse rates were demonstrated in a comparison of participants 12 years through 17 years of age to participants 18 years through 25 years of age (Table 24).

Table 24: Comparison of Geometric Mean Titer Ratio and Seroresponse Rate Against a Pseudovirus Expressing the Original SARS-CoV-2 Spike Protein (D614G) at 28 Days After Completion of the Primary Series of SPIKEVAX,* Participants 12 Years Through 17 Years of Age vs Participants 18 Years Through 25 Years of Age – Per-Protocol Immunogenicity Subset
12 Years Through 17 Years; N=340 | 18 Years Through 25 Years; N=295 | 12 Years Through 17 Years/; 18 Years Through 25 Years
GMT; (95% CI)a | GMT; (95% CI)a | GMT Ratio; (95% CI)b | Met; Success Criteriac
1401.7; (1276.2, 1539.5) | 1299.9; (1175.4, 1437.5) | 1.1; (0.9, 1.2) | Yes
Seroresponse; %d; (95% CI)e | Seroresponse; %d; (95% CI)e | Difference in Seroresponse Rate; %; (95% CI)f | Met; Success Criteriac
98.8; (97.0, 99.7) | 99.0; (97.1, 99.8) | -0.2; (-2.1, 1.9) | Yes
N=Number of subjects with non-missing data at the corresponding timepoint.
GMT=Geometric mean titers
* SPIKEVAX dosing was a two-dose series (100 mcg mRNA per dose) 1 month apart.
a Antibody values reported as below the lower limit of quantification (LLOQ) are replaced by 0.5 x LLOQ. Values greater than the upper limit of quantification (ULOQ) are replaced by the ULOQ if actual values are not available.
b The log-transformed antibody levels are analyzed using an analysis of covariance (ANCOVA) model with the group variable (adolescents in Study 3 and young adults in Study 1) as fixed effect. The resulted LS means, difference of LS means, and 95% CI are back transformed to the original scale for presentation.
c Noninferiority is declared if the lower bound of the 2-sided 95% CI for the GMT Ratio is greater than 0.67, with a point estimate of >0.8 and the lower bound of the 2-sided 95% CI for difference in seroresponse rate is greater than -10%, with a point estimate of >-5%.
d Proportion of participants who met seroresponse definition.
e Seroresponse due to vaccination specific to pseudovirus neutralizing antibody ID50 titer at a subject level is defined as at least 4-fold rise from baseline, where baseline titers <LLOQ are set to LLOQ for the analysis. 95% CI is calculated using the Clopper-Pearson method.
f Difference in seroresponse rate 95% CI is calculated using the Miettinen-Nurminen (score) confidence limits.
Note: SARS-CoV-2 50% inhibitory dose (ID50) neutralization titers were determined using a SARS-CoV-2 Spike-Pseudotyped Virus Neutralization Assay. Quantification of SARS-CoV-2 neutralizing antibodies utilizes lentivirus particles expressing SARS-CoV-2 Spike protein on their surface and contains a firefly luciferase (Luc) reporter gene for quantitative measurements of infection by relative luminescence units (RLU). Neutralization is measured as the serum dilution at which RLU is reduced by 50% (ID50) relative to mean RLU in virus control wells but after subtraction of mean RLU in cell control wells.

A descriptive efficacy analysis evaluating confirmed COVID-19 cases accrued up to the blinded data cutoff date of May 31, 2021, was performed in 3,186 participants who received two doses (at 0 and 1 month) of either SPIKEVAX (n=2,142) or placebo (n=1,044) and had a negative baseline SARS-CoV-2 status (referred to as the Per-Protocol Set for Efficacy). In the Per-Protocol Set for Efficacy, 51.5% were male, 48.5% were female, 11.0% were Hispanic or Latino; 84.0% were White, 2.7% were African American, 6.2% were Asian, 0.5% were American Indian or Alaska Native, <0.1% were Native Hawaiian or Pacific Islander, 0.9% were other races, and 4.8% were Multiracial. There were no notable differences in demographics between participants who received SPIKEVAX and those who received placebo.

The population for the vaccine efficacy analysis included participants 12 years through 17 years of age who were enrolled from December 9, 2020, and followed for the development of COVID-19 through the data cutoff of May 31, 2021. The median length of follow-up for participants in the blinded, placebo-controlled phase of the study was 112 days following Dose 2.

The efficacy information in participants 12 years through 17 years of age is presented in Table 25.

Table 25: Efficacy Analyses: COVID-19 in Participants 12 Years Through 17 Years of Age Starting 14 Days After Dose 2 – Per-Protocol Set for Efficacy
 | SPIKEVAXa; N=2,142 |  | Placebob; N=1,044 |  | % Vaccine Efficacy (95% CI)c
 | COVID-19; Cases; (n) | Incidence Rate; of COVID-19; per 1,000; Person-Years | COVID-19; Cases; (n) | Incidence Rate; of COVID-19; per 1,000; Person-Years | % Vaccine Efficacy (95% CI)c
COVID-19; Case Definition 1d | 0 | 0 | 6 | 21.5 | 100.0; (61.2, NE)
COVID-19; Case Definition 2e | 2 | 3.3 | 9 | 32.4 | 89.9; (51.0, 98.9)
NE=Not estimable
a SPIKEVAX dosing was a two-dose series (100 mcg mRNA per dose) 1 month apart.
b Placebo dosing was a two-dose series (saline solution) 1 month apart.
c Vaccine efficacy defined as 1 ˗ ratio of incidence rate (SPIKEVAX vs. placebo). The 95% CI of the ratio is calculated using the exact method conditional upon the total number of cases, adjusting for person-years.
d COVID-19 Case Definition 1: Participant must have experienced at least two of the following systemic symptoms: fever (≥38°C / ≥100.4°F), chills, myalgia, headache, sore throat, new olfactory and taste disorder(s); or the participant must have experienced at least one of the following respiratory signs/symptoms: cough, shortness of breath or difficulty breathing, or clinical or radiographical evidence of pneumonia; and the participant must have at least one NP swab, nasal swab, or saliva sample (or respiratory sample, if hospitalized) positive for SARS- CoV-2 by RT-PCR.
e COVID-19 Case Definition 2: Presence of at least one symptom from a list of COVID-19 symptoms and a positive NP swab or saliva sample for SARS-CoV-2 by RT-PCR. Listed symptoms were fever (temperature >38°C / ≥100.4°F), or chills, cough, shortness of breath or difficulty breathing, fatigue, muscle aches, or body aches, headache, new loss of taste or smell, sore throat, congestion or runny nose, nausea, or vomiting or diarrhea.

Immunogenicity of a Single Dose (Original Monovalent) in Vaccine-Experienced Adolescents

Effectiveness of a booster dose of SPIKEVAX in participants 12 years through 17 years of age was based on a comparison of immune responses, as assessed by neutralizing antibody concentration against a pseudovirus expressing the original SARS-CoV-2 Spike protein (D614G), following the booster dose in this age group to that following the primary series in adults 18 years through 25 years of age.

In an open-label booster phase of Study 3, participants who were 12 years through 17 years of age at the time of first dose of a primary series received a single booster dose of SPIKEVAX (50 mcg mRNA) at least 5 months (range 2.1-16.9) after completion of the primary series (two doses 1 month apart). The primary immunogenicity analysis population included 264 booster dose participants in Study 3 and a random subset of 295 participants 18 years through 25 years of age from Study 1 who received two doses of SPIKEVAX 1 month apart. Study 1 and Study 3 participants included in the analysis population had no serologic or virologic evidence of SARS-CoV-2 infection prior to the first primary series dose and prior to the booster dose, respectively. Among participants 12 years through 17 years of age assessed for immunogenicity, 50.8% were male, 49.2% were female, 12.5% were Hispanic or Latino; 87.9% were White, 1.5% were African American, 3.4% were Asian, 1.1% were other races, and 5.7% were Multiracial.

The primary immunogenicity analyses of the GMC ratio and difference in seroresponse rates following the booster dose in Study 3 compared to after the primary series in Study 1 met the pre-defined success criteria. Seroresponse for a participant was defined as achieving a ≥4-fold rise of neutralizing antibody concentration from baseline (before the first dose of the primary series in Study 1 and Study 3). These analyses are summarized in Table 26.

Table 26: Comparison of Geometric Mean Concentration and Seroresponse Rate Against a Pseudovirus Expressing the Original SARS-CoV-2 Spike Protein (D614G)* at 28 Days After a Booster Dose of SPIKEVAX in Study 3 (Participants 13 Years Through 19 Years of Age) vs 28 Days After Completion of the Primary Series with SPIKEVAX in Study 1 (Participants 18 Years Through 25 Years of Age) – Per-Protocol Immunogenicity Subsets
Study 3a; Booster Doseb; N=264; GMC; (95% CI)c | Study 1d; Primary Seriese; N=294; GMC; (95% CI)c | GMC Ratio; (Study 3/Study 1); (95% CI)f | Met Success Criteria
7102.0; (6553.2, 7696.8) | 1400.4; (1272.7, 1541.0) | 5.1; (4.5, 5.7) | Yesg
Study 3; Booster Doseb; Seroresponseh; N1=264; %; (95% CI)i | Study 1; Primary Seriese; Seroresponseh; N1=294; %; (95% CI)i | Difference in Seroresponse Rate; (Study 3-Study 1); %; (95% CI)j | Met Success Criterion
100; (98.6, 100.0) | 99.3; (97.6, 99.9) | 0.7; (-0.8, 2.4) | Yesk
N=Number of subjects with non-missing data at the corresponding timepoint.
N1=Number of participants with non-missing data at pre-vaccination baseline and 28 days post-Booster Dose for Study 3 or 28 days post-Dose 2 for Study 1.
* Geometric mean concentration (GMC) was determined using a SARS-CoV-2 Spike-Pseudotyped Virus Neutralization Assay. Quantification of SARS-CoV-2 neutralizing antibodies utilizes a SARS-CoV-2 Reporter Virus Particles which express GFP for quantitative measurement of infection by counting the number of green fluorescent cells (assay readout [count] is Foci Forming Units [FFUs]). The serum antibody concentration (Ab[C]) of the neutralizing antibodies was determined by interpolating the mean of the replicate FFU values off the fitted reference standard curve (AU/mL).
a Per-Protocol Immunogenicity Subset – Pre-Booster SARS-CoV-2 Negative for Study 3 included all subjects who had both pre-booster and post-booster immunogenicity samples, did not have SARS-CoV-2 infection at pre-booster, did not have a major protocol deviation that impacted immune response, and had post-booster immunogenicity assessment at timepoint of primary interest (28 days post-Booster Dose).
b SPIKEVAX dosing was a single booster (50 mcg mRNA).
c 95% CI is calculated based on the t-distribution of the log-transformed values for GMC, then back transformed to the original scale for presentation.
d Per-Protocol Immunogenicity Subset for Study 1 included all subjects who had both baseline (pre-vaccination) and post-vaccination immunogenicity samples, did not have SARS-CoV-2 infection at baseline, did not have a major protocol deviation that impacted immune response, and had post-injection immunogenicity assessment at timepoint of primary interest (28 days post-Dose 2).
e SPIKEVAX dosing was a two-dose series (100 mcg mRNA per dose) 1 month apart.
f The log-transformed antibody levels were analyzed using t-test method with the group variable (Study 3 and Study 1) and 95% CI was calculated based on the t-distribution of the difference in the log-transformed values for GMC. The resulted means and 95% CI were back transformed to the original scale for presentation.
g Success criteria were met if the lower limit of the 2-sided 95% CI for the GMC Ratio is >0.667 and the point estimate of the GMC Ratio is ≥0.8.
h Seroresponse is defined as ≥4-fold rise of pseudovirus neutralizing antibody concentration from baseline (pre-Dose 1 of primary series in Study 3 and Study 1), where baseline concentration < LLOQ is set to LLOQ for the analysis.
i 95% CI is calculated using the Clopper-Pearson method.
j 95% CI is calculated using the Miettinen-Nurminen (score) confidence limits.
k Success criterion is met if the lower limit of the 2-sided 95% CI for the percentage difference is ≥-10%.
Note: Antibody values < the lower limit of quantitation (LLOQ) are replaced by 0.5 × LLOQ. Values > the upper limit of quantitation (ULOQ) are replaced by the ULOQ if actual values are not available.

A descriptive analysis evaluated seroresponse rates using pre-booster neutralizing antibody concentration. The booster dose seroresponse rate, with seroresponse defined as at least a 4-fold rise relative to the pre-booster concentration, was 96.6%. The difference in seroresponse rates in this post-hoc analysis was -2.7% (95% CI: -5.8%, -0.5%).

Immunogenicity of Single Dose (Bivalent Original and Omicron BA.4/BA.5) in Vaccine-Naïve Adolescents with Evidence of Prior SARS-CoV-2 Infection

In an open-label phase of Study 3 conducted in the United States and the Dominican Republic, participants 12 years through 17 years of age who were COVID-19 vaccine-naïve received a single dose (50 mcg mRNA) of Moderna COVID-19 Vaccine, Bivalent. Of the 246 participants in the immunogenicity subset, 99.6% had evidence of prior SARS-CoV-2 infection at baseline (immunologic or virologic evidence of prior SARS-CoV-2 infection [defined as positive RT-PCR test and/or positive Elecsys immunoassay result at Day 1]). The primary immunogenicity analysis population included 245 participants who were baseline SARS-COV-2 positive in Study 3 and a subset of 296 participants 18 years through 25 years of age from Study 1 who had no evidence of prior SARS-CoV-2 infection at baseline and received two doses (100 mcg mRNA per dose) of SPIKEVAX 1 month apart. Among participants 12 years through 17 years of age assessed for immunogenicity, 53.5% were male, 46.5% were female, 94.3% were Hispanic or Latino, 14.3% were White, 33.9% were African American or Black, 51.0% were other races, and 0.8% were Multiracial.

A comparison of neutralizing antibody concentrations against a pseudovirus expressing Omicron BA.4/BA.5 and the original SARS-CoV-2 Spike protein (D614G) was conducted. The primary immunogenicity analyses of the GMC ratio following the single dose in Study 3 compared to after the primary series in Study 1 met the pre-defined success criteria for superiority against Omicron BA.4/BA.5 and noninferiority against the Original strain. Secondary analyses included the difference in seroresponse rates, where seroresponse for a participant was defined as achieving a ≥4-fold rise of neutralizing antibody concentration from baseline (before the first dose of the primary series in Study 1 and the single dose in Study 3). These analyses are summarized in Table 27.

Table 27: Comparison of Geometric Mean Concentration and Seroresponse Rate 28 Days After a Single Dose of Moderna COVID-19 Vaccine, Bivalent in Study 3 (Participants 12 Years Through 17 Years of Age) vs 28 Days After Completion of the Primary Series of SPIKEVAX in Study 1 (Participants 18 Years Through 25 Years of Age) – Per-Protocol Immunogenicity Subsets
Assaya | Moderna COVID-19; Vaccine, Bivalentb; Single Dosec; GMC; (95% CI)d | SPIKEVAXe; Primary Seriesf; GMC; (95% CI)d | GMC Ratio; (Moderna COVID-19 Vaccine, Bivalent/ SPIKEVAX); (95% CI)d,g
Omicron BA.4/BA.5 | 2771.0; (2570.0, 2987.6); N=245 | 56.6; (52.8, 60.6); N=294 | 49.0; (44.2, 54.2)
Original SARS-CoV-2 (D614G) | 7187.1; (6480.5, 7970.8); N=243 | 1692.3; (1540.6, 1858.9); N=295 | 4.2; (3.7, 4.9)
 | Moderna COVID-19; Vaccine, Bivalent; Single Dosec; Seroresponseh; %; (95% CI)i | SPIKEVAX; Primary Seriese; Seroresponseh; %; (95% CI)i | Difference in; Seroresponse Rate; (Moderna COVID-19 Vaccine, Bivalent- SPIKEVAX); %; (95% CI)j
Omicron BA.4/BA.5 | 94.7; (91.1, 97.1); N=245 | 0; (0, 1.2); N=294 | 94.7; (91.1, 96.9)
Original SARS-CoV-2 (D614G) | 94.6; (91.0, 97.1); N=241 | 99.3; (97.6, 99.9); N=295 | -4.7; (-8.4, -2.1)
N=Number of participants with non-missing data at the corresponding timepoint(s).
a Geometric mean concentration (GMC) was determined using a SARS-CoV-2 Spike-Pseudotyped Virus Neutralization Assay. Quantification of SARS-CoV-2 neutralizing antibodies utilizes a SARS-CoV-2 Reporter Virus Particles which express GFP for quantitative measurement of infection by counting the number of green fluorescent cells (assay readout [count] is Foci Forming Units [FFUs]). The serum antibody concentration (Ab[C]) of the neutralizing antibodies was determined by interpolating the mean of the replicate FFU values off the fitted reference standard curve (AU/mL).
b Per-Protocol Immunogenicity Subset – Baseline SARS-CoV-2 Positive for Study 3 included all subjects who had serologic or virologic evidence of prior SARS-CoV-2 infection pre-dose 1, did not have a major protocol deviation that impacted immune response, and had both pre-Dose 1 and post-Dose 1 immunogenicity assessment at timepoint of primary interest (28 days post-Dose 1).
c Moderna COVID-19 Vaccine, Bivalent dosing was a single dose (50 mcg mRNA).
d The log-transformed antibody levels are analyzed using an analysis of covariance (ANCOVA) model with the group variable (Study 3 and Study 1) as fixed effect. The resulted LS means, difference of LS means, and 95% CI are back transformed to the original scale for presentation.
e Per-Protocol Immunogenicity Subset for Study 1 included all subjects who had both baseline (pre-vaccination) and post-vaccination immunogenicity samples, did not have SARS-CoV-2 infection at baseline, did not have a major protocol deviation that impacted immune response, and had post-injection immunogenicity assessment at timepoint of primary interest (28 days post-Dose 2).
f SPIKEVAX dosing was a two-dose series (100 mcg mRNA per dose) 1 month apart.
g The superiority of GMC against Omicron BA.4/BA.5 is demonstrated if the lower limit of the 2-sided 95% CI for the GMC Ratio is >1. The noninferiority of GMC against Original SARS-CoV-2 (D614G) is demonstrated if the lower limit of the 2-sided 95% CI for the GMC Ratio is >0.667.
h Seroresponse rate at Day 29 (in Study 3) and at Day 57 (in Study 1) from baseline (pre-Dose 1) is defined as the percentage of participants with at least a 4-fold rise if baseline is equal to or above LLOQ, or a change from a baseline below the LLOQ to equal or above 4 × LLOQ.
i 95% CI is calculated using the Clopper-Pearson method.
j 95% CI is calculated using the Miettinen-Nurminen (score) confidence limits.
Note: Antibody values < the lower limit of quantitation (LLOQ) are replaced by 0.5 × LLOQ. Values > the upper limit of quantitation (ULOQ) are replaced by the ULOQ if actual values are not available.

14.3 Infants and Children 6 Months Through 11 Years of Age

Effectiveness of 2-Dose Series (Original Monovalent) in Vaccine-Naïve Children 6 Years Through 11 Years of Age (Study 4)

Study 4 included a randomized, placebo-controlled, observer-blind phase to evaluate the safety, reactogenicity, and effectiveness of SPIKEVAX in individuals 6 years through 11 years of age in the United States and Canada. Participants with a known history of SARS-CoV-2 infection within 2 weeks of study vaccination were excluded from the study. A total of 4,015 participants were randomized 3:1 to receive 2 doses of SPIKEVAX (50 mcg mRNA per dose) or saline placebo 1 month apart.

Effectiveness in individuals 6 years through 11 years of age is based on comparison of SARS-CoV-2 50% neutralizing titers and seroresponse rates 28 days after Dose 2 in a subset of individuals 6 years through 11 years of age in Study 4 and participants 18 years through 25 years of age in Study 1 who had no immunologic or virologic evidence of prior SARS-CoV-2 at baseline (Table 28). Demographics in the subset of individuals 6 years through 11 years of age in this analysis were consistent with the overall demographics in this phase of Study 4.

Table 28: Comparison of Geometric Mean Titer and Seroresponse Rate Against a Pseudovirus Expressing Original SARS-CoV-2 Spike Protein (D614G)* for Individuals 6 Years Through 11 Years of Age (Study 4) to Participants 18 Years Through 25 Years of Age (Study 1) at 28 Days After Dose 2 – Per-Protocol Immunogenicity Set
 |  | SPIKEVAX
 |  | 6 Years Through 11 Yearsa | 18 Years Through 25 Yearsb | 6 Years Through 11 Years/; 18 Years Through 25 Years
Assay | Time Point | GMT; (95% CI)c; N=309 | GMT; (95% CI)c; N=294 | GMT ratio; (95% CI)c | Met; Noninferiority Objective; (Y/N)d
SARS-CoV-2 neutralization assay – ID50 (titer) | 28 days after Dose 2 | 1618.3; (1464.3, 1788.6) | 1321.9; (1193.1, 1464.6) | 1.2; (1.1, 1.4) | Yes
SARS-CoV-2 neutralization assay – ID50 (titer) | 28 days after Dose 2 | Seroresponse; %; (95% CI)e; N1=307 | Seroresponse; %; (95% CI)e; N1=294 | Difference in Seroresponse Rate %; (95% CI)f | Met; Noninferiority Objective; (Y/N)d
SARS-CoV-2 neutralization assay – ID50 (titer) | 28 days after Dose 2 | 99.0; (97.2, 99.8) | 99.3; (97.6, >99.9) | -0.3; (-2.2, 1.6) | Yes
GMT=Geometric mean titer
N=Number of subjects with non-missing data at the corresponding timepoint (Day 57).
N1=Number of subjects with non-missing data at baseline and the corresponding post-baseline timepoint (Day 57).
* SARS-CoV-2 50% inhibitory dose (ID50) neutralization titers were determined using a SARS-CoV-2 Spike-Pseudotyped Virus Neutralization Assay. Quantification of SARS-CoV-2 neutralizing antibodies utilizes lentivirus particles expressing SARS-CoV-2 Spike protein on their surface and contains a firefly luciferase (Luc) reporter gene for quantitative measurements of infection by relative luminescence units (RLU). Neutralization is measured as the serum dilution at which RLU is reduced by 50% (ID50) relative to mean RLU in virus control wells but after subtraction of mean RLU in cell control wells.
a SPIKEVAX dosing was a two-dose series (50 mcg mRNA per dose) 1 month apart, Study 4.
b SPIKEVAX dosing was a two-dose series (100 mcg mRNA per dose) 1 month apart, Study 1.
c The log-transformed antibody levels are analyzed using an analysis of covariance (ANCOVA) model with the group variable (individuals in Study 4 and young adults in Study 1) as fixed effect. The resulted LS means, difference of LS means, and 95% CI are back transformed to the original scale for presentation.
d Noninferiority is declared if the lower bound of the 2-sided 95% CI for the GMT ratio is greater than 0.667, with a point estimate of ≥0.8 and the lower bound of the 2-sided 95% CI for difference in seroresponse rate is greater than -10%, with a point estimate of ≥-5%.
e Seroresponse due to vaccination specific to pseudovirus neutralizing antibody ID50 titer at a subject level is defined in protocol as a change from below LLOQ to equal or above 4 x LLOQ, or at least a 4-fold rise if baseline is equal to or above LLOQ. Seroresponse 95% CI is calculated using the Clopper-Pearson method.
f Difference in seroresponse rate 95% CI is calculated using the Miettinen-Nurminen (score) confidence limits.
Note: Antibody values reported as below the lower limit of quantification (LLOQ) are replaced by 0.5 x LLOQ. Values greater than the upper limit of quantification (ULOQ) are replaced by the ULOQ if actual values are not available.

A descriptive efficacy analysis evaluating confirmed COVID-19 cases accrued between September 1, 2021 through the date of individual participant unblinding, was performed in 3,578 participants 6 years through 11 years of age who received two doses (at 0 and 1 month) of either SPIKEVAX or placebo, had a negative baseline SARS-CoV-2 status, and received the correct treatment (referred to as the modified Intent-to-Treat-1 [mITT-1] Set) (vaccine=2,694, placebo=884). Between participants who received SPIKEVAX and those who received placebo, there were no notable differences in demographics.

Vaccine efficacy among individuals 6 years through 11 years of age in Study 4 was evaluated during the period when Delta was the predominant strain in circulation.

The efficacy information in individuals 6 years through 11 years of age is presented in Table 29.

Table 29: Efficacy Analyses: COVID-19 in Participants 6 Years Through 11 Years of Age Starting 14 Days After Dose 1 – Modified Intent-to-Treat-1 Set*
 | SPIKEVAXa; N=2,694 |  | Placebob; N=884 |  | % Vaccine Efficacy (95% CI)c
 | Cases; (n) | Incidence Rate; of COVID-19; per 1,000; Person-Years | Cases; (n) | Incidence Rate; of COVID-19; per 1,000; Person-Years | % Vaccine Efficacy (95% CI)c
COVID-19 Cases - Definition 1d | 9 | 17.7 | 16 | 103.1 | 82.8; (58.7, 93.3)
COVID-19 Cases - Definition 2e | 12 | 23.7 | 19 | 122.6 | 80.7; (58.1, 91.5)
* Modified Intent-to-Treat-1 Set included all participants in the full analysis set who were SARS-CoV-2 negative at baseline and received at least one dose of vaccine or placebo without wrong treatment.
a SPIKEVAX dosing was a two-dose series (50 mcg mRNA per dose) 1 month apart.
b Placebo dosing was a two-dose series (saline solution) 1 month apart.
c Vaccine efficacy defined as 1 ˗ ratio of incidence rate (SPIKEVAX vs. placebo). The 95% CI of the ratio is calculated using the exact method conditional upon the total number of cases, adjusting for person-years.
d Participant must have experienced at least two of the following systemic symptoms: fever (≥38°C / ≥100.4°F), chills, myalgia, headache, sore throat, new olfactory and taste disorder(s); or the participant must have experienced at least one of the following respiratory signs/symptoms: cough, shortness of breath or difficulty breathing, or clinical or radiographical evidence of pneumonia; and the participant must have at least one NP swab, nasal swab, or saliva sample (or respiratory sample, if hospitalized) positive for SARS-CoV-2 by RT-PCR.
e Presence of at least one symptom from a list of COVID-19 symptoms and a positive NP swab or saliva sample for SARS-CoV-2 by RT-PCR. Listed symptoms were fever (temperature >38°C / ≥100.4°F), or chills, cough, shortness of breath or difficulty breathing, fatigue, muscle aches, or body aches, headache, new loss of taste or smell, sore throat, congestion or runny nose, nausea, abdominal pain, poor appetite/poor feeding, or vomiting or diarrhea.

Effectiveness of 2-Dose Series (Original Monovalent) in Vaccine-Naïve Infants and Children 6 Months Through 5 Years of Age (Study 4)

Study 4 included a randomized, placebo-controlled, observer-blind phase to evaluate the safety, reactogenicity, and effectiveness of SPIKEVAX in individuals 6 months through 5 years of age in the United States and Canada. Participants with a known history of SARS-CoV-2 infection within 2 weeks of study vaccination were excluded from the study. A total of 6,712 participants were randomized 3:1 to receive 2 doses of SPIKEVAX (25 mcg mRNA per dose) or saline placebo 1 month apart.

Effectiveness in individuals 6 months through 5 years of age is based on a comparison of SARS-CoV-2 neutralizing antibody concentrations and seroresponse rates 28 days after Dose 2 in a subset of individuals 6 months through 5 years of age in Study 4 and participants 18 years through 25 years of age in Study 1 who had no immunologic or virologic evidence of prior SARS-CoV-2 at baseline (Table 30 and Table 31). Demographics in the subset of individuals 6 months through 5 years of age in this analysis were consistent with the overall demographics in this phase of Study 4.

Table 30: Comparison of Geometric Mean Concentration and Seroresponse Rate Against a Pseudovirus Expressing the Original SARS-CoV-2 Spike Protein (D614G)* for Individuals 6 Months Through 23 Months of Age (Study 4) to Participants 18 Years Through 25 Years of Age (Study 1) at 28 Days After Dose 2 – Per-Protocol Immunogenicity Set
 |  | SPIKEVAX
 |  | 6 Months Through 23 Monthsa | 18 Years Through 25 Yearsb | 6 Months Through 23 Months/; 18 Years Through 25 Years
Assay | Time Point | GMC; (95% CI); N=268 | GMC; (95% CI); N=294 | GMC Ratio; (95% CI)c | Met; Noninferiority Objective; (Y/N)d
SARS-CoV-2 neutralization assay | 28 days after Dose 2 | 1759.8; (1599.2, 1936.5) | 1400.4; (1278.1, 1534.4) | 1.3; (1.1, 1.4) | Yes
SARS-CoV-2 neutralization assay | 28 days after Dose 2 | Seroresponse; %; (95% CI)e; N1=264 | Seroresponse; %; (95% CI)e; N1=294 | Difference in Seroresponse Rate %; (95% CI)f | Met; Noninferiority Objective; (Y/N)d
SARS-CoV-2 neutralization assay | 28 days after Dose 2 | 100; (98.6, 100) | 99.3; (97.6, >99.9) | 0.7; (-0.8, 2.4) | Yes
N=Number of subjects with non-missing data at the corresponding timepoint (Day 57).
N1=Number of subjects with non-missing data at baseline and the corresponding post-baseline timepoint (Day 57).
* Geometric mean concentration (GMC) was determined using a SARS-CoV-2 Spike-Pseudotyped Virus Neutralization Assay. Quantification of SARS-CoV-2 neutralizing antibodies utilizes a SARS-CoV-2 Reporter Virus Particles which express GFP for quantitative measurement of infection by counting the number of green fluorescent cells (assay readout [count] is Foci Forming Units [FFUs]). The serum antibody concentration (Ab[C]) of the neutralizing antibodies was determined by interpolating the mean of the replicate FFU values off the fitted reference standard curve (AU/mL).
a SPIKEVAX dosing was a two-dose series (25 mcg mRNA per dose) 1 month apart, Study 4.
b SPIKEVAX dosing was a two-dose series (100 mcg mRNA per dose) 1 month apart, Study 1.
c The log-transformed antibody levels are analyzed using an analysis of covariance (ANCOVA) model with the group variable (individuals in Study 4 and young adults in Study 1) as fixed effect. The resulted LS means, difference of LS means, and 95% CI are back transformed to the original scale for presentation.
d Noninferiority is declared if the lower bound of the 2-sided 95% CI for the GMC ratio is greater than 0.67, with a point estimate of ≥0.8 and the lower bound of the 2-sided 95% CI for difference in seroresponse rate is greater than -10%, with a point estimate of ≥-5%.
e Seroresponse due to vaccination specific to SARS-CoV-2 RVP neutralizing antibody concentration at a subject level is defined in protocol as a change from below LLOQ to equal or above 4 x LLOQ, or at least a 4-fold rise if baseline is equal to or above LLOQ. Seroresponse 95% CI is calculated using the Clopper-Pearson method.
f Difference in seroresponse rate 95% CI is calculated using the Miettinen-Nurminen (score) confidence limits.
Note: Antibody values reported as below the lower limit of quantification (LLOQ) are replaced by 0.5 x LLOQ. Values greater than the upper limit of quantification (ULOQ) are replaced by the ULOQ if actual values are not available.

Table 31: Comparison of Geometric Mean Concentration and Seroresponse Rate Against a Pseudovirus Expressing the Original SARS-CoV-2 Spike Protein (D614G)* for Individuals 2 Years Through 5 Years of Age (Study 4) to Participants 18 Years Through 25 Years of Age (Study 1) – Per-Protocol Immunogenicity Set
 |  | SPIKEVAX
 |  | 2 Years Through 5 Yearsa | 18 Years Through 25 Yearsb | 2 Years Through 5 Years/; 18 Years Through 25 Years
Assay | Time Point | GMC; (95% CI); N=289 | GMC; (95% CI); N=294 | GMC Ratio; (95% CI)c | Met; Noninferiority Objective; (Y/N)d
SARS-CoV-2 neutralization assay | 28 days after Dose 2 | 1394.1; (1267.0, 1533.9) | 1400.4; (1273.8, 1539.6) | 1.0; (0.9, 1.1) | Yes
SARS-CoV-2 neutralization assay | 28 days after Dose 2 | Seroresponse; %; (95% CI)e; N1=284 | Seroresponse; %; (95% CI)e; N1=294 | Difference in Seroresponse Rate %; (95% CI)f | Met; Noninferiority Objective; (Y/N)d
SARS-CoV-2 neutralization assay | 28 days after Dose 2 | 98.9; (96.9, 99.8) | 99.3; (97.6, >99.9) | -0.4; (-2.5, 1.5) | Yes
N=Number of subjects with non-missing data at the corresponding timepoint (Day 57).
N1=Number of subjects with non-missing data at baseline and the corresponding post-baseline timepoint (Day 57).
* Geometric mean concentration (GMC) was determined using a SARS-CoV-2 Spike-Pseudotyped Virus Neutralization Assay. Quantification of SARS-CoV-2 neutralizing antibodies utilizes a SARS-CoV-2 Reporter Virus Particles which express GFP for quantitative measurement of infection by counting the number of green fluorescent cells (assay readout [count] is Foci Forming Units [FFUs]). The serum antibody concentration (Ab[C]) of the neutralizing antibodies was determined by interpolating the mean of the replicate FFU values off the fitted reference standard curve (AU/mL).
a SPIKEVAX dosing was a two-dose series (25 mcg mRNA per dose) 1 month apart, Study 4.
b SPIKEVAX dosing was a two-dose series (100 mcg mRNA per dose) 1 month apart, Study 1.
c The log-transformed antibody levels are analyzed using an analysis of covariance (ANCOVA) model with the group variable (individuals in Study 4 and young adults in Study 1) as fixed effect. The resulted LS means, difference of LS means, and 95% CI are back transformed to the original scale for presentation.
d Noninferiority is declared if the lower bound of the 2-sided 95% CI for the GMC ratio is greater than 0.67, with a point estimate of ≥0.8 and the lower bound of the 2-sided 95% CI for difference in seroresponse rate is greater than -10%, with a point estimate of ≥-5%.
e Seroresponse due to vaccination specific to SARS-CoV-2 RVP neutralizing antibody concentration at a subject level is defined in protocol as a change from below LLOQ to equal or above 4 x LLOQ, or at least a 4-fold rise if baseline is equal to or above LLOQ. Seroresponse 95% CI is calculated using the Clopper-Pearson method.
f Difference in seroresponse rate 95% CI is calculated using the Miettinen-Nurminen (score) confidence limits.
Note: Antibody values reported as below the lower limit of quantification (LLOQ) are replaced by 0.5 x LLOQ. Values greater than the upper limit of quantification (ULOQ) are replaced by the ULOQ if actual values are not available.

A descriptive efficacy analysis evaluating confirmed COVID-19 cases accrued between November 1, 2021, through the blinded cutoff date of June 30, 2022, was performed in 5,693 participants 6 months through 5 years of age who received two doses (at 0 and 1 month) of either SPIKEVAX or placebo and had a negative baseline SARS-CoV-2 status (referred to as the Per-Protocol Set for Efficacy) (for participants 6 months through 23 months, vaccine=1,686, placebo=563; for participants 2 years through 5 years, vaccine=2,592, placebo=854). Between participants who received SPIKEVAX and those who received placebo, there were no notable differences in demographics.

The median length of follow-up for efficacy post-Dose 2 was 182 days for participants 6 months through 23 months of age and 186 days for participants 2 years through 5 years of age. Vaccine efficacy among individuals 6 months through 5 years of age in Study 4 was evaluated during the period when the B.1.1.529 (Omicron) variant was the predominant variant in circulation. The efficacy information in individuals 6 months through 23 months of age and 2 years through 5 years of age are presented in Table 32 and Table 33, respectively.

Table 32: Efficacy Analyses: COVID-19 in Participants 6 Months Through 23 Months of Age Starting 14 Days After Dose 2 – Per Protocol Set for Efficacy
 | SPIKEVAXa; N=1,686 |  | Placebob; N=563 |  | % Vaccine Efficacy (95% CI)c
 | Cases; (n) | Incidence Rate; of COVID-19; per 1,000; Person-Years | Cases; (n) | Incidence Rate; of COVID-19; per 1,000; Person-Years | % Vaccine Efficacy (95% CI)c
COVID-19 Cases - Definition 1d | 88 | 100.6 | 37 | 128.8 | 21.9; (-18.0, 47.4)
COVID-19 Cases - Definition 2e | 130 | 150.2 | 73 | 264.2 | 43.2; (23.2, 57.6)
N=Included 5 individuals aged 2 years to 4 years randomized in the 6 months through 23 months of age group stratum (all in the SPIKEVAX group), and none of them had a COVID-19 case starting 14 days after Dose 2.
a SPIKEVAX dosing was a two-dose series (25 mcg mRNA per dose) 1 month apart.
b Placebo dosing was a two-dose series (saline solution) 1 month apart.
c Vaccine efficacy defined as 1 ˗ ratio of incidence rate (SPIKEVAX vs. placebo). The 95% CI of the ratio is calculated using the exact method conditional upon the total number of cases, adjusting for person-years.
d Participant must have experienced at least two of the following systemic symptoms: fever (≥38°C / ≥100.4°F), chills, myalgia, headache, sore throat, new olfactory and taste disorder(s); or the participant must have experienced at least one of the following respiratory signs/symptoms: cough, shortness of breath or difficulty breathing, or clinical or radiographical evidence of pneumonia; and the participant must have at least one NP swab, nasal swab, or saliva sample (or respiratory sample, if hospitalized) positive for SARS-CoV-2 by RT-PCR.
e Presence of at least one symptom from a list of COVID-19 symptoms and a positive NP swab or saliva sample for SARS-CoV-2 by RT-PCR. Listed symptoms were fever (temperature >38°C / ≥100.4°F), or chills, cough, shortness of breath or difficulty breathing, fatigue, muscle aches, or body aches, headache, new loss of taste or smell, sore throat, congestion or runny nose, nausea, abdominal pain, poor appetite/poor feeding, or vomiting or diarrhea.

Table 33: Efficacy Analyses: COVID-19 in Participants 2 Years Through 5 Years of Age Starting 14 Days After Dose 2 – Per-Protocol Set for Efficacy
 | SPIKEVAXa; N=2,592 |  | Placebob; N=854 |  | % Vaccine Efficacy (95% CI)c
 | Cases; (n) | Incidence Rate; of COVID-19; per 1,000; Person-Years | Cases; (n) | Incidence Rate; of COVID-19; per 1,000; Person-Years | % Vaccine Efficacy (95% CI)c
COVID-19 Cases - Definition 1d | 142 | 102.9 | 83 | 184.8 | 44.3; (26.1, 57.8)
COVID-19 Cases - Definition 2e | 207 | 152.2 | 125 | 285.0 | 46.6; (32.8, 57.4)
N=Included 19 individuals younger than 2 years of age randomized in the 2 years through 5 years of age group stratum (13 in the SPIKEVAX group and 6 in the placebo group). For Definition 1, one individual in the SPIKEVAX group and one in the placebo group had a COVID-19 case starting 14 days after Dose 2. For Definition 2, two individuals in the SPIKEVAX group and one in the placebo group had a COVID-19 case starting 14 days after Dose 2.
a SPIKEVAX dosing was a two-dose series (25 mcg mRNA per dose) 1 month apart.
b Placebo dosing was a two-dose series (saline solution) 1 month apart.
c Vaccine efficacy defined as 1 ˗ ratio of incidence rate (SPIKEVAX vs. placebo). The 95% CI of the ratio is calculated using the exact method conditional upon the total number of cases, adjusting for person-years.
d Participant must have experienced at least two of the following systemic symptoms: fever (≥38°C / ≥100.4°F), chills, myalgia, headache, sore throat, new olfactory and taste disorder(s); or the participant must have experienced at least one of the following respiratory signs/symptoms: cough, shortness of breath or difficulty breathing, or clinical or radiographical evidence of pneumonia; and the participant must have at least one NP swab, nasal swab, or saliva sample (or respiratory sample, if hospitalized) positive for SARS-CoV-2 by RT-PCR.
e Presence of at least one symptom from a list of COVID-19 symptoms and a positive NP swab or saliva sample for SARS-CoV-2 by RT-PCR. Listed symptoms were fever (temperature >38°C / ≥100.4°F), or chills, cough, shortness of breath or difficulty breathing, fatigue, muscle aches, or body aches, headache, new loss of taste or smell, sore throat, congestion or runny nose, nausea, abdominal pain, poor appetite/poor feeding, or vomiting or diarrhea.

Immunogenicity of Single Dose (Monovalent Omicron XBB.1.5) in Vaccine-Naïve Children 2 Years Through 4 Years of Age and 2-Dose Series (Monovalent Omicron XBB.1.5) in Vaccine-Naïve Infants and Children 6 Months Through 23 Months of Age (Study 6)

Study 6 is an ongoing open-label clinical trial that included a phase conducted in the United States, Panama, and the Dominican Republic in which participants 2 years through 4 years of age who were COVID-19 vaccine-naïve received a single dose (25 mcg mRNA) of SPIKEVAX (2023-2024 Formula) and individuals 6 months through 23 months of age received two doses (25 mcg mRNA) of SPIKEVAX (2023-2024 Formula). Of the 148 participants 2 years through 4 years of age in the immunogenicity subset, 96.6% had evidence of prior SARS-CoV-2 infection at baseline (immunologic or virologic evidence of prior SARS-CoV-2 infection [defined as positive RT-PCR test and/or positive Elecsys immunoassay result at Day 1]). The primary immunogenicity analysis population included 143 participants 2 years through 4 years of age who were baseline SARS-CoV-2 positive and received a single dose of SPIKEVAX (2023-2024 Formula) and a subset of 76 participants 6 months through 23 months of age who had no evidence of prior SARS-CoV-2 infection at baseline and received two doses (25 mcg mRNA per dose) of SPIKEVAX (2023-2024 Formula) 1 month apart. Demographics in the subsets of individuals 6 months through 23 months of age and 2 years through 4 years of age in this analysis were consistent with the overall demographics in this phase of Study 4.

A comparison of neutralizing antibody concentrations against a pseudovirus expressing Omicron XBB.1.5 was conducted. The primary immunogenicity analyses of the GMC ratio following the single dose compared to after the primary series met the pre-defined success criteria for noninferiority against Omicron XBB.1.5 (Table 34).

Table 34: Comparison of Geometric Mean Concentration 28 Days After a Single Dose of SPIKEVAX (2023-2024 Formula) (Participants 2 Years Through 4 Years of Age) vs 28 Days After Completion of the Primary Series of SPIKEVAX (2023-2024 Formula) (Participants 6 Months Through 23 Months of Age) – Per-Protocol Immunogenicity Subsets
Assaya | 2 Years Through 4 Yearsb; Single Dosec; GMC; (95% CI)d | 6 Months Through 23 Monthse; Primary Seriesf; GMC; (95% CI)d | GMC Ratio; (2 Years Through 4 Years/ 6 Months Through 23 Months); (95% CI)d,g
Omicron XBB.1.5 | 2074.1; (1637.8, 2626.7); N=143 | 1736.3; (1255.8, 2400.6); N=76 | 1.2; (0.8, 1.8)
N=Number of participants with non-missing data at the corresponding timepoint(s).
a Geometric mean concentration (GMC) was determined using a SARS-CoV-2 Spike-Pseudotyped Virus Neutralization Assay. Quantification of SARS-CoV-2 neutralizing antibodies utilizes a SARS-CoV-2 Reporter Virus Particles which express GFP for quantitative measurement of infection by counting the number of green fluorescent cells (assay readout [count] is Foci Forming Units [FFUs]). The serum antibody concentration (Ab[C]) of the neutralizing antibodies was determined by interpolating the mean of the replicate FFU values off the fitted reference standard curve (AU/mL).
b Per-Protocol Immunogenicity Subset – Baseline SARS-CoV-2 Positive for Study 6 included all subjects 2 years through 4 years of age who had serologic or virologic evidence of prior SARS-CoV-2 infection pre-dose, did not have a major protocol deviation that impacted immune response, and had immunogenicity assessment at timepoint of primary interest (28 days post-dose).
c SPIKEVAX (2023-2024 Formula) dosing was a single dose (25 mcg mRNA).
d The log-transformed antibody levels are analyzed using an analysis of covariance (ANCOVA) model with the group variable (2 years through 4 years single dose and 6 months through 23 months primary series) as fixed effect. The resulted LS means, difference of LS means, and 95% CI are back transformed to the original scale for presentation.
e Per-Protocol Immunogenicity Subset – Baseline SARS-CoV-2 Negative included all subjects 6 months through 23 months of age who did not have serologic or virologic evidence of prior SARS-CoV-2 infection at baseline, did not have a major protocol deviation that impacted immune response, and had immunogenicity assessment at timepoint of primary interest (28 days post-Dose 2).
f SPIKEVAX (2023-2024 Formula) dosing was a two-dose series (25 mcg mRNA per dose) 1 month apart.
g The noninferiority of GMC against Omicron XBB.1.5 is demonstrated if the lower limit of the 2-sided 95% CI for the GMC Ratio is >0.667.
Note: Antibody values < the lower limit of quantitation (LLOQ) are replaced by 0.5 × LLOQ. Values > the upper limit of quantitation (ULOQ) are replaced by the ULOQ if actual values are not available.

Secondary analyses included seroresponse rates, where seroresponse for a participant was defined as achieving a ≥4-fold rise of neutralizing antibody concentration from baseline (before the first dose of the primary series or the single dose) if baseline values were ≥ LLOQ, otherwise, 4 times LLOQ. In the 2 years through 4 years single dose group who had evidence of prior SARS-CoV-2 infection at baseline, 73.4% (95% CI: 65.2%, 80.5%) of participants achieved seroresponse against Omicron XBB.1.5. In the 6 months through 23 months primary series group who had no evidence of prior SARS-CoV-2 infection at baseline, 96.1% (95% CI: 88.9%, 99.2%) of participants achieved seroresponse. The seroresponse rate difference between the two age groups was -22.7% (95% CI: -31.3%, -13.5%). The noninferiority criterion for seroresponse rate difference (lower bound of the 95% CI >-10%) was not met.

Immunogenicity of Single Dose (Original Monovalent) in Vaccine-Experienced Children 6 Years Through 11 Years of Age (Study 4)

Effectiveness of a booster dose of SPIKEVAX in participants 6 years through 11 years of age was based on a comparison of immune responses, as assessed by neutralizing antibody concentration against a pseudovirus expressing the original SARS-CoV-2 Spike protein (D614G), following the booster dose in this age group to that following the primary series in young adults 18 years through 25 years.

In an open-label phase of Study 4, participants 6 years through 11 years of age received a single booster dose of SPIKEVAX (25 mcg mRNA) at least 6 months after completion of the primary series (two doses 1 month apart). The primary immunogenicity analysis population included 137 booster dose participants in Study 4 and a random subset of 296 participants 18 years through 25 years of age from Study 1 who received two doses of SPIKEVAX 1 month apart. Study 1 and Study 4 participants included in the analysis population had no serologic or virologic evidence of SARS-CoV-2 infection prior to the first primary series dose and prior to the booster dose, respectively. Demographics in the subset of individuals 6 years through 11 years of age in this analysis were consistent with the overall demographics in this phase of Study 4.

The primary immunogenicity analyses of the GMC ratio and difference in seroresponse rates following the booster dose in Study 4 compared to following the primary series in Study 1 met the pre-defined immunobridging success criteria. Seroresponse for a participant was defined as achieving a ≥4-fold rise of neutralizing antibody concentration from baseline (before the first dose of the primary series in Study 4 and Study 1). These analyses are summarized in Table 35.

Table 35: Comparison of Geometric Mean Concentration and Seroresponse Rate Against a Pseudovirus Expressing the Original SARS-CoV-2 Spike Protein (D614G)* at 28 Days After a Booster Dose in Participants 6 Years Through 11 Years of Age (Study 4) vs 28 Days After Completion of the Primary Series in Participants 18 Years Through 25 Years of Age (Study 1) – Per-Protocol Immunogenicity Subsets
Study 4a; Booster Doseb; GMC; (95% CI); N=137 | Study 1c; Primary Seriesd; GMC; (95% CI); N=294 | GMC Ratio; (Study 4/Study 1) | Met Success Criterion
5575.9; (4899.2, 6346.0) | 1400.4; (1282.0, 1529.7) | 4.0; (3.4, 4.7) | Yese
Study 4; Booster Doseb; Seroresponsef; %; (95% CI)g; N1=129 | Study 1; Primary Seriesd; Seroresponsef; %; (95% CI)g; N1=294 | Difference in Seroresponse Rate; (Study 4-Study 1); %; (95% CI)h | Met Success Criterion
100; (97.2, 100) | 99.3; (97.6, >99.9) | 0.7; (-2.2, 2.4) | Yesi
N=Number of subjects with non-missing data at the corresponding timepoint.
N1=Number of participants with non-missing data at pre-vaccination baseline and the corresponding timepoint (28 days post-Booster Dose for Study 4 or 28 days post-Dose 2 for Study 1).
* Geometric mean concentration (GMC) was determined using a SARS-CoV-2 Spike-Pseudotyped Virus Neutralization Assay. Quantification of SARS-CoV-2 neutralizing antibodies utilizes a SARS-CoV-2 Reporter Virus Particles which express GFP for quantitative measurement of infection by counting the number of green fluorescent cells (assay readout [count] is Foci Forming Units [FFUs]). The serum antibody concentration (Ab[C]) of the neutralizing antibodies was determined by interpolating the mean of the replicate FFU values off the fitted reference standard curve (AU/mL).
a Per-Protocol Immunogenicity Subset – Pre-Booster SARS-CoV-2 Negative for Study 4 included all subjects who had both pre-booster and post-booster immunogenicity samples, did not have SARS-CoV-2 infection at pre-booster, did not have a major protocol deviation that impacted immune response, and had post-booster immunogenicity assessment at timepoint of primary interest (28 days post-Booster Dose).
b SPIKEVAX dosing was a single booster dose (25 mcg mRNA), Study 4.
c Per-Protocol Immunogenicity Subset for Study 1 included all subjects who had both baseline (pre-vaccination) and post-vaccination immunogenicity samples, did not have SARS-CoV-2 infection at baseline, did not have a major protocol deviation that impacted immune response, and had post-injection immunogenicity assessment at timepoint of primary interest (28 days post-Dose 2).
d SPIKEVAX dosing was a two-dose series (100 mcg mRNA per dose) 1 month apart, Study 1.
e Noninferiority is declared if the lower limit of the 2-sided 95% CI for the GMC Ratio is >0.667.
f Seroresponse is defined as ≥4-fold rise of pseudovirus neutralizing antibody concentration from baseline (pre-Dose 1 of primary series in Study 4 and Study 1), where baseline concentration < LLOQ is set to LLOQ for the analysis.
g 95% CI is calculated using the Clopper-Pearson method.
h 95% CI is calculated using the Miettinen-Nurminen (score) confidence limits.
i Noninferiority is declared if the lower limit of the 2-sided 95% CI for the percentage difference is
≥-10%.
Note: Antibody values < the lower limit of quantitation (LLOQ) are replaced by 0.5 × LLOQ. Values > the upper limit of quantitation (ULOQ) are replaced by the ULOQ if actual values are not available.

A descriptive analysis evaluated seroresponse rates using pre-booster neutralizing antibody concentration. The booster dose seroresponse rate, with seroresponse defined as at least a 4-fold rise relative to the pre-booster concentration for Study 4, was 93.4%. The difference in seroresponse rates in this post-hoc analysis was -5.9% (95% CI: -11.5%, -2.6%).

Immunogenicity of Single Dose (Bivalent Original and Omicron BA.1) in Vaccine-Experienced Infants and Children 6 Months Through 5 Years of Age (Study 6)

Study 6 is an ongoing open-label clinical trial that included a phase conducted in the United States in which participants 6 months through 5 years of age received a single booster dose of bivalent vaccine (Original and Omicron BA.1) (10 mcg mRNA per dose) at least 4 months after completion of a SPIKEVAX primary series (two doses 1 month apart) (NCT05436834). The primary immunogenicity analysis population included 319 booster dose participants in Study 6 and a subset of 590 participants 6 months through 5 years of age from Study 4 who had completed primary vaccination with two doses of SPIKEVAX (25 mcg mRNA per dose) 1 month apart. Study 4 and Study 6 participants included in the analysis population had no serologic or virologic evidence of SARS-CoV-2 infection prior to the first primary series dose and prior to the booster dose, respectively. Demographics in the subset of individuals 6 months through 5 years of age in this analysis were consistent with the overall demographics in this phase of Study 6. Among the bivalent vaccine (Original and Omicron BA.1) participants in the primary immunogenicity analysis population, the median age for receipt of the booster dose was 3 years (range 0.9-5).

The primary immunogenicity analyses of the GMC ratio and difference in seroresponse rates following the booster dose in Study 6 compared to following the primary series in Study 4 met the pre-defined immunobridging success criteria. Seroresponse for a participant was defined as achieving a ≥4-fold rise of neutralizing antibody concentration from baseline (before the first dose of the primary series in Study 6 and Study 4). These analyses are summarized in Table 36 and Table 37.

Table 36: Comparison of Geometric Mean Concentration in Participants 6 Months Through 5 Years of Age 28 Days After a Booster Dose (Study 6) vs 28 Days After Completion of the Primary Series (Study 4) – Per-Protocol Immunogenicity SARS-CoV-2 Negative Sets
Assaya | Study 6b; Bivalent Vaccine (Original and Omicron BA.1); Booster Dosec; GMCd; (95% CI) | Study 4e; SPIKEVAX; Primary Seriesf; GMCg; (95% CI) | GMC Ratio; (Study 6 / Study 4); (95% CI)d | Met Success Criteria
Omicron BA.1 | 805.2; (731.2, 886.8); N=316 | 66.6; (62.0, 71.6); N=567 | 12.1; (10.7, 13.6) | Yesg
Original SARS-CoV-2 (D614G) | 4754.7; (4346.9, 5200.7); N=316 | 1559.4; (1457.6, 1668.4); N=557 | 3.0; (2.7, 3.4) | Yesh
N=Number of participants with non-missing data at corresponding timepoint.
a Geometric mean concentration (GMC) was determined using a SARS-CoV-2 Spike-Pseudotyped Virus Neutralization Assay. Quantification of SARS-CoV-2 neutralizing antibodies utilizes a SARS-CoV-2 Reporter Virus Particles which express GFP for quantitative measurement of infection by counting the number of green fluorescent cells (assay readout [count] is Foci Forming Units [FFUs]). The serum antibody concentration (Ab[C]) of the neutralizing antibodies was determined by interpolating the mean of the replicate FFU values off the fitted reference standard curve (AU/mL).
b Per-Protocol Immunogenicity SARS-CoV-2 Negative Set included all subjects who had pre-booster and Day 29 neutralizing antibody data, had no major protocol deviations that impact key or critical data, and had no serologic or virologic evidence of SARS-CoV-2 infection prior to the booster dose.
c Bivalent vaccine (Original and Omicron BA.1) dosing was a single booster (10 mcg mRNA), Study 6.
d The log-transformed antibody levels were analyzed using an ANCOVA model with the group variable (participants in Study 6 and Study 4) as fixed variable. The resulting LS means, difference of LS, and 95% CI were back transformed to the original scale for presentation.
e Per-Protocol Immunogenicity SARS-CoV-2 Negative Set for Study 4 included all subjects who had both baseline (pre-vaccination) and post-vaccination immunogenicity samples, did not have SARS-CoV-2 infection at baseline, did not have a major protocol deviation that impacted immune response, and had post-injection immunogenicity assessment at timepoint of primary interest (28 days post-Dose 2).
f SPIKEVAX dosing was a two-dose series (25 mcg mRNA per dose) 1 month apart, Study 4.
g Superiority is declared if the lower limit of the 2-sided 95% CI for the GMC ratio is >1.
h Noninferiority is declared if the lower limit of the 2-sided 95% CI for the GMC ratio is >0.667.
Note: Antibody values < the lower limit of quantitation (LLOQ) are replaced by 0.5 × LLOQ. Values > the upper limit of quantitation (ULOQ) are replaced by the ULOQ if actual values are not available.

Table 37: Comparison of Seroresponse Rate in Participants 6 Months Through 5 Years of Age 28 Days After a Booster Dose (Study 6) vs 28 Days After Completion of the Primary Series (Study 4) – Per-Protocol Immunogenicity SARS-CoV-2 Negative Sets
Assay | Study 6a; Bivalent Vaccine (Original and Omicron BA.1); Booster Doseb; Seroresponsec; (95% CI)d | Study 4e; SPIKEVAX; Primary Seriesf; Seroresponsec; (95% CI)d | Difference in Seroresponse Rate; (Study 6-Study 4); % (95% CI)g | Met Success Criteria
Omicron BA.1 | 99.0; (97.2,99.8); N=312 | 84.9; (81.6, 87.7); N=562 | 14.2; (11.1, 17.5) | Yesh
Original SARS-CoV-2 (D614G) | 100; (98.8,100.0); N=312 | 99.5; (98.4, 99.9); N=548 | 0.5; (-0.7, 1.6) | Yesh
N=Number of participants with non-missing data at baseline (pre-Dose 1 of primary series) and the corresponding post-baseline timepoint.
a Per-Protocol Immunogenicity SARS-CoV-2 Negative Set included all subjects who had pre-booster and Day 29 neutralizing antibody data, had no major protocol deviations that impact key or critical data, and had no serologic or virologic evidence of SARS-CoV-2 infection prior to the booster dose.
b Bivalent vaccine (Original and Omicron BA.1) dosing was a single booster (10 mcg mRNA), Study 6.
c Seroresponse at a participant level was defined as a change from baseline (pre-Dose 1 of primary series) below the LLOQ to ≥4 x LLOQ, or at least a 4-fold rise if baseline was ≥LLOQ. For participants without pre-Dose 1 antibody level information and who had corresponding Day 29 post-booster assessment, seroresponse was defined as ≥4 x LLOQ for participants with negative SARS-CoV-2 status at their pre-Dose 1 of primary series, and these participants antibody levels were imputed as <LLOQ at pre-dose 1 of primary series. For participants who were without SARS-CoV-2 status information at pre-Dose 1 of primary series, their pre-booster SARS-CoV-2 status was used to impute their SARS-CoV-2 status at their pre-Dose 1 of primary series.
d 95% CI was calculated using the Clopper-Pearson method.
e Per-Protocol Immunogenicity SARS-CoV-2 Negative Set for Study 4 included all subjects who had both baseline (pre-vaccination) and post-vaccination immunogenicity samples, did not have SARS-CoV-2 infection at baseline, did not have a major protocol deviation that impacted immune response, and had post-injection immunogenicity assessment at timepoint of primary interest (28 days post-Dose 2).
f SPIKEVAX dosing was a two-dose series (25 mcg mRNA per dose) 1 month apart, Study 4.
g 95% CI was calculated using the Miettinen-Nurminen score method.
h Noninferiority is declared if the lower limit of the 2-sided 95% CI for the percentage difference is ≥-5% for BA.1 strain and ≥-10 % for original strain, respectively.

A descriptive analysis evaluated seroresponse rates using pre-booster neutralizing antibody concentration as baseline. Seroresponse rate was defined as at least a 4-fold rise relative to the pre-booster concentration for Study 6. For the Omicron BA.1 assay, the seroresponse rate using pre-booster baseline was 96.5 % (95% CI: 93.8%, 98.2%) and the difference from Study 4 SPIKEVAX primary series seroresponse rate was 11.6 % (95% CI: 7.9%, 15.2%). For the Original SARS-CoV-2 (D614G) assay, the seroresponse using pre-booster baseline was 93.7% (95% CI: 90.4%, 96.1%) and the difference from Study 4 SPIKEVAX primary series seroresponse rate was -5.8% (95% CI: -9.1%, -3.5%).

15 REFERENCES

1. Jain SS, Anderson SA, Steele JM, et al. Cardiac manifestations and outcomes of COVID-19 vaccine-associated myocarditis in the young in the USA: longitudinal results from the Myocarditis After COVID Vaccination (MACiV) multicenter study. Lancet. 2024;76:1-13. https://doi.org/10.1016/j.eclinm.2024.102809
2. Free RJ, Patel K, Taylor CA, et al. Hospitalization for COVID-19 and risk factors for severe disease among children: 2022-2024. Pediatrics. Published online July 3, 2025. doi:10.1542/peds.2025-072788

16 HOW SUPPLIED/STORAGE AND HANDLING

SPIKEVAX is supplied as follows:

For 6 months through 11 years of age

NDC 80777-113-87 Carton of 2 single-dose pre-filled syringes, each syringe containing 1 dose of 0.25 mL (NDC 80777-113-09)
NDC 80777-113-80 Carton of 10 single-dose pre-filled syringes, each syringe containing 1 dose of 0.25 mL (NDC 80777-113-09)

For 12 years of age and older

NDC 80777-112-88 Carton of 2 single-dose pre-filled syringes, each syringe containing 1 dose of 0.5 mL (NDC 80777-112-01)
NDC 80777-112-96 Carton of 10 single-dose pre-filled syringes, each syringe containing 1 dose of 0.5 mL (NDC 80777-112-01)

NDC 80777-112-93 Carton of 10 single-dose pre-filled syringes, each syringe containing 1 dose of 0.5 mL (NDC 80777-112-01). Each carton contains 5 blisters, and each blister contains two syringes. Use one syringe per dose.

During storage, minimize exposure to room light, and avoid exposure to direct sunlight and ultraviolet light.

Storage

Store frozen between -50°C to -15°C (-58°F to 5°F).

After thawing, SPIKEVAX may be stored refrigerated between 2°C to 8°C (36°F to 46°F) for up to 60 days or up to the expiration date printed on the carton, whichever comes first.

After thawing, SPIKEVAX may be stored between 8°C to 25°C (46°F to 77°F) for up to 12 hours.

Do not refreeze once thawed.

Thawed syringes can be handled in room light conditions.
Transportation of Thawed Syringes at 2°C to 8°C (36°F to 46°F)
Thawed pre-filled syringes can be transported at 2°C to 8°C (36°F to 46°F) in shipping containers qualified to maintain 2°C to 8°C (36°F to 46°F). Once thawed and transported at 2°C to 8°C (36°F to 46°F), pre-filled syringes should not be refrozen and should be stored at 2°C to 8°C (36°F to 46°F) until use.

17 PATIENT COUNSELING INFORMATION

Advise the vaccine recipient or caregiver to read the FDA-approved patient labeling.

Inform the vaccine recipient or caregiver of the potential benefits and risks of vaccination with SPIKEVAX.

Instruct the vaccine recipient or caregiver to report any adverse events to their healthcare provider or to the Vaccine Adverse Event Reporting System at 1-800-822-7967 and https://vaers.hhs.gov.
Manufactured for:
Moderna US, Inc.
Princeton, NJ 08540
©2025 ModernaTX, Inc. All rights reserved.
SPIKEVAX is a trademark of ModernaTX, Inc.
Patent(s): www.modernatx.com/patents
US Govt. License No. 2256
Revised: 8/2025

Information for Recipients and Caregivers

SPIKEVAX (pronounced SPĪK-văx)
(COVID-19 Vaccine, mRNA)
(2025-2026 Formula)

Please read this information sheet before getting SPIKEVAX. This summary is not intended to take the place of talking with your or your child’s healthcare provider. If you have questions or would like more information, please talk with your or your child’s healthcare provider.

What is SPIKEVAX?

SPIKEVAX is a vaccine to protect against COVID-19. SPIKEVAX is for people who are:

- 65 years of age and older, or
- 6 months through 64 years of age at high risk for severe COVID-19.

Vaccination with SPIKEVAX may not protect all people who receive the vaccine.

SPIKEVAX does not contain SARS-CoV-2, the virus that causes COVID-19. SPIKEVAX cannot give you or your child COVID-19.

Who should not get SPIKEVAX?

You or your child should not get SPIKEVAX if you or your child had:

- a severe allergic reaction after a previous dose of SPIKEVAX or a Moderna COVID-19 vaccine
- a severe allergic reaction to any ingredient of this vaccine (see What are the ingredients in SPIKEVAX?)

What should I tell the healthcare provider?

Tell the healthcare provider about all of your or your child’s medical conditions, including if you or your child:

- have any allergies
- had a severe allergic reaction after receiving a previous dose of any COVID-19 vaccine
- have had myocarditis (inflammation of the heart muscle) or pericarditis (inflammation of the lining outside the heart)
- have a fever
- have a bleeding disorder or are on a blood thinner
- are immunocompromised or are on a medicine that affects your immune system
- are pregnant or plan to become pregnant
- are breastfeeding
- have received any other COVID-19 vaccine
- have ever fainted in association with an injection

How is SPIKEVAX given?

SPIKEVAX is given as an injection into the muscle.

What are the risks of SPIKEVAX?

Severe allergic reactions have occurred in some people who have received SPIKEVAX and Moderna COVID-19 vaccines. There is a very small chance that SPIKEVAX could cause a severe allergic reaction. A severe allergic reaction would usually occur within a few minutes to 1 hour after getting a dose of SPIKEVAX. For this reason, the healthcare provider may ask you or your child to stay for a short time at the place where you or your child received the vaccine. Signs of a severe allergic reaction can include:

- Trouble breathing
- Swelling of your face and throat
- A fast heartbeat
- A rash all over your body
- Dizziness and weakness

Myocarditis (inflammation of the heart muscle) and pericarditis (inflammation of the lining outside the heart) have occurred in some people who have received mRNA COVID-19 vaccines, including SPIKEVAX and Moderna COVID-19 vaccines. Myocarditis and pericarditis following administration of mRNA COVID-19 vaccines have occurred most commonly in males 12 years through 24 years of age. In most of these people, symptoms began within a week following vaccination. Based on available data, estimated rates of myocarditis and/or pericarditis from 1 through 7 days after getting a dose of the 2023-2024 Formula of mRNA COVID-19 vaccines were approximately 8 cases per million doses in people 6 months through 64 years of age and approximately 27 cases per million doses in males 12 years through 24 years of age.

In most people who have had myocarditis or pericarditis after receiving an mRNA COVID-19 vaccine, symptoms have gone away a few days after receiving treatment with medicines used to reduce inflammation.

In a study, follow-up information was collected on people who developed myocarditis after receiving the original formula of a COVID-19 vaccine; most people had received an mRNA COVID-19 vaccine. Some people in the study reported having heart symptoms approximately 3 months after developing myocarditis. Some people in the study had heart MRIs (scans that show detailed images of the heart muscle) initially after developing myocarditis and again approximately 5 months later. The initial and follow-up heart MRIs commonly showed signs of injury to the heart muscle, with improvement over time in most people. It is not known if these heart MRI findings might predict long-term heart effects of myocarditis. Studies are underway to find out if there are long-term heart effects in people who have had myocarditis after receiving an mRNA COVID-19 vaccine.

You should seek medical attention right away if you or your child has any of the following symptoms after receiving SPIKEVAX, particularly during the 2 weeks after receiving a dose of the vaccine:

- Chest pain
- Shortness of breath
- Feelings of having a fast-beating, fluttering, or pounding heart

These could be symptoms of myocarditis or pericarditis.

Additional symptoms, particularly in children, may include:

- Fainting
- Unusual and persistent irritability
- Unusual and persistent poor feeding
- Unusual and persistent fatigue or lack of energy
- Persistent vomiting
- Persistent pain in the abdomen
- Unusual and persistent cool, pale skin

Side effects that have been reported in clinical trials with SPIKEVAX and Moderna COVID-19 vaccines include:

- Injection site reactions: pain, tenderness and swelling of the lymph nodes in the same arm of the injection or in the groin, swelling (hardness), and redness
- General side effects: fatigue, headache, muscle pain, joint pain, chills, nausea and vomiting, fever, rash, irritability/crying, sleepiness, and loss of appetite

Other side effects that have been reported include:

- Severe allergic reactions
- Urticaria (itchy rash/hives)
- Myocarditis (inflammation of the heart muscle)
- Pericarditis (inflammation of the lining outside the heart)
- Fainting in association with injection of the vaccine
- Febrile seizures (convulsions during a fever)

These may not be all of the possible side effects of SPIKEVAX. Ask your healthcare provider about any side effects that concern you. You may report side effects to the Vaccine Adverse Event Reporting System (VAERS) at 1-800-822-7967 or https://vaers.hhs.gov.

What if I am or my child is pregnant or breastfeeding?

If you are or your child is pregnant or breastfeeding, discuss your options with your or your child’s healthcare provider.

What are the ingredients in SPIKEVAX?

SPIKEVAX contains the following ingredients:

- messenger ribonucleic acid (mRNA)
- lipids (SM-102, polyethylene glycol [PEG] 2000 dimyristoyl glycerol [DMG], cholesterol, and 1,2-distearoyl-sn-glycero-3-phosphocholine [DSPC])
- tromethamine
- tromethamine hydrochloride
- acetic acid
- sodium acetate trihydrate
- sucrose

SPIKEVAX does not contain preservatives.

If you would like more information, talk to your healthcare provider or visit www.spikevax.com or call 1-866-MODERNA (1-866-663-3762).

Manufactured for:
Moderna US, Inc.
Princeton, NJ 08540

©2025 ModernaTX, Inc. All rights reserved.
SPIKEVAX is a trademark of ModernaTX, Inc.
Patent(s): www.modernatx.com/patents
Revised: August 2025

Package/Label Principal Display Panel

COVID-19 Vaccine, mRNA

Spikevax

2025-2026 Formula

0.5 mL Single Dose

NDC 80777-112-01

Rx Only

For IM Use

Mfd. for: Moderna US, Inc.

Package/Label Principal Display Panel

NDC 80777-112-96

Moderna

Rx Only

COVID-19 Vaccine, mRNA

Spikevax

2025-2026 Formula

Injectable Suspension, for Intramuscular Use

10 Single-Dose Pre-Filled Syringes

Each dose is 0.5 mL

For 65 years and older

For 12 years through 64 years at high risk for severe COVID-19

Package/Label Principal Display Panel

NDC 80777-112-93

Moderna

Rx Only

COVID-19 Vaccine, mRNA

Spikevax

2025-2026 Formula

Injectable Suspension, for Intramuscular Use

10 Single-Dose Pre-Filled Syringes

Each dose is 0.5 mL

For 65 years and older

For 12 years through 64 years at high risk for severe COVID-19

Package/Label Principal Display Panel

NDC 80777-112-88

Moderna

Rx Only

COVID-19 Vaccine, mRNA

Spikevax

2025-2026 Formula

Injectable Suspension, for Intramuscular Use

2 Single-Dose Pre-Filled Syringes

Each dose is 0.5 mL

For 65 years and older

For 12 years through 64 years at high risk for severe COVID-19

Package/Label Principal Display Panel

COVID-19 Vaccine, mRNA

Spikevax

2025-2026 Formula

0.25 mL Single Dose

NDC 80777-113-09

Rx Only

For IM Use

Mfd. for: Moderna US, Inc.

Package/Label Principal Display Panel

NDC 80777-113-80

Moderna

Rx Only

COVID-19 Vaccine, mRNA

Spikevax

2025-2026 Formula

Injectable Suspension, for Intramuscular Use

10 Single-Dose Pre-Filled Syringes

Each dose is 0.25 mL

For 6 months through 11 years at high risk for severe COVID-19

Package/Label Principal Display Panel

NDC 80777-113-87

Moderna

Rx Only

COVID-19 Vaccine, mRNA

Spikevax

2025-2026 Formula

Injectable Suspension, for Intramuscular Use

2 Single-Dose Pre-Filled Syringes

Each dose is 0.25 mL

For 6 months through 11 years at high risk for severe COVID-19